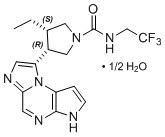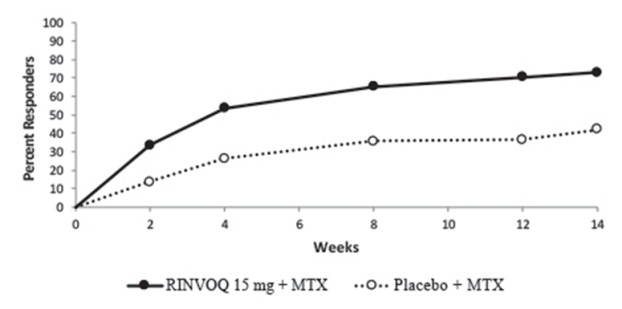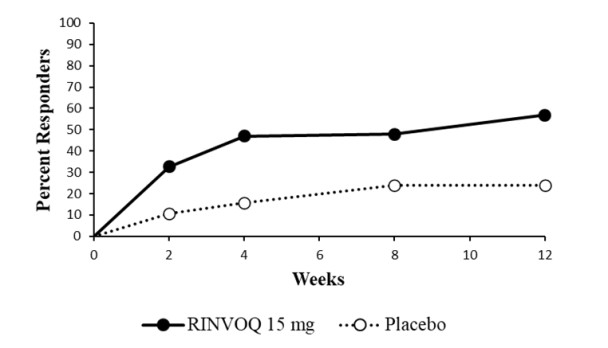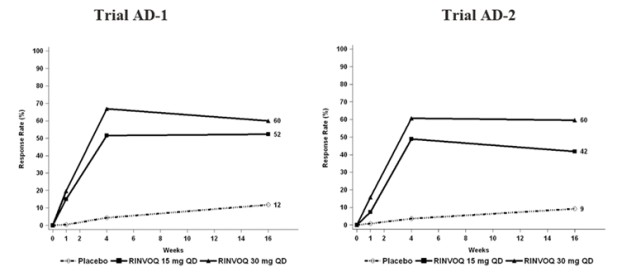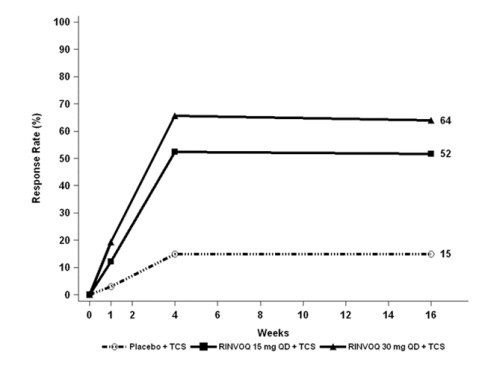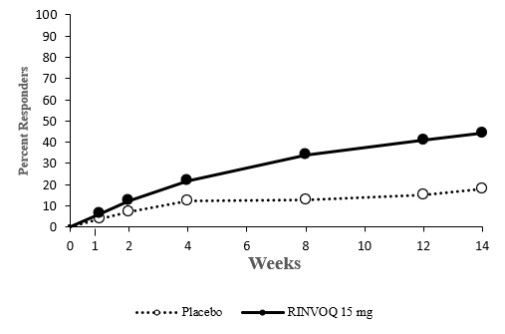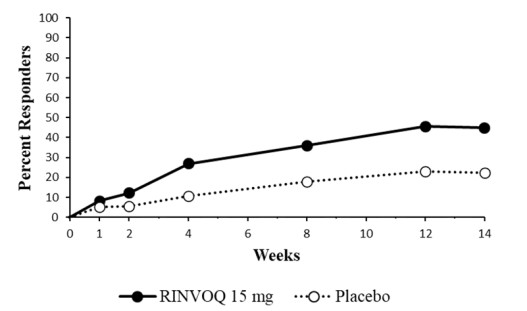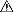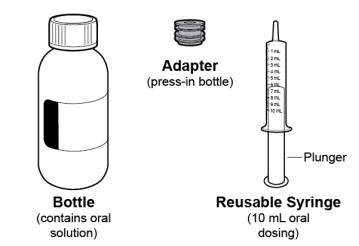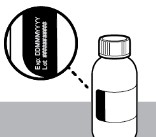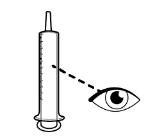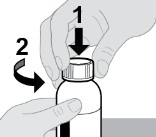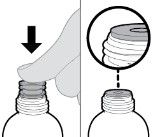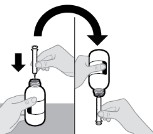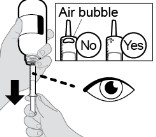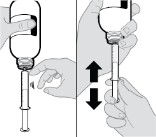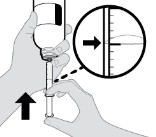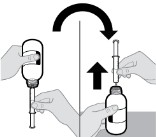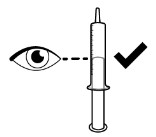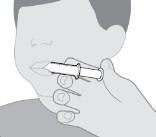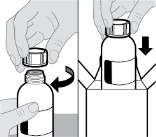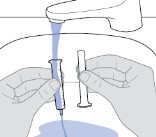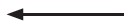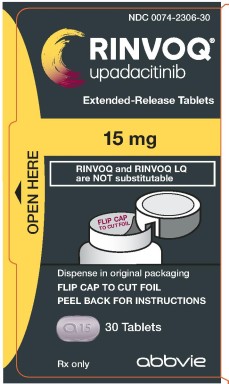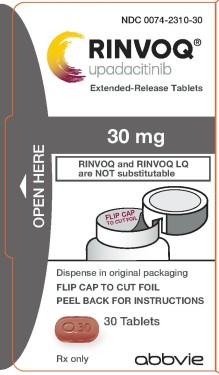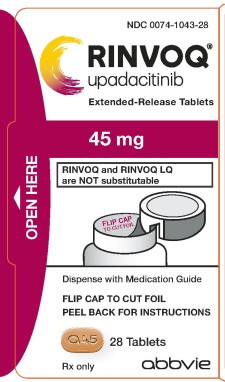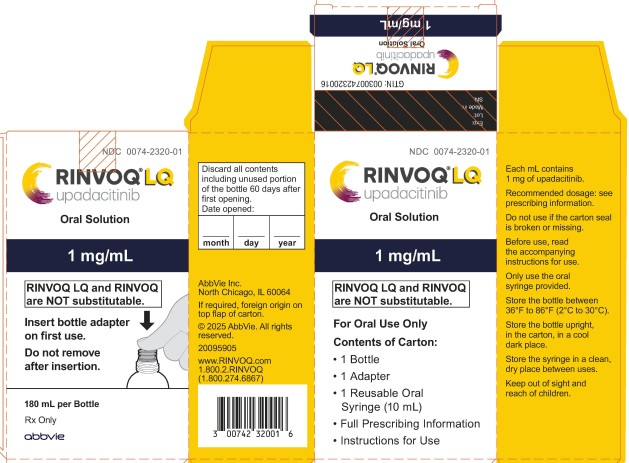 DRUG LABEL: Rinvoq
NDC: 0074-2306 | Form: TABLET, EXTENDED RELEASE
Manufacturer: AbbVie Inc.
Category: prescription | Type: HUMAN PRESCRIPTION DRUG LABEL
Date: 20251010

ACTIVE INGREDIENTS: upadacitinib 15 mg/1 1
INACTIVE INGREDIENTS: SILICON DIOXIDE; FERROSOFERRIC OXIDE; HYPROMELLOSE, UNSPECIFIED; FERRIC OXIDE RED; MAGNESIUM STEARATE; MANNITOL; MICROCRYSTALLINE CELLULOSE; POLYVINYL ALCOHOL, UNSPECIFIED; POLYETHYLENE GLYCOL, UNSPECIFIED; TALC; TARTARIC ACID; TITANIUM DIOXIDE

HIGHLIGHTS OF PRESCRIBING INFORMATION

These highlights do not include all the information needed to use RINVOQ/RINVOQ LQ safely and effectively. See full prescribing information for RINVOQ/RINVOQ LQ.
RINVOQ® (upadacitinib) extended-release tablets, for oral use RINVOQ® LQ (upadacitinib) oral solution
Initial U.S. Approval: 2019

RECENT MAJOR CHANGES

Boxed Warning | 4/2025
Indications and Usage (1.9) | 4/2025
Indications and Usage (1.4, 1.5) | 10/2025
Dosage and Administration (2.11, 2.12, 2.13) | 4/2025
Warnings and Precautions (5.5) | 4/2025

WARNING: SERIOUS INFECTIONS, MORTALITY, MALIGNANCY, MAJOR ADVERSE CARDIOVASCULAR EVENTS, and THROMBOSIS

WARNING: SERIOUS INFECTIONS, MORTALITY, MALIGNANCY, MAJOR ADVERSE CARDIOVASCULAR EVENTS (MACE), and THROMBOSIS

See full prescribing information for complete boxed warning.

- Increased risk of serious bacterial, fungal, viral, and opportunistic infections leading to hospitalization or death, including tuberculosis (TB). Interrupt treatment with RINVOQ/RINVOQ LQ if serious infection occurs until the infection is controlled. Test for latent TB before and during therapy; treat latent TB prior to use. Monitor all patients for active TB during treatment, even patients with initial negative, latent TB test. (5.1)
- Higher rate of all-cause mortality, including sudden cardiovascular death with another Janus kinase (JAK) inhibitor vs. tumor necrosis factor (TNF) blockers in rheumatoid arthritis (RA) patients. (5.2)
- Malignancies have occurred in patients treated with RINVOQ. Higher rate of lymphomas and lung cancers with another JAK inhibitor vs. TNF blockers in RA patients. (5.3)
- Higher rate of MACE (defined as cardiovascular death, myocardial infarction, and stroke) with another JAK inhibitor vs. TNF blockers in RA patients. (5.4)
- Thrombosis has occurred in patients treated with RINVOQ. Increased incidence of pulmonary embolism, venous and arterial thrombosis with another JAK inhibitor vs. TNF blockers. (5.5)

1 INDICATIONS AND USAGE

RINVOQ/RINVOQ LQ is a Janus kinase (JAK) inhibitor.

- RINVOQ is indicated for the treatment of adults with moderately to severely active rheumatoid arthritis who have had an inadequate response or intolerance to one or more TNF blockers. (1.1)
  Limitations of Use
  RINVOQ is not recommended for use in combination with other JAK inhibitors, biologic DMARDs, or with potent immunosuppressants such as azathioprine and cyclosporine. (1.1)
- RINVOQ/RINVOQ LQ is indicated for the treatment of adults and pediatric patients 2 years of age and older with active psoriatic arthritis who have had an inadequate response or intolerance to one or more TNF blockers. (1.2)
  Limitations of Use
  RINVOQ/RINVOQ LQ is not recommended for use in combination with other JAK inhibitors, biologic DMARDs, or with potent immunosuppressants such as azathioprine and cyclosporine. (1.2)
- RINVOQ is indicated for the treatment of adults and pediatric patients 12 years of age and older with refractory, moderate to severe atopic dermatitis whose disease is not adequately controlled with other systemic drug products, including biologics, or when use of those therapies are inadvisable. (1.3)
  Limitations of Use
  RINVOQ is not recommended for use in combination with other JAK inhibitors, biologic immunomodulators, or with other immunosuppressants. (1.3)
- RINVOQ is indicated for the treatment of adults with moderately to severely active ulcerative colitis (UC) who have had an inadequate response or intolerance to one or more TNF blockers. If TNF blockers are clinically inadvisable, patients should have received at least one approved systemic therapy prior to use of RINVOQ. (1.4)
  Limitations of Use
  RINVOQ is not recommended for use in combination with other JAK inhibitors, biological therapies for UC, or with potent immunosuppressants such as azathioprine and cyclosporine. (1.4)
- RINVOQ is indicated for the treatment of adults with moderately to severely active Crohn’s disease (CD) who have had an inadequate response or intolerance to one or more TNF blockers. If TNF blockers are clinically inadvisable, patients should have received at least one approved systemic therapy prior to use of RINVOQ. (1.5)
  Limitations of Use
  RINVOQ is not recommended for use in combination with other JAK inhibitors, biological therapies for CD, or with potent immunosuppressants such as azathioprine and cyclosporine. (1.5)
- RINVOQ is indicated for the treatment of adults with active ankylosing spondylitis who have had an inadequate response or intolerance to one or more TNF blockers. (1.6)
  Limitations of Use
  RINVOQ is not recommended for use in combination with other JAK inhibitors, biologic DMARDs, or with potent immunosuppressants such as azathioprine and cyclosporine. (1.6)
- RINVOQ is indicated for the treatment of adults with active non-radiographic axial spondyloarthritis with objective signs of inflammation who have had an inadequate response or intolerance to TNF blocker therapy. (1.7)
  Limitations of Use
  RINVOQ is not recommended for use in combination with other JAK inhibitors, biologic DMARDs, or with potent immunosuppressants such as azathioprine and cyclosporine. (1.7)
- RINVOQ/RINVOQ LQ is indicated for the treatment of patients 2 years of age and older with active polyarticular juvenile idiopathic arthritis who have had an inadequate response or intolerance to one or more TNF blockers. (1.8)
  Limitations of Use
  RINVOQ/RINVOQ LQ is not recommended for use in combination with other JAK inhibitors, biologic DMARDs, or with potent immunosuppressants such as azathioprine and cyclosporine. (1.8)
- RINVOQ is indicated for the treatment of adults with giant cell arteritis (1.9)
  Limitations of Use
  RINVOQ is not recommended for use in combination with other JAK inhibitors, biologic DMARDs, or with potent immunosuppressants such as azathioprine and cyclosporine. (1.9)

2 DOSAGE AND ADMINISTRATION

- RINVOQ LQ oral solution is not substitutable with RINVOQ extended-release tablets (2.2, 2.10).
- Changes between RINVOQ LQ oral solution and RINVOQ extended-release tablets should be made by the healthcare provider.
- Prior to treatment update immunizations and consider evaluating for active and latent tuberculosis, viral hepatitis, hepatic function, and pregnancy status (2.1)
- Avoid initiation or interrupt RINVOQ/RINVOQ LQ if absolute lymphocyte count is less than 500 cells/mm^3, absolute neutrophil count is less than 1000 cells/mm^3, or hemoglobin level is less than 8 g/dL. (2.1, 2.14)

Rheumatoid Arthritis, Ankylosing Spondylitis, and Non-radiographic Axial Spondyloarthritis

- Adults: The recommended dosage of RINVOQ is 15 mg once daily. (2.3, 2.8, 2.9)

Psoriatic Arthritis

- Pediatric Patients 2 to less than 18 Years of Age Weighing at Least 10 kg: The recommended dosage is based on body weight (2.4)
- Adults: The recommended dosage of RINVOQ is 15 mg once daily. (2.4)

Atopic Dermatitis

- Pediatric Patients 12 Years of Age and Older Weighing at Least 40 kg and Adults Less Than 65 Years of Age: Initiate treatment with RINVOQ 15 mg orally once daily. If an adequate response is not achieved, consider increasing the dosage to 30 mg orally once daily. (2.5)
- Adults 65 Years of Age and Older: Recommended dosage of RINVOQ is 15 mg once daily. (2.5)
- Severe Renal Impairment: Recommended dosage of RINVOQ is 15 mg once daily. (2.12)

Ulcerative Colitis

- Adults: The recommended induction dosage of RINVOQ is 45 mg once daily for 8 weeks. The recommended maintenance dosage of RINVOQ is 15 mg once daily. A maintenance dosage of 30 mg once daily may be considered for patients with refractory, severe, or extensive disease. Discontinue RINVOQ if adequate therapeutic response is not achieved with the 30 mg dosage. Use the lowest effective dosage needed to maintain response. (2.6)
- See the Full Prescribing Information for the recommended dosage in patients with renal or hepatic impairment and for dosage modification due to drug interactions. (2.12, 2.13)

Crohn’s Disease

- Adults: The recommended induction dosage of RINVOQ is 45 mg once daily for 12 weeks. The recommended maintenance dosage of RINVOQ is 15 mg once daily. A maintenance dosage of 30 mg once daily may be considered for patients with refractory, severe, or extensive disease. Discontinue RINVOQ if an adequate therapeutic response is not achieved with the 30 mg dosage. Use the lowest effective dosage needed to maintain response. (2.7)
- See the Full Prescribing Information for the recommended dosage in patients with renal or hepatic impairment and for dosage modification due to drug interactions. (2.12, 2.13)

Polyarticular Juvenile Idiopathic Arthritis

- The recommended dosage is based on body weight (2.10)

Giant Cell Arteritis

- The recommended dosage of RINVOQ is 15 mg once daily in combination with a tapering course of corticosteroids. RINVOQ 15 mg once daily can be used as monotherapy following discontinuation of corticosteroids (2.11)

3 DOSAGE FORMS AND STRENGTHS

- RINVOQ extended-release tablets: 15 mg, 30 mg, and 45 mg (3)
- RINVOQ LQ oral solution: 1 mg/mL (3)

4 CONTRAINDICATIONS

Known hypersensitivity to upadacitinib or any of the excipients in RINVOQ/RINVOQ LQ. (4, 5.6)

5 WARNINGS AND PRECAUTIONS

- Serious Infections: Avoid use in patients with active, serious infection, including localized infections. (5.1)
- Hypersensitivity: Serious hypersensitivity reactions (e.g., anaphylaxis) have been reported. Discontinue if a serious hypersensitivity reaction occurs. (5.6)
- Gastrointestinal (GI) Perforations: Monitor patients at risk for GI perforations and promptly evaluate patients with symptoms. (5.7)
- Laboratory Abnormalities: Monitoring recommended due to potential changes in lymphocytes, neutrophils, hemoglobin, liver enzymes and lipids. (5.8)
- Embryo-Fetal Toxicity: May cause fetal harm based on animal studies. Advise female patients of reproductive potential of the potential risk to a fetus and to use effective contraception. (5.9, 8.1, 8.3)
- Vaccinations: Avoid use with live vaccines. (5.10)
- Medication Residue in Stool: Observed in stool or ostomy output in patients with shortened GI transit times. Monitor patients clinically and consider alternative treatment if inadequate therapeutic response. (5.11)

6 ADVERSE REACTIONS

- Rheumatoid arthritis, psoriatic arthritis, ankylosing spondylitis, and non-radiographic axial spondyloarthritis: Adverse reactions (≥ 1%) were: upper respiratory tract infections, herpes zoster, herpes simplex, bronchitis, nausea, cough, pyrexia, acne, and headache. (6.1)
- Giant cell arteritis: Adverse reactions (≥ 5%) are upper respiratory tract infections, headache, fatigue, peripheral edema, cough, anemia, rash, herpes zoster, and nausea. (6.1)
- Atopic dermatitis: Adverse reactions (≥ 1%) are: upper respiratory tract infections, acne, herpes simplex, headache, blood creatine phosphokinase increased, cough, hypersensitivity, folliculitis, nausea, abdominal pain, pyrexia, increased weight, herpes zoster, influenza, fatigue, neutropenia, myalgia, and influenza like illness. (6.1)
- Ulcerative colitis: Adverse reactions (≥ 5%) reported during induction or maintenance are: upper respiratory tract infections, increased blood creatine phosphokinase, acne, neutropenia, elevated liver enzymes, pyrexia, and rash. (6.1)
- Crohn’s disease: Adverse reactions (≥ 5%) reported during induction or maintenance are: upper respiratory tract infections, anemia, pyrexia, acne, herpes zoster, and headache. (6.1)

To report SUSPECTED ADVERSE REACTIONS, contact AbbVie Inc. at 1-800-633-9110 or FDA at 1-800-FDA-1088 or www.fda.gov/medwatch.

7 DRUG INTERACTIONS

- Strong CYP3A4 Inhibitors: See the Full Prescribing Information for dosage modification for patients with atopic dermatitis, ulcerative colitis, and Crohn’s disease. (2.13, 7.1)
- Strong CYP3A4 Inducers: Coadministration of RINVOQ/RINVOQ LQ with strong CYP3A4 inducers is not recommended. (7.2)

8 USE IN SPECIFIC POPULATIONS

- Lactation: Advise not to breastfeed. (8.2)
- Hepatic Impairment: RINVOQ/RINVOQ LQ is not recommended in patients with severe hepatic impairment. (8.7)

FULL PRESCRIBING INFORMATION

WARNING: SERIOUS INFECTIONS, MORTALITY, MALIGNANCY, MAJOR ADVERSE CARDIOVASCULAR EVENTS, and THROMBOSIS

SERIOUS INFECTIONS

Patients treated with RINVOQ/RINVOQ LQ are at increased risk for developing serious infections that may lead to hospitalization or death [see Warnings and Precautions (5.1), Adverse Reactions (6.1)]. Most patients who developed these infections were taking concomitant immunosuppressants such as methotrexate or corticosteroids.

If a serious infection develops, interrupt RINVOQ/RINVOQ LQ until the infection is controlled.

Reported infections include:

- Active tuberculosis, which may present with pulmonary or extrapulmonary disease. Patients should be tested for latent tuberculosis before RINVOQ/RINVOQ LQ use and during therapy. Treatment for latent infection should be considered prior to RINVOQ/RINVOQ LQ use.
- Invasive fungal infections, including cryptococcosis and pneumocystosis.
- Bacterial, viral, including herpes zoster, and other infections due to opportunistic pathogens.

The risks and benefits of treatment with RINVOQ/RINVOQ LQ should be carefully considered prior to initiating therapy in patients with chronic or recurrent infection.

Patients should be closely monitored for the development of signs and symptoms of infection during and after treatment with RINVOQ/RINVOQ LQ, including the possible development of tuberculosis in patients who tested negative for latent tuberculosis infection prior to initiating therapy [see Warnings and Precautions (5.1)].

MORTALITY

In a large, randomized, postmarketing safety study in rheumatoid arthritis (RA) patients 50 years of age and older with at least one cardiovascular risk factor comparing another Janus kinase (JAK) inhibitor to tumor necrosis factor (TNF) blockers, a higher rate of all-cause mortality, including sudden cardiovascular death, was observed with the JAK inhibitor [see Warnings and Precautions (5.2)].

MALIGNANCIES

Lymphoma and other malignancies have been observed in patients treated with RINVOQ. In RA patients treated with another JAK inhibitor, a higher rate of malignancies (excluding non-melanoma skin cancer (NMSC)) was observed when compared with TNF blockers. Patients who are current or past smokers are at additional increased risk [see Warnings and Precautions (5.3)].

MAJOR ADVERSE CARDIOVASCULAR EVENTS

In RA patients 50 years of age and older with at least one cardiovascular risk factor treated with another JAK inhibitor, a higher rate of major adverse cardiovascular events (MACE) (defined as cardiovascular death, myocardial infarction, and stroke), was observed when compared with TNF blockers. Patients who are current or past smokers are at additional increased risk. Discontinue RINVOQ/RINVOQ LQ in patients that have experienced a myocardial infarction or stroke [see Warnings and Precautions (5.4)].

THROMBOSIS

Thromboses, including deep venous thrombosis, pulmonary embolism, and arterial thrombosis, have occurred in patients treated for inflammatory conditions with JAK inhibitors, including RINVOQ. Many of these adverse events were serious and some resulted in death. In RA patients 50 years of age and older with at least one cardiovascular risk factor treated with another JAK inhibitor, a higher rate of thrombosis was observed when compared with TNF blockers. Avoid RINVOQ/RINVOQ LQ in patients at risk. Patients with symptoms of thrombosis should discontinue RINVOQ/RINVOQ LQ and be promptly evaluated [see Warnings and Precautions (5.5)].

1 INDICATIONS AND USAGE

1.1 Rheumatoid Arthritis

RINVOQ® is indicated for the treatment of adults with moderately to severely active rheumatoid arthritis who have had an inadequate response or intolerance to one or more TNF blockers.

- Limitations of Use: RINVOQ is not recommended for use in combination with other JAK inhibitors, biologic disease-modifying antirheumatic drugs (DMARDs), or with potent immunosuppressants such as azathioprine and cyclosporine.

1.2 Psoriatic Arthritis

RINVOQ/RINVOQ LQ is indicated for the treatment of adults and pediatric patients 2 years of age and older with active psoriatic arthritis who have had an inadequate response or intolerance to one or more TNF blockers.

- Limitations of Use: RINVOQ/RINVOQ LQ is not recommended for use in combination with other JAK inhibitors, biologic DMARDs, or with potent immunosuppressants such as azathioprine and cyclosporine.

1.3 Atopic Dermatitis

RINVOQ is indicated for the treatment of adults and pediatric patients 12 years of age and older with refractory, moderate to severe atopic dermatitis whose disease is not adequately controlled with other systemic drug products, including biologics, or when use of those therapies are inadvisable.

- Limitations of Use: RINVOQ is not recommended for use in combination with other JAK inhibitors, biologic immunomodulators, or with other immunosuppressants.

1.4 Ulcerative Colitis

RINVOQ is indicated for the treatment of adult patients with moderately to severely active ulcerative colitis (UC) who have had an inadequate response or intolerance to one or more TNF blockers. If TNF blockers are clinically inadvisable, patients should have received at least one approved systemic therapy prior to use of RINVOQ.

- Limitations of Use: RINVOQ is not recommended for use in combination with other JAK inhibitors, biological therapies for UC, or with potent immunosuppressants such as azathioprine and cyclosporine.

1.5 Crohn’s Disease

RINVOQ is indicated for the treatment of adult patients with moderately to severely active Crohn’s disease (CD) who have had an inadequate response or intolerance to one or more TNF blockers. If TNF blockers are clinically inadvisable, patients should have received at least one approved systemic therapy prior to use of RINVOQ.

- Limitations of Use: RINVOQ is not recommended for use in combination with other JAK inhibitors, biological therapies for CD, or with potent immunosuppressants such as azathioprine and cyclosporine.

1.6 Ankylosing Spondylitis

RINVOQ is indicated for the treatment of adults with active ankylosing spondylitis who have had an inadequate response or intolerance to one or more TNF blockers.

- Limitations of Use: RINVOQ is not recommended for use in combination with other JAK inhibitors, biologic DMARDs, or with potent immunosuppressants such as azathioprine and cyclosporine.

1.7 Non-radiographic Axial Spondyloarthritis

RINVOQ is indicated for the treatment of adults with active non-radiographic axial spondyloarthritis with objective signs of inflammation who have had an inadequate response or intolerance to TNF blocker therapy.

- Limitations of Use: RINVOQ is not recommended for use in combination with other JAK inhibitors, biologic DMARDs, or with potent immunosuppressants such as azathioprine and cyclosporine.

1.8 Polyarticular Juvenile Idiopathic Arthritis

RINVOQ/RINVOQ LQ is indicated for the treatment of patients 2 years of age and older with active polyarticular juvenile idiopathic arthritis (pJIA) who have had an inadequate response or intolerance to one or more TNF blockers.

- Limitations of Use: RINVOQ/RINVOQ LQ is not recommended for use in combination with other JAK inhibitors, biologic DMARDs, or with potent immunosuppressants such as azathioprine and cyclosporine.

1.9 Giant Cell Arteritis

RINVOQ is indicated for the treatment of adults with giant cell arteritis.

- Limitations of Use: RINVOQ is not recommended for use in combination with other JAK inhibitors, biologic DMARDs, or with potent immunosuppressants such as azathioprine and cyclosporine.

2 DOSAGE AND ADMINISTRATION

2.1 Recommended Evaluations and Immunizations Prior to Treatment Initiation

Prior to RINVOQ/RINVOQ LQ treatment initiation, consider performing the following evaluations:

- Active and latent tuberculosis (TB) infection evaluation - If positive, treat for TB prior to RINVOQ/RINVOQ LQ use [see Warnings and Precautions (5.1)].
- Viral hepatitis screening in accordance with clinical guidelines – RINVOQ/RINVOQ LQ initiation is not recommended in patients with active hepatitis B or hepatitis C [see Warnings and Precautions (5.1)].
- A complete blood count – RINVOQ/RINVOQ LQ initiation is not recommended in patients with an absolute lymphocyte count less than 500 cells/mm^3, absolute neutrophil count less than 1000 cells/mm^3, or hemoglobin level less than 8 g/dL [see Dosage and Administration (2.14) and Warnings and Precautions (5.8)].
- Baseline hepatic function: RINVOQ/RINVOQ LQ initiation is not recommended for patients with severe hepatic impairment (Child-Pugh C) [see Use in Specific Populations (8.7) and Clinical Pharmacology (12.3)].
- Pregnancy Status: Verify the pregnancy status of females of reproductive potential prior to starting treatment [see Warnings and Precautions (5.9) and Use in Specific Populations (8.1, 8.3)].

Update immunizations according to current immunization guidelines [see Warnings and Precautions (5.10)].

2.2 Important Administration Instructions

- RINVOQ LQ oral solution is not substitutable with RINVOQ extended-release tablets [see Dosage and Administration (2.4, 2.10)].
- Changes between RINVOQ LQ oral solution and RINVOQ extended-release tablets should be made by the health care provider.
- RINVOQ/RINVOQ LQ should be taken orally with or without food [see Clinical Pharmacology (12.3)].
- RINVOQ tablets should be swallowed whole. RINVOQ tablets should not be split, crushed, or chewed.
- RINVOQ LQ should be administered using the provided press-in bottle adapter and oral dosing syringe [see Instructions for Use].
- RINVOQ LQ is dosed twice daily [see Dosage and Administration (2.4, 2.10)].

2.3 Recommended Dosage in Rheumatoid Arthritis

The recommended dosage of RINVOQ is 15 mg once daily.

2.4 Recommended Dosage in Psoriatic Arthritis

Pediatric Patients 2 to Less Than 18 Years of Age

The recommended dosage is based on body weight (Table 1).

Table 1: RINVOQ/RINVOQ LQ Dosage for Pediatric Patients 2 Years to Less Than 18 Years of Age with Psoriatic Arthritis
Patient Weight | RINVOQ LQ | RINVOQ
10 kg to less than 20 kg | 3 mg (3 mL oral solution) twice daily | Not recommended
20 kg to less than 30 kg | 4 mg (4 mL oral solution) twice daily | Not recommended
30 kg and greater | 6 mg (6 mL oral solution) twice daily | 15 mg (one 15 mg tablet) once daily

RINVOQ LQ oral solution is not substitutable with RINVOQ extended-release tablets. Changes between RINVOQ LQ oral solution and RINVOQ extended-release tablets should be made by the health care provider.

Adults 18 Years of Age and Older

The recommended dosage of RINVOQ is 15 mg once daily.

2.5 Recommended Dosage in Atopic Dermatitis

Pediatric Patients 12 Years of Age and Older Weighing at Least 40 kg and Adults Less Than 65 Years of Age

Initiate treatment with RINVOQ 15 mg once daily. If an adequate response is not achieved, consider increasing the dosage to 30 mg once daily. Discontinue RINVOQ if an adequate response is not achieved with the 30 mg dose. Use the lowest effective dose needed to maintain response.

Adults 65 Years of Age and Older

The recommended dosage of RINVOQ is 15 mg once daily.

2.6 Recommended Dosage in Ulcerative Colitis

Adult Patients: Induction

The recommended induction dosage of RINVOQ is 45 mg once daily for 8 weeks.

Adult Patients: Maintenance

The recommended dosage of RINVOQ for maintenance treatment is 15 mg once daily. A dosage of 30 mg once daily may be considered for patients with refractory, severe or extensive disease. Discontinue RINVOQ if an adequate therapeutic response is not achieved with the 30 mg dosage. Use the lowest effective dosage needed to maintain response.

2.7 Recommended Dosage in Crohn’s Disease

Adult Patients: Induction

The recommended induction dosage of RINVOQ is 45 mg once daily for 12 weeks.

Adult Patients: Maintenance

The recommended dosage of RINVOQ for maintenance treatment is 15 mg once daily. A dosage of 30 mg once daily may be considered for patients with refractory, severe or extensive disease. Discontinue RINVOQ if an adequate therapeutic response is not achieved with the 30 mg dosage. Use the lowest effective dosage needed to maintain response.

2.8 Recommended Dosage in Ankylosing Spondylitis

The recommended dosage of RINVOQ is 15 mg once daily.

2.9 Recommended Dosage in Non-radiographic Axial Spondyloarthritis

The recommended dosage of RINVOQ is 15 mg once daily.

2.10 Recommended Dosage in Polyarticular Juvenile Idiopathic Arthritis

The recommended dosage is based on body weight (Table 2).

Table 2: RINVOQ/RINVOQ LQ Dosage for Patients 2 years and older with pJIA
Patient Weight | RINVOQ LQ | RINVOQ
10 kg to less than 20 kg | 3 mg (3 mL oral solution) twice daily | Not recommended
20 kg to less than 30 kg | 4 mg (4 mL oral solution) twice daily | Not recommended
30 kg and greater | 6 mg (6 mL oral solution) twice daily | 15 mg (one 15 mg tablet) once daily

RINVOQ LQ oral solution is not substitutable with RINVOQ extended-release tablets. Changes between RINVOQ LQ oral solution and RINVOQ extended-release tablets should be made by the health care provider.

2.11 Recommended Dosage in Giant Cell Arteritis

The recommended dosage of RINVOQ is 15 mg once daily in combination with a tapering course of corticosteroids.

RINVOQ 15 mg once daily can be used as monotherapy following discontinuation of corticosteroids.

2.12 Recommended Dosage in Patients with Renal Impairment or Hepatic Impairment

Renal Impairment

Rheumatoid Arthritis, Psoriatic Arthritis, Ankylosing Spondylitis, Non-radiographic Axial Spondyloarthritis, pJIA, and Giant Cell Arteritis:

- No dosage adjustment is needed for patients with mild, moderate, or severe renal impairment.

Atopic Dermatitis:

- For patients with severe renal impairment [estimated glomerular filtration rate (eGFR) 15 to < 30 mL/min/1.73m^2] the recommended dosage of RINVOQ is 15 mg once daily [see Use in Specific Populations (8.6)].
- No dosage adjustment is needed for patients with mild or moderate renal impairment (eGFR ≥ 30 mL/min/1.73m^2).
- RINVOQ is not recommended for use in patients with end stage renal disease (eGFR < 15 mL/min/1.73m^2) [see Use in Specific Populations (8.6)].

Ulcerative Colitis:

- For patients with severe renal impairment (eGFR 15 to < 30 mL/min/1.73m^2), the recommended dosage of RINVOQ is:
  • Induction: 30 mg once daily for 8 weeks
  • Maintenance: 15 mg once daily
- No dosage adjustment is needed for patients with mild or moderate renal impairment (eGFR ≥ 30 mL/min/1.73m^2).
- RINVOQ is not recommended for use in patients with end stage renal disease (eGFR < 15 mL/min/1.73m^2) [see Use in Specific Populations (8.6)].

Crohn’s Disease:

- For patients with severe renal impairment (eGFR 15 to < 30 mL/min/1.73m^2), the recommended dosage of RINVOQ is:
  • Induction: 30 mg once daily for 12 weeks
  • Maintenance: 15 mg once daily
- No dosage adjustment is needed for patients with mild or moderate renal impairment (eGFR ≥ 30 mL/min/1.73m^2).
- RINVOQ is not recommended for use in patients with end stage renal disease (eGFR < 15 mL/min/1.73m^2) [see Use in Specific Populations (8.6)].

Hepatic Impairment

RINVOQ/RINVOQ LQ is not recommended for use in patients with severe hepatic impairment (Child-Pugh C) [see Use in Specific Populations (8.7)].

Rheumatoid Arthritis, Psoriatic Arthritis, Atopic Dermatitis, Ankylosing Spondylitis, Non-radiographic Axial Spondyloarthritis, pJIA, and Giant Cell Arteritis:

No dosage adjustment is needed for patients with mild or moderate hepatic impairment (Child-Pugh A or B).

Ulcerative Colitis:

For patients with mild to moderate hepatic impairment (Child-Pugh A or B) the recommended dosage of RINVOQ is:

- Induction: 30 mg once daily for 8 weeks
- Maintenance: 15 mg once daily

Crohn’s Disease:

For patients with mild to moderate hepatic impairment (Child-Pugh A or B) the recommended dosage of RINVOQ is:

- Induction: 30 mg once daily for 12 weeks
- Maintenance: 15 mg once daily

2.13 Dosage Modifications Due to Drug Interactions

Rheumatoid Arthritis, Psoriatic Arthritis, Ankylosing Spondylitis, Non-radiographic Axial Spondyloarthritis, pJIA, and Giant Cell Arteritis

No dosage adjustment is needed in patients receiving strong CYP3A4 inhibitors [see Drug Interactions (7.1)].

Atopic Dermatitis

The recommended dosage of RINVOQ in patients receiving strong CYP3A4 inhibitors is 15 mg once daily [see Drug Interactions (7.1)].

Ulcerative Colitis

The recommended dosage of RINVOQ in patients with ulcerative colitis receiving strong CYP3A4 inhibitors [see Drug Interactions (7.1)]:

- Induction: 30 mg once daily for 8 weeks
- Maintenance: 15 mg once daily

Crohn’s Disease

The recommended dosage of RINVOQ in patients with Crohn’s disease receiving strong CYP3A4 inhibitors [see Drug Interactions (7.1)]:

- Induction: 30 mg once daily for 12 weeks
- Maintenance: 15 mg once daily

2.14 Dosage Interruption

Infections

If a patient develops a serious infection, including serious opportunistic infection, interrupt RINVOQ/RINVOQ LQ treatment until the infection is controlled [see Warnings and Precautions (5.1)].

Laboratory Abnormalities

Interruption of dosing may be needed for management of laboratory abnormalities as described in Table 3 [see Warnings and Precautions (5.8)].

Table 3: Recommended Dosage Interruptions for Laboratory Abnormalities
Laboratory Measure | Action
Absolute Neutrophil Count (ANC) | Interrupt treatment if ANC is less than 1000 cells/mm^3; treatment may be restarted once ANC returns above this value
Absolute Lymphocyte Count (ALC) | Interrupt treatment if ALC is less than 500 cells/mm^3; treatment may be restarted once ALC returns above this value
Hemoglobin (Hb) | Interrupt treatment if Hb is less than 8 g/dL; treatment may be restarted once Hb returns above this value
Hepatic transaminases | Interrupt treatment if drug-induced liver injury is suspected, until this diagnosis is excluded.

3 DOSAGE FORMS AND STRENGTHS

RINVOQ extended-release tablets:

- 15 mg upadacitinib: purple, biconvex oblong, with dimensions of 14 x 8 mm, and debossed with ‘a15’ on one side.
- 30 mg upadacitinib: red, biconvex oblong, with dimensions of 14 x 8 mm, and debossed with ‘a30’ on one side.
- 45 mg upadacitinib: yellow to mottled yellow, biconvex oblong, with dimensions of 14 x 8 mm, and debossed with ‘a45’ on one side.

RINVOQ LQ oral solution:

- 1 mg/mL upadacitinib; clear, colorless to light yellow solution in bottle of 180 mL.

4 CONTRAINDICATIONS

RINVOQ/RINVOQ LQ is contraindicated in patients with known hypersensitivity to upadacitinib or any of its excipients [see Warnings and Precautions (5.6)].

5 WARNINGS AND PRECAUTIONS

5.1 Serious Infections

Serious and sometimes fatal infections have been reported in patients receiving RINVOQ. The most frequent serious infections reported with RINVOQ included pneumonia and cellulitis [see Adverse Reactions (6.1)]. Among opportunistic infections, tuberculosis, multidermatomal herpes zoster, oral/esophageal candidiasis, and cryptococcosis, were reported with RINVOQ. A higher rate of serious infections was observed with RINVOQ 30 mg compared to RINVOQ 15 mg.

Avoid use of RINVOQ/RINVOQ LQ in patients with an active, serious infection, including localized infections. Consider the risks and benefits of treatment prior to initiating RINVOQ/RINVOQ LQ in patients:

- with chronic or recurrent infection
- who have been exposed to tuberculosis
- with a history of a serious or an opportunistic infection
- who have resided or traveled in areas of endemic tuberculosis or endemic mycoses; or
- with underlying conditions that may predispose them to infection.

Closely monitor patients for the development of signs and symptoms of infection during and after treatment with RINVOQ/RINVOQ LQ. Interrupt RINVOQ/RINVOQ LQ if a patient develops a serious or opportunistic infection.

A patient who develops a new infection during treatment with RINVOQ/RINVOQ LQ should undergo prompt and complete diagnostic testing appropriate for an immunocompromised patient; appropriate antimicrobial therapy should be initiated, the patient should be closely monitored, and RINVOQ/RINVOQ LQ should be interrupted if the patient is not responding to antimicrobial therapy. RINVOQ/RINVOQ LQ may be resumed once the infection is controlled.

Tuberculosis

Evaluate and test patients for latent and active tuberculosis (TB) infection prior to administration of RINVOQ/RINVOQ LQ. Patients with latent TB should be treated with standard antimycobacterial therapy before initiating RINVOQ/RINVOQ LQ. RINVOQ/RINVOQ LQ should not be given to patients with active TB. Consider anti-TB therapy prior to initiation of RINVOQ/RINVOQ LQ in patients with previously untreated latent TB or active TB in whom an adequate course of treatment cannot be confirmed, and for patients with a negative test for latent TB but who have risk factors for TB infection.

Consultation with a physician with expertise in the treatment of TB is recommended to aid in the decision about whether initiating anti-TB therapy is appropriate for an individual patient.

During RINVOQ/RINVOQ LQ use, monitor patients for the development of signs and symptoms of TB, including patients who tested negative for latent TB infection prior to initiating therapy.

Viral Reactivation

Viral reactivation, including cases of herpes virus reactivation (e.g., herpes zoster) and hepatitis B virus reactivation, were reported in clinical trials with RINVOQ [see Adverse Reactions (6.1)]. The risk of herpes zoster appears to be higher in patients treated with RINVOQ in Japan. If a patient develops herpes zoster, consider temporarily interrupting RINVOQ/RINVOQ LQ until the episode resolves.

Screening for viral hepatitis and monitoring for reactivation should be performed in accordance with clinical guidelines before starting and during therapy with RINVOQ/RINVOQ LQ. Patients who were positive for hepatitis C antibody and hepatitis C virus RNA, were excluded from clinical trials. Patients who were positive for hepatitis B surface antigen or hepatitis B virus DNA were excluded from clinical trials. However, cases of hepatitis B reactivation were still reported in patients enrolled in the Phase 3 trials of RINVOQ. If hepatitis B virus DNA is detected while receiving RINVOQ/RINVOQ LQ, a liver specialist should be consulted.

5.2 Mortality

In a large, randomized, postmarketing safety study of another JAK inhibitor in RA patients 50 years of age and older with at least one cardiovascular risk factor, a higher rate of all-cause mortality, including sudden cardiovascular death, was observed in patients treated with the JAK inhibitor compared with TNF blockers.

Consider the benefits and risks for the individual patient prior to initiating or continuing therapy with RINVOQ/RINVOQ LQ.

5.3 Malignancy and Lymphoproliferative Disorders

Malignancies, including lymphomas, were observed in clinical trials of RINVOQ [see Adverse Reactions (6.1)].

In a large, randomized, postmarketing safety study of another JAK inhibitor in RA patients, a higher rate of malignancies (excluding NMSC) was observed in patients treated with the JAK inhibitor compared to those treated with TNF blockers. A higher rate of lymphomas was observed in patients treated with the JAK inhibitor compared to those treated with TNF blockers. A higher rate of lung cancers was observed in current or past smokers treated with the JAK inhibitor compared to those treated with TNF blockers. In this study, current or past smokers had an additional increased risk of overall malignancies.

Consider the benefits and risks for the individual patient prior to initiating or continuing therapy with RINVOQ/RINVOQ LQ, particularly in patients with a known malignancy (other than a successfully treated NMSC), patients who develop a malignancy when on treatment, and patients who are current or past smokers.

Non-Melanoma Skin Cancer

NMSCs have been reported in patients treated with RINVOQ. Periodic skin examination is recommended for patients who are at increased risk for skin cancer.

Exposure to sunlight and UV light should be limited by wearing protective clothing and using a broad-spectrum sunscreen.

5.4 Major Adverse Cardiovascular Events

In a large, randomized, postmarketing safety study of another JAK inhibitor in RA patients 50 years of age and older with at least one cardiovascular risk factor, a higher rate of major adverse cardiovascular events (MACE) defined as cardiovascular death, non-fatal myocardial infarction (MI), and non-fatal stroke was observed with the JAK inhibitor compared to those treated with TNF blockers. Patients who are current or past smokers are at additional increased risk.

Consider the benefits and risks for the individual patient prior to initiating or continuing therapy with RINVOQ/RINVOQ LQ, particularly in patients who are current or past smokers and patients with other cardiovascular risk factors. Patients should be informed about the symptoms of serious cardiovascular events and the steps to take if they occur. Discontinue RINVOQ/RINVOQ LQ in patients that have experienced a myocardial infarction or stroke.

5.5 Thrombosis

Thromboses, including deep venous thrombosis (DVT), pulmonary embolism (PE), and arterial thrombosis, have occurred in patients treated for inflammatory conditions with JAK inhibitors, including RINVOQ. Many of these adverse events were serious and some resulted in death [see Adverse Reactions (6.1)].

In a large, randomized, postmarketing safety study of another JAK inhibitor in RA patients 50 years of age and older with at least one cardiovascular risk factor, higher rates of overall thrombosis, DVT, and PE were observed compared to those treated with TNF blockers.

If symptoms of thrombosis occur, patients should discontinue RINVOQ/RINVOQ LQ and be evaluated promptly and treated appropriately. Avoid RINVOQ/RINVOQ LQ in patients that may be at increased risk of thrombosis.

5.6 Hypersensitivity Reactions

Serious hypersensitivity reactions such as anaphylaxis and angioedema were reported in patients receiving RINVOQ in clinical trials. If a clinically significant hypersensitivity reaction occurs, discontinue RINVOQ/RINVOQ LQ and institute appropriate therapy [see Adverse Reactions (6.1)].

5.7 Gastrointestinal Perforations

Gastrointestinal perforations have been reported in clinical trials with RINVOQ [see Adverse Reactions (6.1)].

Monitor RINVOQ/RINVOQ LQ-treated patients who may be at risk for gastrointestinal perforation (e.g., patients with a history of diverticulitis and those taking concomitant medications including NSAIDs or corticosteroids). Evaluate promptly patients presenting with new onset abdominal pain for early identification of gastrointestinal perforation.

5.8 Laboratory Abnormalities

Neutropenia

Treatment with RINVOQ was associated with an increased incidence of neutropenia (ANC less than 1000 cells/mm^3).

Evaluate neutrophil counts at baseline and thereafter according to routine patient management. Avoid RINVOQ/RINVOQ LQ initiation and interrupt RINVOQ/RINVOQ LQ treatment in patients with a low neutrophil count (i.e., ANC less than 1000 cells/mm^3) [see Dosage and Administration (2.1, 2.14)].

Lymphopenia

ALC less than 500 cells/mm^3 were reported in RINVOQ-treated patients in clinical trials.

Evaluate lymphocyte counts at baseline and thereafter according to routine patient management. Avoid RINVOQ/RINVOQ LQ initiation or interrupt RINVOQ/RINVOQ LQ treatment in patients with a low lymphocyte count (i.e., less than 500 cells/mm^3) [see Dosage and Administration (2.1, 2.14)].

Anemia

Decreases in hemoglobin levels to less than 8 g/dL were reported in RINVOQ-treated patients in clinical trials.

Evaluate hemoglobin at baseline and thereafter according to routine patient management. Avoid RINVOQ/RINVOQ LQ initiation or interrupt RINVOQ/RINVOQ LQ treatment in patients with a low hemoglobin level (i.e., less than 8 g/dL) [see Dosage and Administration (2.1, 2.14)].

Lipids

Treatment with RINVOQ was associated with increases in lipid parameters, including total cholesterol, low-density lipoprotein (LDL) cholesterol, and high-density lipoprotein (HDL) cholesterol [see Adverse Reactions (6.1)]. Elevations in LDL cholesterol decreased to pre-treatment levels in response to statin therapy. The effect of these lipid parameter elevations on cardiovascular morbidity and mortality has not been determined.

Assess lipid parameters approximately 12 weeks after initiation of treatment, and thereafter according to the clinical guidelines for hyperlipidemia. Manage patients according to clinical guidelines for the management of hyperlipidemia.

Liver Enzyme Elevations

Treatment with RINVOQ was associated with increased incidence of liver enzyme elevations compared to treatment with placebo.

Evaluate liver enzymes at baseline and thereafter according to routine patient management. Prompt investigation of the cause of liver enzyme elevation is recommended to identify potential cases of drug-induced liver injury.

If increases in ALT or AST are observed during routine patient management and drug-induced liver injury is suspected, RINVOQ/RINVOQ LQ should be interrupted until this diagnosis is excluded.

5.9 Embryo-Fetal Toxicity

Based on findings in animal studies, RINVOQ/RINVOQ LQ may cause fetal harm when administered to a pregnant woman. Administration of upadacitinib to rats and rabbits during organogenesis caused increases in fetal malformations. Verify the pregnancy status of patients of reproductive potential prior to starting treatment. Advise females of reproductive potential of the potential risk to the fetus and to use effective contraception during treatment with RINVOQ/RINVOQ LQ and for 4 weeks following completion of therapy [see Use in Specific Populations (8.1, 8.3)].

5.10 Vaccinations

Avoid use of live vaccines during or immediately prior to RINVOQ/RINVOQ LQ therapy initiation. Prior to initiating RINVOQ/RINVOQ LQ treatment, it is recommended that patients be brought up to date with all immunizations, including prophylactic varicella zoster or herpes zoster vaccinations, in agreement with current immunization guidelines.

5.11 Medication Residue in Stool

Reports of medication residue in stool or ostomy output have occurred in patients taking RINVOQ. Most reports described anatomic (e.g., ileostomy, colostomy, intestinal resection) or functional gastrointestinal conditions with shortened gastrointestinal transit times. Instruct patients to contact their healthcare provider if medication residue is observed repeatedly. Monitor patients clinically and consider alternative treatment if there is an inadequate therapeutic response.

6 ADVERSE REACTIONS

The following clinically significant adverse reactions are described elsewhere in the labeling:

- Serious Infections [see Warnings and Precautions (5.1)]
- Mortality [see Warnings and Precautions (5.2)]
- Malignancy and Lymphoproliferative Disorders [see Warnings and Precautions (5.3)]
- Major Adverse Cardiovascular Events [see Warnings and Precautions (5.4)]
- Thrombosis [see Warnings and Precautions (5.5)]
- Hypersensitivity Reactions [see Warnings and Precautions (5.6)]
- Gastrointestinal Perforations [see Warnings and Precautions (5.7)]
- Laboratory Abnormalities [see Warnings and Precautions (5.8)]

6.1 Clinical Trials Experience

Because clinical trials are conducted under widely varying conditions, adverse reaction rates observed in the clinical trials of a drug cannot be directly compared to rates in the clinical trials of another drug and may not reflect the rates observed in practice.

Adverse Reactions in Patients with Rheumatoid Arthritis

A total of 3833 adult patients with rheumatoid arthritis were treated with RINVOQ 15 mg or upadacitinib 30 mg tablets once daily in the Phase 3 clinical trials of whom 2806 were exposed for at least one year.

Patients could advance or switch to RINVOQ 15 mg from placebo, or be rescued to RINVOQ from active comparator or placebo from as early as Week 12 depending on the trial design.

A total of 2630 patients received at least 1 dose of RINVOQ 15 mg, of whom 1860 were exposed for at least one year. In trials RA-I, RA-II, RA-III and RA-V, 1213 patients received at least 1 dose of RINVOQ 15 mg, of which 986 patients were exposed for at least one year, and 1203 patients received at least 1 dose of upadacitinib 30 mg, of which 946 were exposed for at least one year.

Table 4: Adverse Reactions Reported in ≥ 1% of Rheumatoid Arthritis Patients Treated with RINVOQ 15 mg in Placebo-controlled Trials
Adverse Reaction | Placebo | RINVOQ 15 mg
 | N = 1042 (%) | N = 1035 (%)
Upper respiratory tract infection (URTI)* | 9.5 | 13.5
Nausea | 2.2 | 3.5
Cough | 1.0 | 2.2
Pyrexia | 0 | 1.2
*URTI includes: acute sinusitis, laryngitis, nasopharyngitis, oropharyngeal pain,
pharyngitis, pharyngotonsillitis, rhinitis, sinusitis, tonsillitis, viral upper respiratory tract
infection

Other adverse reactions reported in less than 1% of patients in the RINVOQ 15 mg group and at a higher rate than in the placebo group through Week 12 included pneumonia, herpes zoster, herpes simplex (includes oral herpes), and oral candidiasis.

Four integrated datasets are presented in the Specific Adverse Reaction section:

Placebo-controlled Trials: Trials RA-III, RA-IV, and RA-V were integrated to represent safety through 12/14 weeks for placebo (n=1042) and RINVOQ 15 mg (n=1035). Trials RA-III and RA-V were integrated to represent safety through 12 weeks for placebo (n=390), RINVOQ 15 mg (n=385), and upadacitinib 30 mg (n=384). Trial RA-IV did not include the 30 mg dose and, therefore, safety data for upadacitinib 30 mg can only be compared with placebo and RINVOQ 15 mg rates from pooling trials RA-III and RA-V.

MTX-controlled Trials: Trials RA-I and RA-II were integrated to represent safety through 12/14 weeks for MTX (n=530), RINVOQ 15 mg (n=534), and upadacitinib 30 mg (n=529).

12-Month Exposure Dataset: Trials RA-I, II, III, and V were integrated to represent the long-term safety of RINVOQ 15 mg (n=1213) and upadacitinib 30 mg (n=1203).

Exposure adjusted incidence rates were adjusted by trial for all the adverse events reported in this section.

Specific Adverse Reactions

Infections

Placebo-controlled Trials: In RA-III, RA-IV, and RA-V, infections were reported in 218 patients (95.7 per 100 patient-years) treated with placebo and 284 patients (127.8 per 100 patient-years) treated with RINVOQ 15 mg. In RA-III and RA-V, infections were reported in 99 patients (136.5 per 100 patient-years) treated with placebo, 118 patients (164.5 per 100 patient-years) treated with RINVOQ 15 mg, and 126 patients (180.3 per 100 patient-years) treated with upadacitinib 30 mg.

MTX-controlled Trials: Infections were reported in 127 patients (119.5 per 100 patient-years) treated with MTX monotherapy, 104 patients (91.8 per 100 patient-years) treated with RINVOQ 15 mg monotherapy, and 128 patients (115.1 per 100 patient-years) treated with upadacitinib 30 mg monotherapy.

12-Month Exposure Dataset: Infections were reported in 615 patients (83.8 per 100 patient-years) treated with RINVOQ 15 mg and 674 patients (99.7 per 100 patient-years) treated with upadacitinib 30 mg.

Serious Infections

Placebo-controlled Trials: In RA-III, RA-IV, and RA-V, serious infections were reported in 6 patients (2.3 per 100 patient-years) treated with placebo, and 12 patients (4.6 per 100 patient-years) treated with RINVOQ 15 mg. In RA-III and RA-V, serious infections were reported in 1 patient (1.2 per 100 patient-years) treated with placebo, 2 patients (2.3 per 100 patient-years) treated with RINVOQ 15 mg, and 7 patients (8.2 per 100 patient-years) treated with upadacitinib 30 mg.

MTX-controlled Trials: Serious infections were reported in 2 patients (1.6 per 100 patient-years) treated with MTX monotherapy, 3 patients (2.4 per 100 patient-years) treated with RINVOQ 15 mg monotherapy, and 8 patients (6.4 per 100 patient-years) treated with upadacitinib 30 mg monotherapy.

12-Month Exposure Dataset: Serious infections were reported in 38 patients (3.5 per 100 patient-years) treated with RINVOQ 15 mg and 59 patients (5.6 per 100 patient-years) treated with upadacitinib 30 mg.

The most frequently reported serious infections were pneumonia and cellulitis.

Tuberculosis

Placebo-controlled Trials and MTX-controlled Trials: In the placebo-controlled period, there were no active cases of tuberculosis reported in the placebo, RINVOQ 15 mg, and upadacitinib 30 mg groups. In the MTX-controlled period, there were no active cases of tuberculosis reported in the MTX monotherapy, RINVOQ 15 mg monotherapy, and upadacitinib 30 mg monotherapy groups.

12-Month Exposure Dataset: Active tuberculosis was reported for 2 patients treated with RINVOQ 15 mg and 1 patient treated with upadacitinib 30 mg. Cases of extra-pulmonary tuberculosis were reported.

Opportunistic Infections (excluding tuberculosis)

Placebo-controlled Trials: In RA-III, RA-IV, and RA-V, opportunistic infections were reported in 3 patients (1.2 per 100 patient-years) treated with placebo, and 5 patients (1.9 per 100 patient-years) treated with RINVOQ 15 mg. In RA-III and RA-V, opportunistic infections were reported in 1 patient (1.2 per 100 patient-years) treated with placebo, 2 patients (2.3 per 100 patient-years) treated with RINVOQ 15 mg, and 6 patients (7.1 per 100 patient-years) treated with upadacitinib 30 mg.

MTX-controlled Trials: Opportunistic infections were reported in 1 patient (0.8 per 100 patient-years) treated with MTX monotherapy, 0 patients treated with RINVOQ 15 mg monotherapy, and 4 patients (3.2 per 100 patient-years) treated with upadacitinib 30 mg monotherapy.

12-Month Exposure Dataset: Opportunistic infections were reported in 7 patients (0.6 per 100 patient-years) treated with RINVOQ 15 mg and 15 patients (1.4 per 100 patient-years) treated with upadacitinib 30 mg.

Malignancies

Placebo-controlled Trials: In RA-III, RA-IV, and RA-V, malignancies excluding NMSC were reported in 1 patient (0.4 per 100 patient-years) treated with placebo, and 1 patient (0.4 per 100 patient-years) treated with RINVOQ 15 mg. In RA-III and RA-V, malignancies excluding NMSC were reported in 0 patients treated with placebo, 1 patient (1.1 per 100 patient-years) treated with RINVOQ 15 mg, and 3 patients (3.5 per 100 patient-years) treated with upadacitinib 30 mg.

MTX-controlled Trials: Malignancies excluding NMSC were reported in 1 patient (0.8 per 100 patient-years) treated with MTX monotherapy, 3 patients (2.4 per 100 patient-years) treated with RINVOQ 15 mg monotherapy, and 0 patients treated with upadacitinib 30 mg monotherapy.

12-Month Exposure Dataset: Malignancies excluding NMSC were reported in 13 patients (1.2 per 100 patient-years) treated with RINVOQ 15 mg and 14 patients (1.3 per 100 patient-years) treated with upadacitinib 30 mg.

Gastrointestinal Perforations

Placebo-controlled Trials: There were no gastrointestinal perforations (based on medical review) reported in patients treated with placebo, RINVOQ 15 mg, and upadacitinib 30 mg.

MTX-controlled Trials: There were no cases of gastrointestinal perforations reported in the MTX and RINVOQ 15 mg group through 12/14 weeks. Two cases of gastrointestinal perforations were observed in the upadacitinib 30 mg group.

12-Month Exposure Dataset: Gastrointestinal perforations were reported in 1 patient treated with RINVOQ 15 mg and 4 patients treated with upadacitinib 30 mg.

Thrombosis

Placebo-controlled Trials: In RA-IV, venous thrombosis (pulmonary embolism or deep vein thrombosis) was observed in 1 patient treated with placebo and 1 patient treated with RINVOQ 15 mg. In RA-V, venous thrombosis was observed in 1 patient treated with RINVOQ 15 mg. There were no observed cases of venous thrombosis reported in RA-III. No cases of arterial thrombosis were observed through 12/14 weeks.

MTX-controlled Trials: In RA-II, venous thrombosis was observed in 0 patients treated with MTX monotherapy, 1 patient treated with RINVOQ 15 mg monotherapy and 0 patients treated with upadacitinib 30 mg monotherapy through Week 14. In RA-II, no cases of arterial thrombosis were observed through 12/14 weeks. In RA-I, venous thrombosis was observed in 1 patient treated with MTX, 0 patients treated with RINVOQ 15 mg and 1 patient treated with upadacitinib 30 mg through Week 24. In RA-I, arterial thrombosis was observed in 1 patient treated with upadacitinib 30 mg through Week 24.

12-Month Exposure Dataset: Venous thrombosis events were reported in 5 patients (0.5 per 100 patient-years) treated with RINVOQ 15 mg and 4 patients (0.4 per 100 patient-years) treated with upadacitinib 30 mg. Arterial thrombosis events were reported in 0 patients treated with RINVOQ 15 mg and 2 patients (0.2 per 100 patient-years) treated with upadacitinib 30 mg.

Laboratory Abnormalities

Hepatic Transaminase Elevations

In placebo-controlled trials (RA-III, RA-IV, and RA-V) with background DMARDs, for up to 12/14 weeks, alanine transaminase (ALT) and aspartate transaminase (AST) elevations ≥ 3 x upper limit of normal (ULN) in at least one measurement were observed in 2.1% and 1.5% of patients treated with RINVOQ 15 mg, and in 1.5% and 0.7% of patients treated with placebo, respectively. In RA-III and RA-V, ALT and AST elevations ≥ 3 x ULN in at least one measurement were observed in 0.8% and 1.0% of patients treated with RINVOQ 15 mg, 1.0% and 0% of patients treated with upadacitinib 30 mg and in 1.3% and 1.0% of patients treated with placebo, respectively.

In MTX-controlled trials, for up to 12/14 weeks, ALT and AST elevations ≥ 3 x ULN in at least one measurement were observed in 0.8% and 0.4% of patients treated with RINVOQ 15 mg, 1.7% and 1.3% of patients treated with upadacitinib 30 mg and in 1.9% and 0.9% of patients treated with MTX, respectively.

Lipid Elevations

Upadacitinib treatment was associated with dose-related increases in total cholesterol, triglycerides and LDL cholesterol. Upadacitinib was also associated with increases in HDL cholesterol. Elevations in LDL and HDL cholesterol peaked by Week 8 and remained stable thereafter. In controlled trials, for up to 12/14 weeks, changes from baseline in lipid parameters in patients treated with RINVOQ 15 mg and upadacitinib 30 mg, respectively, are summarized below:

- Mean LDL cholesterol increased by 14.81 mg/dL and 17.17 mg/dL.
- Mean HDL cholesterol increased by 8.16 mg/dL and 9.01 mg/dL.
- The mean LDL/HDL ratio remained stable.
- Mean triglycerides increased by 13.55 mg/dL and 14.44 mg/dL.

Creatine Phosphokinase Elevations

In placebo-controlled trials (RA-III, RA-IV, and RA-V) with background DMARDs, for up to 12/14 weeks, dose-related increases in creatine phosphokinase (CPK) values were observed. CPK elevations > 5 x ULN were reported in 1.0%, and 0.3% of patients over 12/14 weeks in the RINVOQ 15 mg and placebo groups, respectively. Most elevations >5 x ULN were transient and did not require treatment discontinuation. In RA-III and RA-V, CPK elevations > 5 x ULN were observed in 0.3% of patients treated with placebo, 1.6% of patients treated with RINVOQ 15 mg, and none in patients treated with upadacitinib 30 mg.

Neutropenia

In placebo-controlled trials (RA-III, RA-IV, and RA-V) with background DMARDs, for up to 12/14 weeks, dose-related decreases in neutrophil counts, below 1000 cells/mm^3 in at least one measurement occurred in 1.1% and <0.1% of patients in the RINVOQ 15 mg and placebo groups, respectively. In RA-III and RA-V, decreases in neutrophil counts below 1000 cells/mm^3 in at least one measurement occurred in 0.3% of patients treated with placebo, 1.3% of patients treated with RINVOQ 15 mg, and 2.4% of patients treated with upadacitinib 30 mg. In clinical trials, treatment was interrupted in response to ANC less than 1000 cells/mm^3.

Lymphopenia

In placebo-controlled trials (RA-III, RA-IV, and RA-V) with background DMARDs, for up to 12/14 weeks, dose-related decreases in lymphocyte counts below 500 cells/mm^3 in at least one measurement occurred in 0.9% and 0.7% of patients in the RINVOQ 15 mg and placebo groups, respectively. In RA-III and RA-V, decreases in lymphocyte counts below 500 cells/mm^3 in at least one measurement occurred in 0.5% of patients treated with placebo, 0.5% of patients treated with RINVOQ 15 mg, and 2.4% of patients treated with upadacitinib 30 mg.

Anemia

In placebo-controlled trials (RA-III, RA-IV, and RA-V) with background DMARDs, for up to 12/14 weeks, hemoglobin decreases below 8 g/dL in at least one measurement occurred in <0.1% of patients in both the RINVOQ 15 mg and placebo groups. In RA-III and RA-V, hemoglobin decreases below 8 g/dL in at least one measurement were observed in 0.3% of patients treated with placebo, and none in patients treated with RINVOQ 15 mg and upadacitinib 30 mg.

Adverse Reactions in Patients with Psoriatic Arthritis

A total of 1827 adult patients with psoriatic arthritis were treated with RINVOQ 15 mg or upadacitinib 30 mg tablets once daily in clinical trials, representing 1639.2 patient-years of exposure, of whom 722 were exposed to upadacitinib for at least one year. In the two Phase 3 trials, 907 patients received at least 1 dose of RINVOQ 15 mg, of whom 359 were exposed for at least one year.

Two placebo-controlled trials were integrated (640 patients on RINVOQ 15 mg once daily and 635 patients on placebo) to evaluate the safety of RINVOQ 15 mg in comparison to placebo for up to 24 weeks after treatment initiation.

Overall, the safety profile observed in patients with active psoriatic arthritis treated with RINVOQ 15 mg was consistent with the safety profile observed in patients with rheumatoid arthritis. During the 24-week placebo-controlled period, the frequencies of herpes zoster and herpes simplex were ≥1% (1.1% and 1.4%, respectively) with RINVOQ 15 mg and 0.8% and 1.3%, respectively with placebo. A higher incidence of acne and bronchitis was also observed in patients treated with RINVOQ 15 mg (1.3% and 3.9%, respectively) compared to placebo (0.3% and 2.7%, respectively).

Adverse Reactions in Patients with Atopic Dermatitis

Three Phase 3 (AD-1, AD-2, and AD-3) and one Phase 2b (AD-4) randomized, double-blind, placebo-controlled, multicenter trials evaluated the safety of RINVOQ in patients with moderate-to-severe atopic dermatitis. The majority of patients were White (68%) and male (57%). The mean age was 34 years (ranged from 12 to 75 years) and 13% of the patients were 12 to less than 18 years. In these 4 trials, 2612 patients were treated with RINVOQ 15 mg tablets or 30 mg tablets orally once daily, with or without concomitant topical corticosteroids (TCS).

In the Phase 3 clinical trials (AD-1, AD-2, and AD-3), a total of 1239 patients received RINVOQ 15 mg, of whom 791 were exposed for at least one year and 1246 patients received RINVOQ 30 mg, of whom 826 were exposed for at least one year.

Trials AD-1, AD-2, and AD-4 compared the safety of RINVOQ monotherapy to placebo through Week 16. Trial AD-3 compared the safety of RINVOQ + TCS to placebo + TCS through Week 16.

Weeks 0 to 16 (Trials AD-1 to AD-4)

In RINVOQ trials with and without TCS (Trials AD-1, 2, 3 and 4) through Week 16, the proportion of patients who discontinued treatment because of adverse reactions in the RINVOQ 15 mg, 30 mg and placebo groups were 2.3%, 2.9% and 3.8%, respectively. Table 5 summarizes the adverse reactions that occurred at a rate of at least 1% in the RINVOQ 15 mg or 30 mg groups during the first 16 weeks of treatment.

Table 5: Adverse Reactions Reported in ≥ 1% of Patients with Atopic Dermatitis Treated with RINVOQ 15 mg or 30 mg
Adverse Reaction | Placebo | RINVOQ 15 mg | RINVOQ 30 mg
 | N = 902 (%) | N = 899 (%) | N = 906 (%)
Upper respiratory tract infection (URTI)* | 17 | 23 | 25
Acne** | 2 | 10 | 16
Herpes simplex*** | 2 | 4 | 8
Headache | 4 | 6 | 6
Increased blood creatine phosphokinase | 2 | 5 | 6
Cough | 1 | 3 | 3
Hypersensitivity**** | 2 | 2 | 3
Folliculitis | 1 | 2 | 3
Nausea | 1 | 3 | 3
Abdominal pain***** | 1 | 3 | 2
Pyrexia | 1 | 2 | 2
Increased Weight | 1 | 2 | 2
Herpes zoster****** | 1 | 2 | 2
Influenza | <1 | 2 | 2
Fatigue | 1 | 1 | 2
Neutropenia | <1 | 1 | 2
Myalgia | 1 | 1 | 2
Influenza like illness | 1 | 1 | 2
* Includes: laryngitis, laryngitis viral, nasopharyngitis, oropharyngeal pain, pharyngeal abscess, pharyngitis, pharyngitis streptococcal, pharyngotonsillitis, respiratory tract infection, respiratory tract infection viral, rhinitis, rhinolaryngitis, sinusitis, tonsillitis, tonsillitis bacterial, upper respiratory tract infection, viral pharyngitis, viral upper respiratory tract infection
** Includes: acne and dermatitis acneiform
*** Includes: genital herpes, genital herpes simplex, herpes dermatitis, herpes ophthalmic, herpes simplex, nasal herpes, ophthalmic herpes simplex, herpes virus infection, oral herpes
**** Includes anaphylactic reaction, anaphylactic shock, angioedema, dermatitis exfoliative generalized, drug hypersensitivity, eyelid oedema, face oedema, hypersensitivity, periorbital swelling, pharyngeal swelling, swelling face, toxic skin eruption, type I hypersensitivity, urticaria
***** Includes abdominal pain and abdominal pain upper
****** Includes herpes zoster and varicella

Other adverse reactions reported in less than 1% of patients in the RINVOQ 15 mg and/or 30 mg group and at a higher rate than in the placebo group through Week 16 included anemia, oral candidiasis, pneumonia, non-melanoma skin cancer, and the adverse event of retinal detachment.

The safety profile of RINVOQ through Week 52 was generally consistent with the safety profile observed at Week 16.

Overall, the safety profile observed in patients with AD treated with RINVOQ was similar to the safety profile in patients with RA. Other specific adverse reactions that were reported in patients with AD included eczema herpeticum/Kaposi’s varicelliform eruption.

Eczema Herpeticum/Kaposi’s Varicelliform Eruption

Placebo-controlled Period (16 weeks): Eczema herpeticum was reported in 4 patients (1.6 per 100 patient-years) treated with placebo, 6 patients (2.2 per 100 patient-years) treated with RINVOQ 15 mg and 7 patients (2.6 per 100 patient-years) treated with RINVOQ 30 mg.

12-Month Exposure (Weeks 0 to 52): Eczema herpeticum was reported in 18 patients (1.6 per 100 patient-years) treated with RINVOQ 15 mg and 17 patients (1.5 per 100 patient-years) treated with RINVOQ 30 mg.

Adverse Reactions in Patients with Ulcerative Colitis

RINVOQ was studied up to 8 weeks in patients with moderately to severely active ulcerative colitis in two randomized, double-blind, placebo-controlled induction studies (UC-1, UC-2) and a randomized, double-blind, placebo controlled, dose-finding study (UC-4; NCT02819635). Long term safety up to 52-weeks was evaluated in patients who responded to induction therapy in a randomized, double-blind, placebo-controlled maintenance study (UC-3) and a long-term extension study [see Clinical Studies (14.4)].

In the two induction studies (UC-1, UC-2) and a dose finding study (UC-4), 1097 patients were enrolled of whom 719 patients received RINVOQ 45 mg tablets once daily.

In the maintenance study (UC-3), 746 patients were enrolled of whom 250 patients received RINVOQ 15 mg tablets once daily and 251 patients received RINVOQ 30 mg tablets once daily.

Adverse reactions reported in ≥2% of patients in any treatment arm in the induction and maintenance studies are shown in Tables 6 and 7, respectively.

Table 6: Adverse Reactions Reported in ≥2% of Patients with Ulcerative Colitis Treated with RINVOQ 45 mg in Placebo-Controlled Induction Studies (UC-1, UC-2 and UC-4)
Adverse Reaction | Placebo | RINVOQ 45 mg Once Daily
 | N = 378 (%) | N = 719 (%)
Upper respiratory tract infection* | 7 | 9
Acne* | 1 | 6
Increased blood creatine phosphokinase | 1 | 5
Neutropenia* | <1 | 5
Rash* | 1 | 4
Elevated liver enzymes** | 2 | 3
Lymphopenia* | 1 | 3
Folliculitis | 1 | 2
Herpes simplex* | <1 | 2
* Composed of several similar terms
** Elevated liver enzymes composed of elevated ALT, AST, GGT, ALP, liver transaminases, hepatic enzymes, bilirubin, drug-induced liver injury and cholestasis.

Other adverse reactions reported in less than 2% of patients in the RINVOQ 45 mg group and at a higher rate than in the placebo group through Week 8 included herpes zoster and pneumonia.

Table 7: Adverse Reactions Reported in ≥2% of Patients with Ulcerative Colitis Treated with RINVOQ 15 mg or 30 mg in the Placebo-Controlled Maintenance Study (UC-3)^1
Adverse Reaction | Placebo | RINVOQ 15 mg Once Daily | RINVOQ 30 mg Once Daily
 | N = 245 (%) | N = 250 (%) | N = 251 (%)
Upper respiratory tract infection* | 18 | 17 | 20
Increased blood creatine phosphokinase | 2 | 6 | 8
Pyrexia | 3 | 3 | 6
Neutropenia* | 2 | 3 | 6
Elevated liver enzymes** | 1 | 6 | 4
Rash* | 4 | 5 | 5
Herpes zoster | 0 | 5 | 6
Folliculitis | 2 | 2 | 4
Hypercholesterolemia* | 1 | 2 | 4
Influenza | 1 | 3 | 3
Herpes simplex* | 1 | 2 | 3
Lymphopenia* | 2 | 3 | 2
Hyperlipidemia* | 0 | 2 | 2
^1 Patients who were responders to 8 weeks induction therapy with RINVOQ 45 mg once daily
* Composed of several similar terms
** Elevated liver enzymes composed of elevated ALT, AST, GGT, ALP, liver transaminases, hepatic enzymes, bilirubin, drug-induced liver injury, and cholestasis.

The adverse reaction of non-melanoma skin cancer was reported in 1% of patients in the RINVOQ 30 mg group and none of the patients in the RINVOQ 15 mg or placebo group through Week 52.

The safety profile of RINVOQ in the long-term extension study was similar to the safety profile observed in the placebo-controlled induction and maintenance periods.

Overall, the safety profile observed in patients with ulcerative colitis treated with RINVOQ was generally similar to the safety profile in patients with RA and AD.

Specific Adverse Reactions

Serious Infections

Induction Studies: In UC-1, UC-2, and UC-4, serious infections were reported in 5 patients (8.4 per 100 patient-years) treated with placebo and 9 patients (8.4 per 100 patient-years) treated with RINVOQ 45 mg through 8 weeks.

Placebo-controlled Maintenance Study: In UC-3, serious infections were reported in 8 patients (5.9 events per 100 patient-years) treated with placebo, 9 patients (5.0 events per 100 patient-years) treated with RINVOQ 15 mg, and 8 patients (3.7 events per 100 patient-years) treated with RINVOQ 30 mg through 52 weeks.

Laboratory Abnormalities

Hepatic Transaminase Elevations

In studies UC-1, UC-2, and UC-4, elevations of ALT to ≥ 3 x ULN in at least one measurement were observed in 1.5% of patients treated with RINVOQ 45 mg, and 0% of patients treated with placebo for 8 weeks. AST elevations to ≥ 3 x ULN occurred in 1.5% of patients treated with RINVOQ 45 mg, and 0.3% of patients treated with placebo. Elevations of ALT to ≥ 5 x ULN occurred in 0.4% of patients treated with RINVOQ 45 mg and 0% of patients treated with placebo.

In UC-3, elevations of ALT to ≥ 3 x ULN in at least one measurement were observed in 4.4% of patients treated with RINVOQ 30 mg, 2% of patients treated with RINVOQ 15 mg, and 1.2% of patients treated with placebo for 52 weeks. Elevations of AST to ≥ 3 x ULN in at least one measurement were observed in 2% of patients treated with RINVOQ 30 mg, 1.6% of patients treated with RINVOQ 15 mg and 0.4% of patients treated with placebo. Elevations of ALT to ≥ 5 x ULN were observed in 1.2% of patients treated with 30 mg, 0.4% of patients treated with 15 mg, and 0.4% of patients treated with placebo.

Overall, laboratory abnormalities observed in patients with ulcerative colitis treated with RINVOQ were similar to those described in patients with RA.

Adverse Reactions in Patients with Crohn’s Disease

RINVOQ was studied up to 12 weeks in patients with moderately to severely active CD in two randomized, double-blind, placebo-controlled induction studies (CD-1, CD-2). Long term safety up to 52 weeks was evaluated in patients who responded to induction therapy in a randomized, double-blind, placebo-controlled maintenance study (CD-3), with additional data provided from a long-term extension (LTE) period [see Clinical Studies (14.5)].

In the two induction studies (CD-1, CD-2), 1021 patients were enrolled, of whom 674 patients received RINVOQ 45 mg tablets once daily during the placebo-controlled period.

In the maintenance study (CD-3), 673 patients were enrolled, of whom 221 patients received RINVOQ 15 mg tablets once daily and 229 patients received RINVOQ 30 mg tablets once daily during the randomized, placebo-controlled period.

Overall, the safety profile observed in patients with Crohn’s disease treated with RINVOQ was consistent with the known safety profile for RINVOQ in other indications.

Adverse reactions reported in ≥2% of patients treated with RINVOQ and at a higher rate than placebo in the induction and maintenance studies are shown in Tables 8 and 9, respectively.

Table 8: Adverse Reactions Reported in ≥2% of Patients with Crohn’s Disease Treated with RINVOQ 45 mg in Placebo-Controlled Induction Studies (CD-1 and CD-2)
Adverse Reaction | Placebo | RINVOQ 45 mg Once Daily
 | N = 347 (%) | N = 674 (%)
Upper respiratory tract infection* | 8 | 13
Anemia* | 6 | 7
Acne* | 2 | 6
Pyrexia | 3 | 4
Increased blood creatine phosphokinase | 1 | 3
Influenza | 1 | 3
Herpes simplex* | 1 | 3
Leukopenia* | 1 | 2
Neutropenia* | <1 | 2
Herpes zoster | 0 | 2
* Composed of several similar terms

Adverse reactions reported in less than 2% of patients in the RINVOQ 45 mg group and at a higher rate than in the placebo group through Week 12 included folliculitis, hypercholesterolemia, bronchitis, pneumonia, oral candidiasis, and hyperlipidemia.

Table 9: Adverse Reactions Reported in ≥2% of Patients with Crohn’s Disease Treated with RINVOQ 15 mg or 30 mg in the Placebo-Controlled Maintenance Study (CD-3)^1
Adverse Reaction | Placebo | RINVOQ 15 mg Once Daily | RINVOQ 30 mg Once Daily
 | N = 223 (%) | N = 221 (%) | N = 229 (%)
Upper respiratory tract infection* | 11 | 14 | 12
Pyrexia | 2 | 3 | 7
Herpes zoster* | 2 | 3 | 5
Headache* | 1 | 3 | 5
Acne* | 3 | 2 | 5
Gastroenteritis* | 2 | 3 | 3
Fatigue | 2 | 3 | 3
Increased blood creatine phosphokinase | 1 | 2 | 3
Elevated liver enzymes^2 | <1 | 2 | 3
Leukopenia* | <1 | 1 | 2
Neutropenia* | <1 | 1 | 2
Bronchitis* | 0 | 1 | 2
Pneumonia* | 1 | 4 | 1
Cough | 2 | 3 | 1
^1 Patients who were responders to 12 weeks induction therapy with RINVOQ 45 mg once daily.
^2 Elevated liver enzymes includes alanine aminotransferase increased, aspartate aminotransferase increased, blood alkaline phosphatase increased, transaminases increased, blood bilirubin increased.
* Composed of several similar terms

Adverse reactions reported in less than 2% of patients in the RINVOQ 15 mg or 30 mg group and at a higher rate than in the placebo group through Week 52 included hyperlipidemia, oral candidiasis, and hypercholesterolemia.

The safety profile of RINVOQ in the long-term extension study was similar to the safety profile observed in the placebo-controlled induction and maintenance periods.

Specific Adverse Reactions

Serious Infections

Induction Studies: In CD-1 and CD-2, serious infections were reported in 6 patients (8 per 100 patient-years) treated with placebo and 13 patients (9 per 100 patient-years) treated with RINVOQ 45 mg through 12 weeks of the placebo-controlled period.

Maintenance Study/LTE: In the long-term placebo-controlled period, serious infections were reported in 10 patients (7 per 100 patient-years) treated with placebo, 7 patients (4 per 100 patient-years) treated with RINVOQ 15 mg, and 13 patients (6 per 100 patient-years) treated with RINVOQ 30 mg.

Gastrointestinal Perforations

Induction Studies: During the induction studies in all patients treated with RINVOQ 45 mg (N=938), gastrointestinal perforation was reported in 4 patients (2 per 100 patient-years). In the placebo-controlled induction period, in CD-1 and CD-2, gastrointestinal perforation was reported in no patients treated with placebo (N=347) and 1 patient (1 per 100 patient-years) treated with RINVOQ 45 mg (N=674) through 12 weeks.

Maintenance Study/LTE: In the long-term placebo-controlled period, gastrointestinal perforation was reported in 1 patient (1 per 100 patient-years) treated with placebo, 1 patient (<1 per 100 patient-years) treated with RINVOQ 15 mg, and 1 patient (<1 per 100 patient-years) treated with RINVOQ 30 mg.

Patients who received placebo or RINVOQ 15 mg for maintenance therapy and lost response were treated with rescue RINVOQ 30 mg (N=336). Among these patients, gastrointestinal perforation was reported in 3 patients (1 per 100 patient-years) through long-term treatment.

Adverse Reactions in Patients with Ankylosing Spondylitis

A total of 596 patients with ankylosing spondylitis were treated with RINVOQ 15 mg tablets in the two clinical trials representing 577.3 patient-years of exposure, of whom 220 were exposed to RINVOQ 15 mg for at least one year.

Overall, the safety profile observed in patients with active ankylosing spondylitis treated with RINVOQ 15 mg was consistent with the safety profile observed in patients with rheumatoid arthritis and psoriatic arthritis. During the 14-week placebo-controlled period in Trial AS-I, the frequency of headache was 5.4% with RINVOQ 15 mg and 2.1% with placebo. During the 14-week placebo-controlled period in Trial AS-II, the frequency of headache was 3.3% with RINVOQ 15 mg and 1.4% with placebo.

Adverse Reactions in Patients with Non-radiographic Axial Spondyloarthritis

A total of 187 patients with non-radiographic axial spondyloarthritis were treated with RINVOQ 15 mg tablets in the clinical trial representing 116.6 patient-years of exposure, of whom 31 were exposed to RINVOQ 15 mg for at least one year.

Overall, the safety profile observed in patients with active non-radiographic axial spondyloarthritis treated with RINVOQ 15 mg was consistent with the safety profile observed in patients with rheumatoid arthritis, psoriatic arthritis, and ankylosing spondylitis.

Adverse Reactions in Patients with Polyarticular Juvenile Idiopathic Arthritis

A total of 83 pediatric patients with juvenile idiopathic arthritis (JIA) with active polyarthritis were treated with RINVOQ/RINVOQ LQ in the clinical trial, representing 123.7 patient-years of exposure, of whom 48 were exposed to RINVOQ/RINVOQ LQ for at least one year.

Overall, the safety profile observed in pediatric patients with JIA with active polyarthritis treated with RINVOQ/RINVOQ LQ was consistent with the known safety profile of RINVOQ.

Adverse Reactions in Patients with Giant Cell Arteritis

In the Phase 3 study, 209 patients with giant cell arteritis received at least 1 dose of RINVOQ 15 mg, of whom 122 were exposed for at least one year during the 52-week placebo-controlled period. The safety profile observed in patients with giant cell arteritis was generally consistent with the known safety profile for RINVOQ.

Table 10: Adverse Reactions Reported in ≥ 5% of Patients with Giant Cell Arteritis Treated with RINVOQ 15 mg in the Placebo-controlled Study
Adverse Reaction | Placebo | RINVOQ 15 mg
 | N = 112 (%) | N = 209 (%)
Upper respiratory tract infection (URTI)a | 20.5 | 21.5
Headache | 11.6 | 16.3
Fatigue | 5.4 | 9.1
Peripheral edemab | 2.7 | 8.6
Coughc | 3.6 | 7.2
Anemiad | 2.7 | 6.7
Rashe | 2.7 | 5.7
Herpes zosterf | 2.7 | 5.3
Nausea | 3.6 | 5.3
a Includes acute sinusitis, laryngitis, nasopharyngitis, oropharyngeal pain, pharyngitis, viral pharyngitis, pharyngotonsillitis, rhinitis, sinusitis, tonsillitis, viral upper respiratory tract infection, upper respiratory tract infection
b Includes edema and edema peripheral
c Includes cough and productive cough
d Includes anemia, iron deficiency anemia, blood iron decreased, hemoglobin decreased, mean cell volume increased
e Includes rash, rash erythematous, rash macular, rash maculo-papular, rash vesicular
f Includes herpes zoster, herpes zoster oticus, ophthalmic herpes zoster

Specific Adverse Reactions

Opportunistic Infections (excluding tuberculosis and herpes zoster)

In the 52-week placebo-controlled period, opportunistic infections were reported in 1 patient (1.1 per 100 patient-years) treated with placebo and 4 patients (2.3 per 100 patient-years) treated with RINVOQ 15 mg.

Thrombosis

In the 52-week placebo-controlled period, venous thromboembolic events (pulmonary embolism or deep vein thrombosis) were observed in 4 patients (4.3 per 100 patient-years) treated with placebo and 7 patients (3.9 per 100 patient-years) treated with RINVOQ 15 mg. Events of arterial thrombosis were observed in 2 patients (1.1 per 100 patient-years) treated with RINVOQ 15 mg and 0 patients treated with placebo.

7 DRUG INTERACTIONS

7.1 Strong CYP3A4 Inhibitors

Upadacitinib exposure is increased when it is co-administered with a strong CYP3A4 inhibitor (such as ketoconazole, clarithromycin, and grapefruit), which may increase the risk of adverse reactions [see Clinical Pharmacology (12.3)]. Monitor patients with rheumatoid arthritis, psoriatic arthritis, ankylosing spondylitis, non-radiographic axial spondylarthritis, pJIA, or giant cell arteritis closely for adverse reactions when co-administering RINVOQ/RINVOQ LQ with strong CYP3A4 inhibitors. Food or drink containing grapefruit should be avoided during treatment with RINVOQ/RINVOQ LQ.

For patients with atopic dermatitis, coadministration of RINVOQ 30 mg once daily with strong CYP3A4 inhibitors is not recommended.

For patients with ulcerative colitis or Crohn’s disease taking strong CYP3A4 inhibitors, reduce the RINVOQ induction dosage to 30 mg once daily. The recommended maintenance dosage is 15 mg once daily [see Dosage and Administration (2.13)].

7.2 Strong CYP3A4 Inducers

Upadacitinib exposure is decreased when it is co-administered with strong CYP3A4 inducers (such as rifampin), which may lead to reduced therapeutic effect [see Clinical Pharmacology (12.3)]. Coadministration of RINVOQ/RINVOQ LQ with strong CYP3A4 inducers is not recommended.

8 USE IN SPECIFIC POPULATIONS

8.1 Pregnancy

Pregnancy Surveillance Program

There is a pregnancy surveillance program for RINVOQ/RINVOQ LQ that monitors pregnancy outcomes in women exposed to RINVOQ/RINVOQ LQ. If RINVOQ/RINVOQ LQ exposure occurs during pregnancy, healthcare providers or patients should report the pregnancy by calling 1-800-633-9110.

Risk Summary

Available data from the pharmacovigilance safety database and postmarketing case reports on use of RINVOQ in pregnant women are not sufficient to evaluate a drug-associated risk for major birth defects or miscarriage. Based on animal studies, RINVOQ/RINVOQ LQ has the potential to adversely affect a developing fetus. Advise patients of reproductive potential and pregnant patients of the potential risk to the fetus.

In animal embryo-fetal development studies, oral upadacitinib administration to pregnant rats and rabbits at exposures equal to or greater than approximately 1.6 and 15 times the 15 mg tablet dose, 0.8 and 7.6 times the 30 mg tablet dose, and 0.6 and 5.6 times the maximum recommended human dose (MRHD) of 45 mg (on an AUC basis) resulted in dose-related increases in skeletal malformations (rats only), an increased incidence of cardiovascular malformations (rabbits only), increased post-implantation loss (rabbits only), and decreased fetal body weights in both rats and rabbits. No developmental toxicity was observed in pregnant rats and rabbits treated with oral upadacitinib during organogenesis at exposures approximately 0.29 and 2.2 times the 15 mg dose, 0.15 times and 1.1 times the 30 mg dose, and at 0.11 and 0.82 times the MRHD (on an AUC basis). In a pre- and post-natal development study in pregnant female rats, oral upadacitinib administration at exposures approximately 3 times the 15 mg dose, 1.4 times the 30 mg dose, and the same as the MRHD (on an AUC basis) resulted in no maternal or developmental toxicity (see Data).

The background risks of major birth defects and miscarriage for the indicated populations are unknown. All pregnancies have a background risk of birth defect, loss, or other adverse outcomes. In the U.S. general population, the estimated background risk of major birth defects and miscarriages are 2-4% and 15-20%, respectively.

Clinical Considerations

Disease-Associated Maternal and/or Embryo/Fetal Risk

Published data suggest that increased disease activity is associated with the risk of developing adverse pregnancy outcomes in women with rheumatoid arthritis or inflammatory bowel disease. Adverse pregnancy outcomes include preterm delivery (before 37 weeks of gestation), low birth weight (less than 2500 g) infants, and small for gestational age at birth.

Data

Animal Data

In an oral embryo-fetal development study, pregnant rats received upadacitinib at doses of 5, 25, and 75 mg/kg/day during the period of organogenesis from gestation day 6 to 17. Upadacitinib was teratogenic (skeletal malformations that consisted of misshapen humerus and bent scapula) at exposures equal to or greater than approximately 1.7 times the 15 mg tablet dose, 0.9 times the 30 mg tablet dose, and 0.6 times the MRHD (on an AUC basis at maternal oral doses of 5 mg/kg/day and higher). Additional skeletal malformations (bent forelimbs/hindlimbs and rib/vertebral defects) and decreased fetal body weights were observed in the absence of maternal toxicity at an exposure approximately 84 times the 15 mg dose, 43 times the 30 mg dose, and 31 times the MRHD (on an AUC basis at a maternal oral dose of 75 mg/kg/day).

In a second oral embryo-fetal development study, pregnant rats received upadacitinib at doses of 1.5 and 4 mg/kg/day during the period of organogenesis from gestation day 6 to 17. Upadacitinib was teratogenic (skeletal malformations that included bent humerus and scapula) at exposures approximately 1.6 times the 15 mg dose, 0.8 times the 30 mg dose, and 0.6 times the MRHD (on an AUC basis at maternal oral doses of 4 mg/kg/day). No developmental toxicity was observed in rats at an exposure approximately 0.29 times the 15 mg tablet dose, 0.15 times the 30 mg tablet dose, and 0.11 times the MRHD (on an AUC basis at a maternal oral dose of 1.5 mg/kg/day).

In an oral embryo-fetal developmental study, pregnant rabbits received upadacitinib at doses of 2.5, 10, and 25 mg/kg/day during the period of organogenesis from gestation day 7 to 19. Embryolethality, decreased fetal body weights, and cardiovascular malformations were observed in the presence of maternal toxicity at an exposure approximately 15 times the 15 mg tablet dose, 7.6 times the 30 mg tablet dose, and 5.6 times the MRHD (on an AUC basis at a maternal oral dose of 25 mg/kg/day). Embryolethality consisted of increased post-implantation loss that was due to elevated incidences of both total and early resorptions. No developmental toxicity was observed in rabbits at an exposure approximately 2.2 times the 15 mg tablet dose, 1.1 times the 30 mg tablet dose, and 0.82 times the MRHD (on an AUC basis at a maternal oral dose of 10 mg/kg/day).

In an oral pre- and post-natal development study, pregnant female rats received upadacitinib at doses of 2.5, 5, and 10 mg/kg/day from gestation day 6 through lactation day 20. No maternal or developmental toxicity was observed in either mothers or offspring, respectively, at an exposure approximately 3 times the 15 mg tablet dose, 1.4 times the 30 mg tablet dose, and at approximately the same exposure as the MRHD (on an AUC basis at a maternal oral dose of 10 mg/kg/day).

8.2 Lactation

Risk Summary

There are no data on the presence of upadacitinib in human milk, the effects on the breastfed infant, or the effects on milk production. Available pharmacodynamic/toxicological data in animals have shown excretion of upadacitinib in milk (see Data). When a drug is present in animal milk, it is likely that the drug will be present in human milk. Because of the potential for serious adverse reactions in the breastfed infant, advise patients that breastfeeding is not recommended during treatment with RINVOQ/RINVOQ LQ, and for 6 days (approximately 10 half-lives) after the last dose.

Data

A single oral dose of 10 mg/kg radiolabeled upadacitinib was administered to lactating female Sprague-Dawley rats on post-partum days 7-8. Drug exposure was approximately 30-fold greater in milk than in maternal plasma based on AUC0-t values. Approximately 97% of drug-related material in milk was parent drug.

8.3 Females and Males of Reproductive Potential

Pregnancy Testing

Verify the pregnancy status of females of reproductive potential prior to starting treatment with RINVOQ/RINVOQ LQ [see Use in Specific Populations (8.1)].

Contraception

Females

Based on animal studies, upadacitinib may cause embryo-fetal harm when administered to pregnant women [see Use in Specific Populations (8.1)]. Advise female patients of reproductive potential to use effective contraception during treatment with RINVOQ/RINVOQ LQ and for 4 weeks after the final dose.

8.4 Pediatric Use

Ankylosing Spondylitis, Non-radiographic Axial Spondyloarthritis, Ulcerative Colitis, and Crohn’s Disease

The safety and effectiveness of RINVOQ/RINVOQ LQ in pediatric patients with ankylosing spondylitis, non-radiographic axial spondyloarthritis, ulcerative colitis, or Crohn’s disease have not been established.

Polyarticular Juvenile Idiopathic Arthritis and Psoriatic Arthritis

The safety and effectiveness of RINVOQ/RINVOQ LQ in pediatric patients 2 to less than 18 years of age with pJIA and psoriatic arthritis have been established.

The use of RINVOQ/RINVOQ LQ in these age groups is supported by evidence from well-controlled studies of RINVOQ in adults with rheumatoid arthritis and psoriatic arthritis, pharmacokinetic data from adult patients with rheumatoid arthritis and psoriatic arthritis and 51 pediatric patients with JIA with active polyarthritis, and safety data from 83 pediatric patients 2 to < 18 years of age with JIA with active polyarthritis. Upadacitinib plasma exposures in pediatric patients with pJIA and psoriatic arthritis at the recommended dosage are predicted to be comparable to those observed in adults with rheumatoid arthritis and psoriatic arthritis based on population pharmacokinetic modeling and simulation [see Dosage and Administration (2.4, 2.10), Adverse Reactions (6.1), Clinical Pharmacology (12.3) and Clinical Studies (14.8)].

The safety and effectiveness of RINVOQ/RINVOQ LQ in pediatric patients less than 2 years of age with pJIA or psoriatic arthritis have not been established.

Atopic Dermatitis

The safety and effectiveness of RINVOQ in pediatric patients 12 years of age and older weighing at least 40 kg with atopic dermatitis have been established. A total of 344 pediatric patients aged 12 to 17 years with moderate to severe atopic dermatitis were randomized across three trials (AD-1, AD-2 and AD-3) to receive either RINVOQ 15 mg (N=114) or 30 mg (N=114) or matching placebo (N=116) in monotherapy or combination with topical corticosteroids. Efficacy was consistent between the pediatric patients and adults [see Clinical Studies (14.3)]. The adverse reaction profile in the pediatric patients was similar to the adults [see Adverse Reactions (6.1)].

The safety and effectiveness of RINVOQ in pediatric patients less than 12 years of age with atopic dermatitis have not been established.

The safety and effectiveness of RINVOQ LQ in pediatric patients with atopic dermatitis have not been established.

8.5 Geriatric Use

Rheumatoid Arthritis and Psoriatic Arthritis

Of the 4381 patients treated in the five clinical trials, a total of 906 rheumatoid arthritis patients were 65 years of age or older, including 146 patients 75 years and older. Of the 1827 patients treated in the two psoriatic arthritis Phase 3 clinical trials, a total of 274 patients were 65 years of age or older, including 34 patients 75 years and older. No differences in effectiveness were observed between these patients and younger patients; however, there was a higher rate of overall adverse events, including serious infections, in patients 65 years of age and older.

Atopic Dermatitis

Of the 2583 patients treated in the three Phase 3 clinical trials, a total of 120 patients with atopic dermatitis were 65 years of age or older, including 6 patients 75 years of age. No differences in effectiveness were observed between these patients and younger patients; however, there was a higher rate of serious infections and malignancies in those patients 65 years of age or older in the 30 mg dosing group in the long-term trials.

Ulcerative Colitis

Of the 1097 patients treated in the controlled clinical trials, a total of 95 patients with ulcerative colitis were 65 years and older. Clinical studies of RINVOQ did not include sufficient numbers of patients 65 years of age and older with ulcerative colitis to determine whether they respond differently from younger adult patients.

Crohn’s Disease

Of the 1021 patients who were treated in the controlled induction clinical trials, a total of 39 patients with Crohn’s disease were 65 years of age or older, and no patients were 75 years of age or older. Clinical studies of RINVOQ did not include sufficient numbers of patients 65 years of age and older with Crohn’s disease to determine whether they respond differently from younger adult patients.

Ankylosing Spondylitis

Of the 607 patients treated in the controlled clinical trials, a total of 32 patients with ankylosing spondylitis were 65 years and older. Clinical studies of RINVOQ did not include sufficient numbers of patients 65 years of age and older with ankylosing spondylitis to determine whether they respond differently from younger adult patients.

Non-radiographic Axial Spondyloarthritis

Of the 313 patients treated in a phase 3 clinical trial, a total of 9 patients with non-radiographic axial spondyloarthritis were 65 years and older. Clinical studies of RINVOQ did not include sufficient numbers of patients 65 years of age and older with non-radiographic axial spondyloarthritis to determine whether they respond differently from younger adult patients.

8.6 Renal Impairment

For patients with rheumatoid arthritis, psoriatic arthritis, ankylosing spondylitis, non-radiographic axial spondyloarthritis, pJIA, or giant cell arteritis no dosage adjustment is needed in patients with mild (eGFR 60 to < 90 mL/min/1.73 m^2), moderate (eGFR 30 to < 60 mL/min/1.73 m^2), or severe renal impairment (eGFR 15 to < 30 mL/min/1.73 m^2).

For patients with atopic dermatitis, the maximum recommended dosage of RINVOQ is 15 mg once daily for patients with severe renal impairment. No dosage adjustment is needed in patients with mild or moderate renal impairment.

For patients with ulcerative colitis or Crohn’s disease, the recommended dosage of RINVOQ for severe renal impairment is 30 mg once daily for induction and 15 mg once daily for maintenance. No dosage adjustment is needed in patients with mild or moderate renal impairment [see Dosage and Administration (2.12)].

RINVOQ/RINVOQ LQ has not been studied in patients with end stage renal disease (eGFR <15 mL/min/1.73m^2). Use in patients with atopic dermatitis, ulcerative colitis, or Crohn’s disease with end stage renal disease is not recommended [see Clinical Pharmacology (12.3)].

8.7 Hepatic Impairment

The use of RINVOQ/RINVOQ LQ has not been studied in patients with severe hepatic impairment (Child Pugh C), and is therefore not recommended [see Dosage and Administration (2.12) and Clinical Pharmacology (12.3)].

For patients with rheumatoid arthritis, psoriatic arthritis, atopic dermatitis, ankylosing spondylitis, non-radiographic axial spondyloarthritis, pJIA, or giant cell arteritis, no dosage adjustment is needed in patients with mild (Child Pugh A) or moderate (Child Pugh B) hepatic impairment.

For patients with ulcerative colitis or Crohn’s disease, the recommended dosage of RINVOQ for mild to moderate hepatic impairment is 30 mg once daily for induction and 15 mg once daily for maintenance [see Dosage and Administration (2.12)].

11 DESCRIPTION

RINVOQ and RINVOQ LQ are formulated with upadacitinib, a JAK inhibitor.

Upadacitinib has the following chemical name: (3S,4R)-3-Ethyl-4-(3H-imidazo[1,2-a]pyrrolo[2,3-e]pyrazin-8-yl)-N-(2,2,2-trifluoroethyl)pyrrolidine-1-carboxamide hydrate (2:1).

The strength of upadacitinib is based on anhydrous upadacitinib. The solubility of upadacitinib in water is 38 to less than 0.2 mg/mL across a pH range of 2 to 9 at 37 oC.

Upadacitinib has a molecular weight of 389.38 g/mol and a molecular formula of C17H19F3N6O • ½ H2O. The chemical structure of upadacitinib is:

RINVOQ 15 mg extended-release tablets for oral administration are purple, biconvex oblong, with dimensions of 14 x 8 mm, and debossed with ‘a15’ on one side. Each tablet contains the following inactive ingredients: colloidal silicon dioxide, ferrosoferric oxide, hypromellose, iron oxide red, magnesium stearate, mannitol, microcrystalline cellulose, polyvinyl alcohol, polyethylene glycol, talc, tartaric acid and titanium dioxide.

RINVOQ 30 mg extended-release tablets for oral administration are red, biconvex oblong, with dimensions of 14 x 8 mm, and debossed with ‘a30’ on one side. Each tablet contains the following inactive ingredients: colloidal silicon dioxide, hypromellose, iron oxide red, magnesium stearate, mannitol, microcrystalline cellulose, polyvinyl alcohol, polyethylene glycol, talc, tartaric acid and titanium dioxide.

RINVOQ 45 mg extended-release tablets for oral administration are yellow to mottled yellow, biconvex oblong, with dimensions of 14 x 8 mm, and debossed with ‘a45’ on one side. Each tablet contains the following inactive ingredients: colloidal silicon dioxide, hypromellose, iron oxide yellow, iron oxide red, magnesium stearate, mannitol, microcrystalline cellulose, polyvinyl alcohol, polyethylene glycol, talc, tartaric acid and titanium dioxide.

RINVOQ LQ oral solution for oral administration is a 1 mg/mL clear, colorless to light yellow solution. Each 1 mL RINVOQ LQ contains 1 mg of upadacitinib as free base (equivalent to 1.02 mg upadacitinib hemihydrate) and the following inactive ingredients: citric acid anhydrous, purified water, sodium benzoate, sodium citrate dihydrate, and sucralose.

12 CLINICAL PHARMACOLOGY

12.1 Mechanism of Action

Upadacitinib is a Janus kinase (JAK) inhibitor. JAKs are intracellular enzymes which transmit signals arising from cytokine or growth factor-receptor interactions on the cellular membrane to influence cellular processes of hematopoiesis and immune cell function. Within the signaling pathway, JAKs phosphorylate and activate signal transducers and activators of transcription (STATs) which modulate intracellular activity including gene expression. Upadacitinib modulates the signaling pathway at the point of JAKs, preventing the phosphorylation and activation of STATs.

JAK enzymes transmit cytokine signaling through their pairing (e.g., JAK1/JAK2, JAK1/JAK3, JAK1/TYK2, JAK2/JAK2, JAK2/TYK2). In a cell-free isolated enzyme assay, upadacitinib had greater inhibitory potency at JAK1 and JAK2 relative to JAK3 and TYK2. In human leukocyte cellular assays, upadacitinib inhibited cytokine-induced STAT phosphorylation mediated by JAK1 and JAK1/JAK3 more potently than JAK2/JAK2 mediated STAT phosphorylation. The relevance of inhibition of specific JAK enzymes to therapeutic effectiveness is not currently known.

12.2 Pharmacodynamics

Inhibition of IL-6 Induced STAT3 and IL-7 Induced STAT5 Phosphorylation

In healthy volunteers, the administration of upadacitinib (immediate release formulation) resulted in a dose- and concentration-dependent inhibition of IL-6 (JAK1/JAK2)-induced STAT3 and IL-7 (JAK1/JAK3)-induced STAT5 phosphorylation in whole blood. The maximal inhibition was observed 1 hour after dosing which returned to near baseline by the end of dosing interval.

Lymphocytes

In patients with rheumatoid arthritis, treatment with upadacitinib was associated with a small, transient increase in mean ALC from baseline up to Week 36 which gradually returned to, at or near baseline levels with continued treatment.

Immunoglobulins

In patients with rheumatoid arthritis, small decreases from baseline in mean IgG and IgM levels were observed with upadacitinib treatment in the controlled period; however, the mean values at baseline and at all visits were within the normal reference range.

Cardiac Electrophysiology

At 2.5 times the mean exposure of the maximum therapeutic dose, 45 mg once daily dose, there was no clinically relevant effect on the QTc interval.

12.3 Pharmacokinetics

Upadacitinib plasma exposures are proportional to dose over the therapeutic dose range. After a single dose administration of RINVOQ 15 mg, 30 mg, and 45 mg tablets under fasting condition in healthy subjects, mean Cmax was 31.6 ng/mL, 71.8 ng/mL, and 90.7 ng/mL, respectively, and mean AUCinf was 265 ng·h/mL, 543 ng·h/mL, and 752 ng·h/mL, respectively. Steady-state plasma concentrations are achieved within 4 days with minimal accumulation after once daily administration. Following the administration of the recommended pediatric dosage (Table 1, Table 2) in pJIA and psoriatic arthritis patients, the mean steady-state Cmax is predicted to be 47.6 ng/mL and the mean steady-state AUC0-24 is predicted to be 342 ng·h/mL. Upadacitinib pharmacokinetics are comparable between rheumatoid arthritis, psoriatic arthritis, atopic dermatitis, ulcerative colitis, Crohn’s disease, ankylosing spondylitis, non-radiographic axial spondyloarthritis, and giant cell arteritis patients.

RINVOQ tablets and RINVOQ LQ are not bioequivalent; therefore, the 2 dosage forms are not interchangeable on a milligram-per-milligram basis [see Dosage and Administration (2.2)].

Absorption

Following oral administration of RINVOQ extended-release tablets, upadacitinib is absorbed with a median Tmax of 2 to 4 hours. Following oral administration of 6 mg RINVOQ LQ, upadacitinib is absorbed with a median Tmax of 1 hour.

Coadministration of RINVOQ tablets with a high-fat/high-calorie meal had no clinically relevant effect on upadacitinib exposures (increased AUCinf by 29% and Cmax by 39% to 60%). Coadministration of RINVOQ LQ with food is not expected to have a clinically relevant effect on upadacitinib exposure [see Dosage and Administration (2.2)].

Distribution

Upadacitinib is 52% bound to plasma proteins. Upadacitinib partitions similarly between plasma and blood cellular components with a blood to plasma ratio of 1.0.

Elimination

Metabolism

Upadacitinib metabolism is mediated by mainly CYP3A4 with a potential minor contribution from CYP2D6. The pharmacologic activity of upadacitinib is attributed to the parent molecule. In a human radiolabeled study, unchanged upadacitinib accounted for 79% of the total radioactivity in plasma while the main metabolite detected (product of monooxidation followed by glucuronidation) accounted for 13% of the total plasma radioactivity. No active metabolites have been identified for upadacitinib.

Excretion

Following single dose administration of [^14C]-upadacitinib immediate-release solution, upadacitinib was eliminated predominantly as the unchanged parent drug in urine (24%) and feces (38%). Approximately 34% of upadacitinib dose was excreted as metabolites. Upadacitinib mean terminal elimination half-life ranged from 8 to 14 hours.

Specific Populations

Body Weight, Gender, and Race

Body weight, gender, race, and ethnicity did not have a clinically meaningful effect on upadacitinib exposure in adult patient populations.

Pediatric Patients

In pediatric patients with JIA with active polyarthritis, upadacitinib clearance increased with increasing body weight. Age (over the range of 2 to < 18 years old) had no additional effect on upadacitinib pharmacokinetics after accounting for the effect of body weight. Upadacitinib plasma exposures in pediatric patients with pJIA and psoriatic arthritis following the recommended pediatric dosage are predicted to be comparable to those observed in adult patients with rheumatoid arthritis and psoriatic arthritis, respectively.

No meaningful difference in the systemic exposure of upadacitinib was observed in pediatric patients with atopic dermatitis 12 years of age and older weighing at least 40 kg compared to adults.

Geriatric Patients

No clinically meaningful differences in the pharmacokinetics of upadacitinib were observed in geriatric patients (≥ 65 years of age) compared to younger adult patients.

Patients with Renal Impairment

Upadacitinib mean AUCinf after a single dose administration of 15 mg upadacitinib tablets was 18%, 33%, and 44% higher in patients with mild (eGFR 60 to < 90 mL/min/1.73 m^2), moderate (eGFR 30 to < 60 mL/min/1.73 m^2), and severe renal impairment (eGFR 15 to < 30 mL/min/1.73 m^2), respectively, compared to subjects with normal renal function (eGFR ≥ 90 mL/min/1.73 m^2). Upadacitinib mean Cmax was similar among subjects with normal and impaired renal function. In patients receiving RINVOQ/RINVOQ LQ, mild and moderate renal impairment is not expected to have a clinically relevant effect on upadacitinib exposure [see Dosage and Administration (2.12) and Use in Specific Populations (8.6)].

Patients with Hepatic Impairment

Upadacitinib mean AUCinf after a single dose administration of 15 mg upadacitinib tablets was 28% and 24% higher in patients with mild (Child-Pugh A) and moderate (Child-Pugh B) hepatic impairment, respectively, compared to subjects with normal liver function. Upadacitinib mean Cmax was unchanged in patients with mild hepatic impairment and 43% higher in patients with moderate hepatic impairment compared to subjects with normal liver function. Upadacitinib was not studied in patients with severe hepatic impairment (Child-Pugh C) [see Dosage and Administration (2.12) and Use in Specific Populations (8.7)].

Drug Interaction Studies

Potential for Other Drugs to Influence the Pharmacokinetics of Upadacitinib

Upadacitinib is metabolized in vitro by CYP3A4 with a minor contribution from CYP2D6. The effect of co-administered drugs on upadacitinib plasma exposures is provided in Table 11 [see Drug Interactions (7)].

Table 11: Change in Pharmacokinetics of Upadacitinib in the Presence of Co-administered Drugs
Co- administered Drug | Regimen of Co- administered Drug | Ratio (90% CI) a
 |  | Cmax | AUC
Methotrexate | 10 to 25 mg/week | 0.97 (0.86-1.09) | 0.99 (0.93- 1.06)
Strong CYP3A4 inhibitor: Ketoconazole | 400 mg once daily x 6 days | 1.70 (1.55-1.89) | 1.75 (1.62-1.88)
Strong CYP3A4 inducer: Rifampin | 600 mg once daily x 9 days | 0.49 (0.44-0.55) | 0.39 (0.37-0.42)
OATP1B inhibitor: Rifampin | 600 mg single dose | 1.14 (1.02-1.28) | 1.07 (1.01-1.14)
CI: Confidence interval
a Ratios for Cmax and AUC compare co-administration of the medication with upadacitinib vs.
administration of upadacitinib alone.

pH modifying medications (e.g., antacids or proton pump inhibitors) are not expected to affect upadacitinib plasma exposures based on in vitro assessments and population pharmacokinetic analyses. CYP2D6 metabolic phenotype had no effect on upadacitinib pharmacokinetics (based on population pharmacokinetic analyses), indicating that inhibitors of CYP2D6 have no clinically relevant effect on upadacitinib exposures.

Potential for Upadacitinib to Influence the Pharmacokinetics of Other Drugs

In vitro studies indicate that upadacitinib does not inhibit the activity of cytochrome P450 (CYP) enzymes (CYP1A2, CYP2B6, CYP2C8, CYP2C9, CYP2C19, CYP2D6, and CYP3A4) at clinically relevant concentrations. In vitro studies indicate that upadacitinib induces CYP3A4 but does not induce CYP2B6 or CYP1A2 at clinically relevant concentrations. In vitro studies indicate that upadacitinib does not inhibit the transporters P-gp, BCRP, OATP1B1, OATP1B3, OCT1, OCT2, OAT1, OAT3, MATE1, and MATE2K at clinically relevant concentrations.

Clinical studies indicate that upadacitinib has no clinically relevant effects on the pharmacokinetics of co-administered drugs. Following upadacitinib 30 mg and 45 mg tablets once daily, the effects on each CYP enzymes (CYP1A2, CYP3A, CYP2C9, and CYP2C19) were similar between two doses except for the effect on CYP2D6. Following upadacitinib 30 mg and 45 mg tablets once daily, a weak induction of CYP3A4 was observed. A weak inhibition of CYP2D6 was observed at upadacitinib 45 mg but not at 30 mg. Summary of results from clinical studies which evaluated the effect of upadacitinib on other drugs is provided in Table 12.

Table 12: Change in Pharmacokinetics of Co-administered Drugs or In Vivo Markers of CYP Activity in the Presence of Upadacitinib

Co-administered Drug or CYP Activity Marker | Multiple-Dose Regimen of Upadacitinib | Ratio (90% CI) a
 |  | Cmax | AUC
Methotrexate | 6 mg to 24 mg BIDb | 1.03 (0.86-1.23) | 1.14 (0.91-1.43)
Sensitive CYP1A2 Substrate: Caffeine | 45 mg QDc | 1.05 (0.97-1.14) | 1.04 (0.95-1.13)
Sensitive CYP3A Substrate: Midazolam | 30 mg QDc | 0.74 (0.68-0.80) | 0.74 (0.68-0.80)
Sensitive CYP3A Substrate: Midazolam | 45 mg QDc | 0.75 (0.69 -0.83) | 0.76 (0.69 -0.83)
Sensitive CYP2D6 Substrate: Dextromethorphan | 30 mg QDc | 1.09 (0.98-1.21) | 1.07 (0.95-1.22)
Sensitive CYP2D6 Substrate: Dextromethorphan | 45 mg QDc | 1.30 (1.13-1.50) | 1.35 (1.18-1.54)
Sensitive CYP2C9 Substrate: S-Warfarin | 45 mg QDc | 1.18 (1.05-1.33) | 1.12 (1.05-1.20)
Sensitive CYP2C19 Marker: 5-OH Omeprazole to Omeprazole metabolic ratio | 45 mg QDc | -- | 0.96 (0.90-1.02)
CYP2B6 Substrate: Bupropion | 30 mg QDc | 0.87 (0.79-0.96) | 0.92 (0.87-0.98)
Rosuvastatin | 30 mg QDc | 0.77 (0.63-0.94) | 0.67 (0.56-0.82)
Atorvastatin | 30 mg QDc | 0.88 (0.79-0.97) | 0.77 (0.70-0.85)
Ethinylestradiol | 30 mg QDc | 0.96 (0.89-1.02) | 1.11 (1.04-1.19)
Levonorgestrel | 30 mg QDc | 0.96 (0.87-1.06) | 0.96 (0.85-1.07)
CYP: cytochrome P450; CI: Confidence interval; BID: twice daily; QD: once daily
a Ratios for Cmax and AUC compare co-administration of the medication with upadacitinib vs. administration of medication alone.
b Immediate-release formulation
c Extended-release tablet formulation

13 NONCLINICAL TOXICOLOGY

13.1 Carcinogenesis, Mutagenesis, Impairment of Fertility

Carcinogenesis

The carcinogenic potential of upadacitinib was evaluated in Sprague-Dawley rats and Tg.rasH2 mice. No evidence of tumorigenicity was observed in male or female rats that received upadacitinib for up to 101 weeks at oral doses up to 15 or 20 mg/kg/day, respectively (approximately 4 and 10 times the 15 mg tablet dose, 2 and 5 times the 30 mg tablet dose, and 1.6 and 4 times the maximum recommended human dose (MRHD) of 45 mg on an AUC basis, respectively). No evidence of tumorigenicity was observed in male or female Tg.rasH2 mice that received upadacitinib for 26 weeks at oral doses up to 20 mg/kg/day.

Mutagenesis

Upadacitinib tested negative in the following genotoxicity assays: the in vitro bacterial mutagenicity assay (Ames assay), in vitro chromosome aberration assay in human peripheral blood lymphocytes, and in vivo rat bone marrow micronucleus assay.

Impairment of Fertility

Upadacitinib had no effect on fertility in male or female rats at oral doses up to 50 mg/kg/day in males and 75 mg/kg/day in females (approximately 42 and 84 times the 15 mg dose, 22 and 43 times the 30 mg dose, and 16 and 31 times the MRHD, respectively, on an AUC basis). However, maintenance of pregnancy was adversely affected at oral doses of 25 mg/kg/day and 75 mg/kg/day based upon dose-related findings of increased post-implantation losses (increased resorptions) and decreased numbers of mean viable embryos per litter (approximately 22 and 84 times the 15 mg tablet dose, 11 and 43 times the 30 mg tablet dose, and 8 and 31 times the MRHD on an AUC basis, respectively). The number of viable embryos was unaffected in female rats that received upadacitinib at an oral dose of 5 mg/kg/day and were mated to males that received the same dose (approximately 2 times the 15 mg dose, 0.9 times the 30 mg dose, and at 0.6 times the MRHD on an AUC basis).

14 CLINICAL STUDIES

14.1 Rheumatoid Arthritis

The efficacy and safety of RINVOQ 15 mg once daily were assessed in five Phase 3 randomized, double-blind, multicenter trials in patients with moderately to severely active rheumatoid arthritis and fulfilling the ACR/EULAR 2010 classification criteria. Patients 18 years of age and older were eligible to participate. The presence of at least 6 tender and 6 swollen joints and evidence of systemic inflammation based on elevation of hsCRP was required at baseline. Although other doses have been studied, the recommended dosage of RINVOQ is 15 mg once daily.

Trial RA-I (NCT02706873) was a 24-week monotherapy trial in 947 patients with moderately to severely active rheumatoid arthritis who were naïve to methotrexate (MTX). Patients received RINVOQ 15 mg or upadacitinib 30 mg orally once daily or MTX as monotherapy. At Week 26, non-responding patients on upadacitinib could be rescued with the addition of MTX, while patients on MTX could be rescued with the addition of blinded RINVOQ 15 mg or upadacitinib 30 mg once daily. The primary endpoint was the proportion of patients who achieved an ACR50 response at Week 12. Key secondary endpoints included disease activity score (DAS28-CRP) ≤3.2 at Week 12, DAS28-CRP <2.6 at Week 24, change from baseline in HAQ-DI at Week 12, and change from baseline in van der Heijde-modified total Sharp Score (mTSS) at Week 24.

Trial RA-II (NCT02706951) was a 14-week monotherapy trial in 648 patients with moderately to severely active rheumatoid arthritis who had an inadequate response to MTX. Patients received RINVOQ 15 mg or upadacitinib 30 mg once daily monotherapy or continued their stable dose of MTX monotherapy. At Week 14, patients who were randomized to MTX were advanced to RINVOQ 15 mg or upadacitinib 30 mg once daily monotherapy in a blinded manner based on pre-determined assignment at baseline. The primary endpoint was the proportion of patients who achieved an ACR20 response at Week 14. Key secondary endpoints included DAS28-CRP ≤3.2, DAS28-CRP <2.6, and change from baseline in HAQ-DI at Week 14.

Trial RA-III (NCT02675426) was a 12-week trial in 661 patients with moderately to severely active rheumatoid arthritis who had an inadequate response to conventional disease modifying anti-rheumatic drugs (cDMARDs). Patients received RINVOQ 15 mg or upadacitinib 30 mg once daily or placebo added to background cDMARD therapy. At Week 12, patients who were randomized to placebo were advanced to RINVOQ 15 mg or upadacitinib 30 mg once daily in a blinded manner based on pre-determined assignment at baseline. The primary endpoint was the proportion of patients who achieved an ACR20 response at Week 12. Key secondary endpoints included DAS28-CRP ≤3.2, DAS28-CRP<2.6, and change from baseline in HAQ-DI at Week 12.

Trial RA-IV (NCT02629159) was a 48-week trial in 1629 patients with moderately to severely active rheumatoid arthritis who had an inadequate response to MTX. Patients received RINVOQ 15 mg once daily, active comparator, or placebo added to background MTX. From Week 14, non-responding patients on RINVOQ 15 mg could be rescued to active comparator in a blinded manner, and non-responding patients on active comparator or placebo could be rescued to RINVOQ 15 mg in a blinded manner. At Week 26, all patients randomized to placebo were switched to RINVOQ 15 mg once daily in a blinded manner. The primary endpoint was the proportion of patients who achieved an ACR20 response at Week 12 versus placebo. Key secondary endpoints versus placebo included DAS28-CRP ≤3.2, DAS28-CRP <2.6, change from baseline in HAQ-DI at Week 12, and change from baseline in mTSS at Week 26.

Trial RA-V (NCT02706847) was a 12-week trial in 499 patients with moderately to severely active rheumatoid arthritis who had an inadequate response or intolerance to biologic DMARDs. Patients received RINVOQ 15 mg or upadacitinib 30 mg once daily or placebo added to background cDMARD therapy. At Week 12, patients who were randomized to placebo were advanced to RINVOQ 15 mg or upadacitinib 30 mg once daily in a blinded manner based on pre-determined assignment at baseline. The primary endpoint was the proportion of patients who achieved an ACR20 response at Week 12. Key secondary endpoints included DAS28-CRP ≤3.2 and change from baseline in HAQ-DI at Week 12.

Clinical Response

The percentages of RINVOQ-treated patients achieving ACR20, ACR50, and ACR70 responses, and DAS28(CRP) < 2.6 in all trials are shown in Table 13.

Patients treated with RINVOQ 15 mg, alone or in combination with cDMARDs, achieved higher ACR response rates compared to MTX monotherapy or placebo, respectively, at the primary efficacy timepoint (Table 13).

In Trial IV, the percent of patients achieving ACR20 response by visit is shown in Figure 1.

In Trials RA-III and RA-V, higher ACR20 response rates were observed at 1 week with RINVOQ 15 mg versus placebo.

Treatment with RINVOQ 15 mg, alone or in combination with cDMARDs, resulted in greater improvements in the ACR components compared to MTX or placebo at the primary efficacy timepoint (Table 14).

Table 13: Clinical Response in RA Patients in Trials RA-I, RA-II, RA-III, RA-IV and RA V
 | Trial RA-I MTX-Naïve |  | Trial RA-II MTX-IR |  | Trial RA-III cDMARD-IR |  | Trial RA-IV MTX-IR |  | Trial RA-V bDMARD-IR
 | Monotherapy |  | Monotherapy |  | Background cDMARDs |  | Background MTX |  | Background cDMARDs
 | MTX | RINVOQ 15 mg % Δ (95% CI) | MTX | RINVOQ 15 mg % Δ (95% CI) | PBO | RINVOQ 15 mg % Δ (95% CI) | PBO | RINVOQ 15 mg % Δ (95% CI) | PBO | RINVOQ 15 mg % Δ (95% CI)
N | 314 | 317 | 216 | 217 | 221 | 221 | 651 | 651 | 169 | 164
Week
ACR20
12a/14b | 54 | 76 22 (14, 29) | 41 | 68 26 (17, 36) | 36 | 64 28 (19, 37) | 36 | 71 34 (29, 39) | 28 | 65 36 (26, 46)
24c/26d | 59 | 79 20 (13, 27) |  |  |  |  | 36 | 67 32 (27, 37)
ACR50
12a/14b | 28 | 52 24 (16, 31) | 15 | 42 27 (18, 35) | 15 | 38 23 (15, 31) | 15 | 45 30 (26, 35) | 12 | 34 22 (14, 31)
24c/26d | 33 | 60 27 (19, 34) |  |  |  |  | 21 | 54 33 (28, 38)
ACR70
12a/14b | 14 | 32 18 (12, 25) | 3 | 23 20 (14, 26) | 6 | 21 15 (9, 21) | 5 | 25 20 (16, 24) | 7 | 12 5 (-1, 11)
24c/26d | 18 | 44 26 (19, 33) |  |  |  |  | 10 | 35 25 (21, 29)
DAS28-CRP <2.6
12a/14b | 14 | 36 22 (15, 28) | 8 | 28 20 (13, 27) | 10 | 31 21 (14, 28) | 6 | 29 23 (19, 27) | 9 | 29 19 (11, 27)
24c/26d | 18 | 48 30 (23, 37) |  |  |  |  | 9 | 41 32 (27, 36)
Abbreviations: ACR20 (or 50 or 70) = American College of Rheumatology ≥20% (or ≥50% or ≥70%) improvement; bDMARD = biologic disease-modifying anti-rheumatic drug; CRP = c-reactive protein; DAS28 = Disease Activity Score 28 joints; cDMARDs = conventional disease-modifying anti-rheumatic drugs; MTX = methotrexate; PBO = placebo; IR = inadequate responder
Patients who discontinued randomized treatment, or had cross-over between randomized treatments, or were missing data at week of evaluation were imputed as non-responders in the analyses.
a Trial RA-I, Trial RA-III, Trial RA-IV, Trial RA-V
b Trial RA-II
c Trial RA-I
d Trial RA-IV

Table 14: Components of ACR Response at Primary Efficacy Timepointa
 | Trial RA-I MTX-Naïve |  | Trial RA-IIb MTX-IR |  | Trial RA-III cDMARD-IR |  | Trial RA-IV MTX-IR |  | Trial RA-V bDMARD-IR
 | Monotherapy |  | Monotherapy |  | Background cDMARDs |  | Background MTX |  | Background cDMARDs
 | MTX | RINVOQ 15 mg | MTX | RINVOQ 15 mg | PBO | RINVOQ 15 mg | PBO | RINVOQ 15 mg | PBO | RINVOQ 15 mg
N | 314 | 317 | 216 | 217 | 221 | 221 | 651 | 651 | 169 | 164
Number of tender joints (0-68)
Baseline | 26 (16) | 25 (14) | 25 (16) | 24 (15) | 25 (15) | 25 (14) | 26 (14) | 26 (15) | 28 (15) | 28 (16)
Week 12/14 | 13 (15) | 9 (12) | 15 (16) | 10 (13) | 16 (17) | 12 (14) | 16 (15) | 10 (13) | 18 (17) | 11 (14)
Number of swollen joints (0-66)
Baseline | 17 (11) | 17 (10) | 17 (12) | 16 (11) | 15 (9) | 16 (10) | 16 (9) | 17 (10) | 16 (10) | 17 (11)
Week 12/14 | 6 (8) | 5 (7) | 9 (11) | 6 (9) | 9 (10) | 7 (10) | 9 (9) | 5 (7) | 9 (10) | 6 (8)
Painc
Baseline | 66 (21) | 68 (21) | 63 (21) | 62 (23) | 62 (21) | 64 (19) | 65 (21) | 66 (21) | 69 (21) | 68 (20)
Week 12/14 | 41 (25) | 31 (25) | 49 (25) | 36 (27) | 51 (26) | 33 (24) | 49 (25) | 33 (24) | 55 (28) | 41 (28)
Patient global assessmentc
Baseline | 66 (21) | 67 (22) | 60 (22) | 62 (22) | 60 (20) | 63 (22) | 64 (21) | 64 (22) | 66 (23) | 67 (20)
Week 12/14 | 42 (25) | 31 (24) | 48 (26) | 37 (27) | 50 (26) | 32 (24) | 48 (24) | 33 (24) | 54 (28) | 40 (26)
Disability Index (HAQ-DI) d
Baseline | 1.60 (0.67) | 1.60 (0.67) | 1.47 (0.66) | 1.47 (0.66) | 1.42 (0.63) | 1.48 (0.61) | 1.61 (0.61) | 1.63 (0.64) | 1.56 (0.60) | 1.67 (0.64)
Week 12/14 | 1.08 (0.72) | 0.76 (0.69) | 1.19 (0.69) | 0.86 (0.67) | 1.13 (0.70) | 0.85 (0.66) | 1.28 (0.67) | 0.98 (0.68) | 1.33 (0.66) | 1.24 (0.77)
Physician global assessmentc
Baseline | 69 (16) | 67 (17) | 62 (17) | 66 (18) | 64 (18) | 64 (16) | 66 (18) | 66 (17) | 67 (17) | 69 (17)
Week 12/14 | 32 (22) | 22 (19) | 37 (24) | 26 (21) | 41 (24) | 26 (21) | 41 (25) | 27 (21) | 39 (25) | 29 (22)
CRP (mg/L)
Baseline | 21.2 (22.1) | 23.0 (27.4) | 14.5 (17.3) | 14.0 (16.5) | 12.6 (14.0) | 16.6 (19.2) | 18.0 (21.5) | 17.9 (22.5) | 16.3 (21.1) | 16.3 (18.6)
Week 12/14 | 10.9 (14.9) | 4.2 (8.8) | 12.8 (21.4) | 3.7 (7.8) | 13.1 (15.5) | 4.6 (9.6) | 16.2 (19.8) | 5.5 (10.9) | 13.9 (17.3) | 5.0 (14.0)
Abbreviations: ACR = American College of Rheumatology; bDMARD = biologic disease-modifying anti-rheumatic drug; CRP = c-reactive protein; cDMARDs = conventional disease-modifying anti-rheumatic drugs; HAQ-DI = Health Assessment Questionnaire Disability Index; IR = inadequate responder; MTX = methotrexate; PBO = placebo
a Data shown are mean (standard deviation).
b Primary efficacy timepoint is at Week 14.
c Visual analog scale: 0 = best, 100 = worst.
d Health Assessment Questionnaire-Disability Index: 0=best, 3=worst; 20 questions; 8 categories: dressing and grooming, arising, eating, walking, hygiene, reach, grip, and activities.

Figure 1. Percent of Patients Achieving ACR20 in Trial RA-IV

Abbreviations: ACR20 = American College of Rheumatology ≥20% improvement; MTX = methotrexate
Patients who discontinued randomized treatment, or were missing ACR20 results, or were lost-to-follow-up or withdrawn from the trial were imputed as non-responders.

In RA-I and RA-IV, a higher proportion of patients treated with RINVOQ 15 mg alone or in combination with MTX, achieved DAS28-CRP < 2.6 compared to MTX or placebo at the primary efficacy timepoint (Table 15).

Table 15: Proportion of Patients with DAS28-CRP Less Than 2.6 with Number of Residual Active Joints at Primary Efficacy Timepoint
 | Trial RA-I MTX-naïve
 | Monotherapy
DAS28-CRP Less Than 2.6 | MTX N = 314 | RINVOQ 15 mg N = 317
Proportion of responders at Week 12 (n) | 14% (43) | 36% (113)
Of responders, proportion with 0 active joints (n) | 51% (22) | 45% (51)
Of responders, proportion with 1 active joint (n) | 35% (15) | 23% (26)
Of responders, proportion with 2 active joints (n) | 9% (4) | 17% (19)
Of responders, proportion with 3 or more active joints (n) | 5% (2) | 15% (17)
 | Trial RA-IV MTX-IR
 | Background MTX
DAS28-CRP Less Than 2.6 | PBO N = 651 | RINVOQ 15 mg N = 651
Proportion of responders at Week 12 (n) | 6% (40) | 29% (187)
Of responders, proportion with 0 active joints (n) | 60% (24) | 48% (89)
Of responders, proportion with 1 active joint (n) | 20% (8) | 23% (43)
Of responders, proportion with 2 active joints (n) | 15% (6) | 13% (25)
Of responders, proportion with 3 or more active joints (n) | 5% (2) | 16% (30)
Abbreviations: CRP = c-reactive protein; DAS28 = Disease Activity Score 28 joints; MTX = methotrexate; PBO = placebo; IR = inadequate responder

Radiographic Response

Inhibition of progression of structural joint damage was assessed using the modified Total Sharp Score (mTSS) and its components, the erosion score and joint space narrowing score, at Week 26 in Trial RA-IV and Week 24 in Trial RA-I. The proportion of patients with no radiographic progression (mTSS change from baseline ≤ 0) was also assessed.

In Trial RA-IV, treatment with RINVOQ 15 mg inhibited the progression of structural joint damage compared to placebo in combination with cDMARDs at Week 26 (Table 16). Analyses of erosion and joint space narrowing scores were consistent with overall results.

In the placebo plus MTX group, 76% of the patients experienced no radiographic progression at Week 26 compared to 83% of the patients treated with RINVOQ 15 mg.

In Trial RA-I, treatment with RINVOQ 15 mg monotherapy inhibited the progression of structural joint damage compared to MTX monotherapy at Week 24 (Table 16). Analyses of erosion and joint space narrowing scores were consistent with overall results.

In the MTX monotherapy group, 78% of the patients experienced no radiographic progression at Week 24 compared to 87% of the patients treated with RINVOQ 15 mg monotherapy.

Table 16: Radiographic Changes
 | Trial RA-IV MTX-IR
 | Background MTX
mTSS | PBO (N=651) Mean (SD) | RINVOQ 15 mg (N=651) Mean (SD) | Estimated Difference vs PBO at Week 26 (95% CI)a
Baseline | 35.9 (52) | 34.0 (50)
Week 26b | 0.78 (0.1) | 0.15 (0.1) | -0.63 (-0.92, -0.34)
 | Trial RA-I MTX-naïve
 | Monotherapy
 | MTX (N=309) Mean (SD) | RINVOQ 15 mg (N=309) Mean (SD) | Estimated Difference vs MTX at Week 24 (95% CI)c
Baseline | 13.3 (31) | 18.1 (38)
Week 24d | 0.67 (2.8) | 0.14 (1.4) | -0.53 (-0.85, -0.20)
Abbreviations: mTSS = modified Total Sharp Score, MTX = methotrexate; PBO = placebo; SD = standard deviation; IR = inadequate responders; bDMARDs = biologic disease modifying anti-rheumatic drugs; LS = least squares; CI = confidence intervals
a LS means and 95% CI based on a random coefficient model fit to the mTSS value adjusting for time, treatment group, prior bDMARDs use, treatment group-by-time interaction, with random slopes and random intercept.
b Estimated linear rate of structural progression by Week 26 and standard errors are presented.
c LS means and 95% CI based on a linear regression model fit to change from baseline in mTSS adjusting for treatment group, baseline mTSS, and geographic region.
d Mean change from baseline and standard deviation are presented.

Physical Function Response

Treatment with RINVOQ 15 mg, alone or in combination with cDMARDs, resulted in a greater improvement in physical function at Week 12/14 compared to all comparators as measured by HAQ-DI.

Other Health-Related Outcomes

In all trials except for Trial RA-V, patients receiving RINVOQ 15 mg had greater improvement from baseline in physical component summary (PCS) score, mental component summary (MCS) scores, and in all 8 domains of the Short Form Health Survey (SF-36) compared to placebo in combination with cDMARDs or MTX monotherapy at Week 12/14.

Fatigue was assessed by the Functional Assessment of Chronic Illness Therapy-Fatigue score (FACIT-F) in Trials RA-I, RA-III, and RA-IV. Improvement in fatigue at Week 12 was observed in patients treated with RINVOQ 15 mg compared to patients on placebo in combination with cDMARDs or MTX monotherapy.

14.2 Psoriatic Arthritis

The efficacy and safety of RINVOQ 15 mg once daily were assessed in two Phase 3 randomized, double-blind, multicenter, placebo-controlled trials in patients 18 years of age or older with moderately to severely active psoriatic arthritis. All patients had active psoriatic arthritis for at least 6 months based upon the Classification Criteria for Psoriatic Arthritis (CASPAR), at least 3 tender joints and at least 3 swollen joints, and active plaque psoriasis or history of plaque psoriasis. Although another dose has been studied, the recommended dose of RINVOQ is 15 mg once daily for psoriatic arthritis.

Trial PsA-I (NCT03104400) was a 24-week trial in 1705 patients with moderately to severely active psoriatic arthritis who had an inadequate response or intolerance to at least one non-biologic DMARD. Patients received RINVOQ 15 mg or upadacitinib 30 mg once daily, adalimumab, or placebo, alone or in combination with background non-biologic DMARDs. At Week 24, all patients randomized to placebo were switched to RINVOQ 15 mg or upadacitinib 30 mg once daily in a blinded manner. The primary endpoint was the proportion of patients who achieved an ACR20 response at Week 12.

Trial PsA-II (NCT03104374) was a 24-week trial in 642 patients with moderately to severely active psoriatic arthritis who had an inadequate response or intolerance to at least one biologic DMARD. Patients received RINVOQ 15 mg or upadacitinib 30 mg once daily or placebo, alone or in combination with background non-biologic DMARDs. At Week 24, all patients randomized to placebo were switched to RINVOQ 15 mg or upadacitinib 30 mg once daily in a blinded manner. The primary endpoint was the proportion of patients who achieved an ACR20 response at Week 12.

Clinical Response

In both trials, patients treated with RINVOQ 15 mg achieved significantly higher ACR20 responses compared to placebo at Week 12 (Table 17, Figure 2). A higher proportion of patients treated with RINVOQ 15 mg achieved ACR50 and ACR70 responses at Week 12 compared to placebo.

Treatment with RINVOQ 15 mg resulted in improvements in the ACR components compared to placebo at the primary efficacy timepoint (Table 18).

Table 17: Clinical Response
Trial | Trial PsA-I non-biologic DMARD-IR |  | Trial PsA-II bDMARD-IR
Treatment Group | PBO % | RINVOQ 15 mg % Δ (95% CI) | PBO % | RINVOQ 15 mg % Δ (95% CI)
N | 423 | 429 | 212 | 211
ACR20
Week 12 | 36 | 71 35 (28, 41) | 24 | 57 33 (24, 42)
ACR50
Week 12 | 13 | 38 24 (19, 30) | 5 | 32 27 (20, 34)
ACR70
Week 12 | 2 | 16 13 (10, 17) | 1 | 9 8 (4, 12)
Abbreviations: ACR20 (or 50 or 70) = American College of Rheumatology ≥20% (or ≥50% or ≥70%) improvement, bDMARD = biologic disease-modifying anti-rheumatic drug; IR = inadequate responder; PBO = placebo
Patients who discontinued randomized treatment or were missing data at week of evaluation were imputed as non-responders in the analyses.

Table 18: Components of ACR Responsea
Trial | Trial PsA-I non-biologic DMARD-IR |  | Trial PsA-II bDMARD-IR
Treatment Group | PBO (N=423) | RINVOQ 15 mg (N=429) | PBO (N=212) | RINVOQ 15 mg (N=211)
Number of tender/painful joints (0-68)
Baseline | 20.0 (14.3) | 20.4 (14.7) | 25.3 (17.6) | 24.9 (17.3)
Week 12 | 12.5 (13.3) | 8.8 (12.5) | 19.3 (18.5) | 12.6 (15.6)
Number of swollen joints (0-66)
Baseline | 11.0 (8.2) | 11.6 (9.3) | 12.0 (8.9) | 11.3 (8.2)
Week 12 | 5.6 (7.2) | 3.5 (6.0) | 7.3 (9.4) | 4.4 (5.7)
Patient assessment of painb
Baseline | 6.1 (2.1) | 6.2 (2.1) | 6.6 (2.1) | 6.4 (2.1)
Week 12 | 5.1 (2.3) | 3.8 (2.4) | 5.9 (2.3) | 4.4 (2.5)
Patient global assessmentb
Baseline | 6.3 (2.0) | 6.6 (2.0) | 6.8 (2.0) | 6.8 (1.9)
Week 12 | 5.2 (2.2) | 3.8 (2.3) | 6.1 (2.3) | 4.5 (2.5)
Disability index (HAQ-DI) c
Baseline | 1.1 (0.6) | 1.2 (0.7) | 1.2 (0.7) | 1.1 (0.6)
Week 12 | 1.0 (0.7) | 0.7 (0.6) | 1.1 (0.6) | 0.8 (0.7)
Physician global assessmentb
Baseline | 6.5 (1.6) | 6.7 (1.6) | 6.5 (1.8) | 6.5 (1.8)
Week 12 | 4.3 (2.2) | 3.1 (2.0) | 5.0 (2.2) | 3.4 (2.1)
hsCRP (mg/L)
Baseline | 11.5 (15.8) | 11.0 (14.9) | 10.4 (18.5) | 11.2 (18.6)
Week 12 | 10.1 (15.2) | 4.2 (9.9) | 9.4 (13.4) | 4.3 (7.9)
Abbreviations: ACR = American College of Rheumatology; hsCRP = high sensitivity c-reactive protein; HAQ-DI = Health Assessment Questionnaire-Disability Index; IR = inadequate responder; PBO = placebo
a Data shown are mean (standard deviation).
b Numeric rating scale (NRS): 0 = best, 10 = worst
c Health Assessment Questionnaire-Disability Index: 0=best, 3=worst; 20 questions; 8 categories: dressing and grooming, arising, eating, walking, hygiene, reach, grip, and activities.

The percentage of patients achieving ACR20 response by visit is shown in Figure 2.

Figure 2. Percent of Patients Achieving ACR20 in Trial PsA-II

Abbreviations: ACR20 = American College of Rheumatology ≥20% improvement Patients who discontinued randomized treatment, or were missing ACR20 results, or were lost-to-follow-up or withdrawn from the trial were imputed as non-responders.

Treatment with RINVOQ 15 mg resulted in improvement in dactylitis and enthesitis in patients with pre-existing dactylitis or enthesitis.

Treatment with RINVOQ 15 mg resulted in improvement in skin manifestations in patients with PsA. However, RINVOQ has not been studied in and is not indicated for the treatment of plaque psoriasis.

Physical Function Response

In both trials, patients treated with RINVOQ 15 mg showed significant improvement in physical function from baseline compared to placebo as assessed by HAQ-DI at Week 12 (Table 17). The mean difference (95% CI) from placebo in HAQ-DI change from baseline at Week 12 was -0.28 (-0.35, -0.22) in Trial PsA-I and -0.21 (-0.30, -0.12) in Trial PsA-II.

The proportion of HAQ-DI responders (≥ 0.35 improvement from baseline in HAQ-DI score) at Week 12 in Trial PsA-I and Trial PsA-II was 58% and 45%, respectively, in patients receiving RINVOQ 15 mg and 33% and 27%, respectively, in patients receiving placebo.

Radiographic Response

In Trial PsA-I, inhibition of progression of structural damage was assessed radiographically and expressed as the change from baseline in modified Total Sharp Score (mTSS) and its components, the erosion score and the joint space narrowing score, at Week 24.

Treatment with RINVOQ 15 mg inhibited progression of structural joint damage compared to placebo at Week 24 (Table 19). Analyses of erosion and joint space narrowing scores were consistent with overall results. The proportion of patients with no radiographic progression (mTSS change ≤ 0) at Week 24 was 93% in patients receiving RINVOQ 15 mg and 89% in patients receiving placebo.

Table 19: Radiographic Changes in Trial PsA-I
 | PBO (N=392) Mean (SD) | RINVOQ 15 mg (N=407) Mean (SD) | Estimated Difference vs PBO at Week 24 (95% CI)a
mTSS
Baseline | 13.32 (31.2) | 13.14 (42.4)
Week 24b | 0.23 (0.07) | -0.02 (0.04) | -0.25 (-0.41, -0.09)
Abbreviations: CI = confidence intervals; LS = least squares; mTSS = modified Total Sharp Score; PBO = placebo; SD = standard deviation
a LS means and 95% CI based on a random coefficient model fit to the mTSS value adjusting for time, treatment group, current DMARD use (yes/no), treatment group-by-time interaction, with random slopes and random intercept.
b Estimated linear rate of structural progression by Week 24 and standard errors are presented.

Other Health-Related Outcomes

Health-related quality of life was assessed by SF-36. In both trials, patients receiving RINVOQ 15 mg experienced significantly greater improvement from baseline in the Physical Component Summary score compared to placebo at Week 12. Greater improvement was also observed in the Mental Component Summary score and all 8 domains of SF-36 compared to placebo.

Patients receiving RINVOQ 15 mg showed greater improvement from baseline in fatigue, as measured by FACIT-F score, at Week 12 compared to placebo in both trials.

14.3 Atopic Dermatitis

The efficacy of RINVOQ 15 mg and 30 mg once daily, was assessed in three Phase 3 randomized, double-blind, multicenter trials (AD-1, AD-2, AD-3; NCT03569293, NCT03607422, and NCT03568318, respectively) in a total of 2584 patients (12 years of age and older). RINVOQ was evaluated in 344 pediatric patients and 2240 adult patients with moderate to severe atopic dermatitis (AD) not adequately controlled by topical medication(s).

Disease severity at baseline was defined by a validated Investigator's Global Assessment (vIGA-AD) score ≥3 in the overall assessment of AD on a severity scale of 0 to 4, an Eczema Area and Severity Index (EASI) score ≥16, a minimum body surface area (BSA) involvement of ≥10%, and weekly average Worst Pruritus Numerical Rating Scale (NRS) score ≥4. Overall, 57% of the patients were male and 69% were white. The mean age at baseline was 34 years (ranged from 12 to 75 years) and 13% of the patients were 12 to less than 18 years. At baseline, 49% of patients had a vIGA-AD score of 3 (moderate AD), and 51% of patients had a vIGA-AD score of 4 (severe AD). The baseline mean EASI score was 29 and the baseline weekly average Worst Pruritus NRS score was 7. Approximately 52% of the patients had prior exposure to systemic AD treatment.

In all three trials, patients received RINVOQ once daily oral doses of 15 mg, 30 mg, or matching placebo for 16 weeks. In Trial AD-3, patients also received RINVOQ or placebo with concomitant topical corticosteroids (TCS) for 16 weeks.

All three trials assessed the co-primary endpoints of the proportion of patients with a vIGA-AD score of 0 (clear) or 1 (almost clear) with at least a 2-point improvement and the proportion of patients with EASI-75 (improvement of at least 75% in EASI score from baseline) at Week 16. Secondary endpoints included EASI-90 and EASI-100 at Week 16, and the proportion of patients with reduction in itch (≥4-point improvement from baseline in the Worst Pruritus NRS) at Weeks 1, 4, and 16. In Trials AD-1 and AD-2, the proportion of patients with reduction in pain (≥4-point improvement in the Atopic Dermatitis Symptom Scale [ADerm-SS] Skin Pain NRS) from baseline to Week 16 was a secondary endpoint.

Clinical Response

Monotherapy Trials (AD-1 and AD-2)

The results of RINVOQ monotherapy trials (AD-1 and AD-2) are presented in Table 20. Figure 3 presents the proportion of patients with ≥ 4-point improvement in Worst Pruritus NRS at Weeks 1, 4, and 16 for Trials AD-1 and AD-2.

Table 20: Efficacy Results of Monotherapy Trials at Week 16 in Patients with Moderate to Severe AD
 | Trial AD-1 |  |  | Trial AD-2
 | PBO | RINVOQ 15 mg | RINVOQ 30 mg | PBO | RINVOQ 15 mg | RINVOQ 30 mg
Number of patients randomized | 281 | 281 | 285 | 278 | 276 | 282
vIGA-AD 0/1a,b | 8% | 48% | 62% | 5% | 39% | 52%
Difference from PBO (95% CI) |  | 40% (33%, 46%) | 54% (47%, 60%) |  | 34% (28%, 40%) | 47% (41%, 54%)
EASI-75a | 16% | 70% | 80% | 13% | 60% | 73%
Difference from PBO (95% CI) |  | 53% (46%, 60%) | 63% (57%, 70%) |  | 47% (40%, 54%) | 60% (53%, 66%)
EASI-90a | 8% | 53% | 66% | 5% | 42% | 58%
Difference from PBO (95% CI) |  | 45% (39%, 52%) | 58% (51%, 64%) |  | 37% (31%, 43%) | 53% (47%, 59%)
EASI-100a | 2% | 17% | 27% | 1% | 14% | 19%
Difference from PBO (95% CI) |  | 15% (10%, 20%) | 25% (20%, 31%) |  | 13% (9%, 18%) | 18% (13%, 23%)
Number of patients with baseline Worst Pruritus NRS score ≥ 4 | 272 | 274 | 280 | 274 | 270 | 280
≥ 4-point improvement in Worst Pruritus NRSc | 12% | 52% | 60% | 9% | 42% | 60%
Difference from PBO (95% CI) |  | 40% (33%, 48%) | 48% (41%, 55%) |  | 33% (26%, 39%) | 50% (44%, 57%)
Number of patients with baseline ADerm-SS Skin Pain NRS score ≥ 4 | 233 | 237 | 249 | 247 | 237 | 238
≥ 4-point improvement in ADerm-SS Skin Pain NRSd | 15% | 54% | 63% | 13% | 49% | 65%
Difference from PBO (95% CI) |  | 39% (31%, 47%) | 49% (41%, 56%) |  | 36% (28%, 43%) | 52% (44%, 59%)
Abbreviations: ADerm-SS = Atopic Dermatitis Symptom Scale; PBO = placebo
a Based on number of patients randomized
b Responder was defined as a patient with vIGA-AD 0 or 1 (“clear” or “almost clear”) with a reduction of ≥ 2 points on a 0-4 ordinal scale
c Based on number of patients whose baseline Worst Pruritus NRS is ≥ 4
d Based on number of patients whose baseline ADerm-SS Skin Pain NRS is ≥ 4

Figure 3. Proportion of Patients with Moderate to Severe AD with ≥4-point Improvement in the Worst Pruritus NRS in Monotherapy Trials

Examination of age, gender, race, weight, and prior systemic treatment with immunosuppressants did not identify differences in response to RINVOQ among these subgroups in Trials AD-1 and AD-2.

Concomitant TCS Trial (AD-3)

The results of the RINVOQ with concomitant TCS trial (AD-3) are presented in Table 21. Figure 4 presents the proportion of patients with ≥ 4-point improvement in Worst Pruritus NRS at Weeks 1, 4, and 16 for Trial AD-3.

Table 21: Efficacy Results with Concomitant TCS at Week 16 in Patients with Moderate to Severe AD
 | Trial AD-3
 | PBO + TCS | RINVOQ 15 mg + TCS | RINVOQ 30 mg + TCS
Number of patients randomized | 304 | 300 | 297
vIGA-AD 0/1a,b | 11% | 40% | 59%
Difference from PBO (95% CI) |  | 29% (22%, 35%) | 48% (41%, 54%)
EASI-75a, | 26% | 65% | 77%
Difference from PBO (95% CI) |  | 38% (31%, 45%) | 51% (44%, 57%)
EASI-90a | 13% | 43% | 63%
Difference from PBO (95% CI) |  | 30% (23%, 36%) | 50% (43%, 56%)
EASI-100a | 1% | 12% | 23%
Difference from PBO (95% CI) |  | 11% (7%, 14%) | 21% (16%, 26%)
Number of patients with baseline Worst Pruritus NRS score ≥ 4 | 294 | 288 | 291
≥ 4-point improvement in Worst Pruritus NRSc | 15% | 52% | 64%
Difference from PBO (95% CI) |  | 37% (30%, 44%) | 49% (42%, 56%)
Abbreviations: PBO = placebo
a Based on number of patients randomized
b Responder was defined as a patient with vIGA-AD 0 or 1 (“clear” or “almost clear”) with a reduction of ≥ 2 points on a 0-4 ordinal scale
c Based on number of patients whose baseline Worst Pruritus NRS is ≥ 4

Figure 4. Proportion of Patients with Moderate to Severe AD with ≥4-point Improvement in the Worst Pruritus NRS in Concomitant TCS Trial

Examination of age, gender, race, weight, and prior systemic treatment with immunosuppressants did not identify differences in response to RINVOQ among these subgroups in Trial AD-3.

Pediatric Patient Population

The efficacy results of the RINVOQ monotherapy trials (AD-1 and AD-2) and the RINVOQ with concomitant TCS trial (AD-3) at Week 16 for pediatric patients 12 years of age and older are presented in Table 22 and Table 23, respectively.

Table 22: Efficacy Results of Monotherapy Trials for Pediatric Patients 12 Years of Age and Older with Moderate to Severe AD at Week 16
 | Trial AD-1 |  |  | Trial AD-2
 | PBO | RINVOQ 15 mg | RINVOQ 30 mg | PBO | RINVOQ 15 mg | RINVOQ 30 mg
Number of pediatric patients randomized | 40 | 42 | 42 | 36 | 33 | 35
vIGA-AD 0/1a,b | 8% | 38% | 69% | 3% | 42% | 62%
Difference from PBO (95% CI) |  | 31% (14%, 47%) | 62% (45%, 78%) |  | 40% (22%, 57%) | 60% (42%, 77%)
EASI-75a | 8% | 71% | 83% | 14% | 67% | 74%
Difference from PBO (95% CI) |  | 63% (47%, 79%) | 75% (61%, 89%) |  | 53% (33%, 72%) | 61% (42%, 79%)
Number of pediatric patients with baseline Worst Pruritus NRS score ≥ 4 | 39 | 40 | 42 | 36 | 30 | 34
≥ 4-point improvement in Worst Pruritus NRSc | 15% | 45% | 55% | 3% | 33% | 50%
Difference from PBO (95% CI) |  | 30% (10%, 49%) | 39% (21%, 58%) |  | 31% (13%, 48%) | 47% (30%, 65%)
Abbreviations: PBO = placebo
a Based on number of pediatric patients randomized
b Responder was defined as a patient with vIGA-AD 0 or 1 (“clear” or “almost clear”) with a reduction of ≥ 2 points on a 0-4 ordinal scale
c Based on number of pediatric patients whose baseline Worst Pruritus NRS is ≥ 4

Table 23: Efficacy Results with Concomitant TCS for Pediatric Patients 12 Years of Age and Older with Moderate to Severe AD at Week 16
 | Trial AD-3
 | PBO + TCS | RINVOQ 15 mg + TCS | RINVOQ 30 mg + TCS
Number of pediatric patients randomized | 40 | 39 | 37
vIGA-AD 0/1a,b | 8% | 31% | 65%
Difference from PBO (95% CI) |  | 23% (7%, 40%) | 57% (40%, 75%)
EASI-75a | 30% | 56% | 76%
Difference from PBO (95% CI) |  | 26% (5%, 47%) | 46% (26%, 65%)
Number of pediatric patients with baseline Worst Pruritus NRS score ≥ 4 | 38 | 36 | 33
≥ 4-point improvement in Worst Pruritus NRSc | 13% | 42% | 55%
Difference from PBO (95% CI) |  | 29% (9%, 48%) | 41% (21%, 61%)
Abbreviations: PBO = placebo
a Based on number of pediatric patients randomized
b Responder was defined as a patient with vIGA-AD 0 or 1 (“clear” or “almost clear”) with a reduction of ≥ 2 points on a 0-4 ordinal scale
c Based on number of pediatric patients whose baseline Worst Pruritus NRS is ≥ 4

14.4 Ulcerative Colitis

Induction Trials (Study UC-1 and Study UC-2)

In two identical induction trials (UC-1; NCT02819635 and UC-2; NCT03653026), patients were randomized 2:1 to receive either RINVOQ 45 mg once daily or placebo for 8 weeks. A total of 988 patients were analyzed across the two trials. These trials included adult patients with moderately to severely active ulcerative colitis who had an inadequate response, loss of response, or intolerance to oral aminosalicylates, corticosteroids, immunosuppressants, and/or biologic therapy. Enrolled patients were permitted to use stable doses of oral aminosalicylates, methotrexate, ulcerative colitis-related antibiotics, and/or oral corticosteroids (up to 30 mg/day prednisone or equivalent). At baseline, 38% of patients were receiving corticosteroids, and 68% of patients were receiving aminosalicylates. Concomitant biologic therapies, azathioprine, 6-mercaptopurine, intravenous or rectal corticosteroids were prohibited. A total of 51% of patients had previously failed treatment with or were intolerant to at least one biologic therapy. RINVOQ is indicated for patients who have an inadequate response or intolerance to one or more TNF blockers [see Indications and Usage (1.4)].

Disease activity was assessed on the modified Mayo score (mMS), a 3-component Mayo score (0-9) which consists of the following subscores (0 to 3 for each subscore): stool frequency (SFS), rectal bleeding (RBS), and findings on centrally read endoscopy score (ES). An ES of 2 was defined by marked erythema, lack of vascular pattern, any friability, and/or erosions, and a score of 3 was defined by spontaneous bleeding and ulceration. Enrolled patients had a mMS between 5 to 9 with an ES of 2 or 3; at baseline the median mMS was 7, with 61% of patients having a baseline mMS of 5 to 7 and 39% having a mMS of 8 to 9.

At baseline, 39% and 37% of patients received corticosteroids, 1% and 1% of patients received methotrexate, and 68% and 69% of patients received aminosalicylates in UC-1 and UC-2, respectively. Patient disease activity was moderate (mMS ≤7) in 61% and 60% of patients and severe (mMS >7) in 39% and 40% of patients in UC-1 and UC-2, respectively.

The primary endpoint was clinical remission defined using the mMS at Week 8. Secondary endpoints included clinical response, endoscopic improvement, and histologic endoscopic mucosal improvement (see Table 24 and Table 25).

Table 24: Proportion of Patients Meeting Primary and Key Secondary Efficacy Endpoints at Week 8 - Study UC-1
Study UC-1
Endpoint | Placebo | RINVOQ 45 mg Once Daily | Treatment Difference vs Placebo (95% CI)
Clinical Remissiona
Total Population | N=154 5% | N=319 26% | 22%b (16, 27)
Prior biologic failurec | N=78 < 1% | N=168 18%
Without prior biologic failure | N=76 9% | N=151 35%
Clinical Responsed
Total Population | N=154 27% | N=319 73% | 46%b (38, 54)
Prior biologic failurec | N=78 13% | N=168 64%
Without prior biologic failure | N=76 42% | N=151 82%
Endoscopic Improvemente
Total Population | N=154 7% | N=319 36% | 29%b (23, 36)
Prior biologic failurec | N=78 2% | N=168 27%
Without prior biologic failure | N=76 13% | N=151 47%
Histologic Endoscopic Mucosal Improvementf
Total Population | N=154 7% | N=319 30% | 24%b (17, 30)
Prior biologic failurec | N=78 1% | N=168 23%
Without prior biologic failure | N=76 12% | N=151 38%
a Per mMS: SFS ≤1 and not greater than baseline, RBS = 0, ES of ≤ 1 without friability
b p <0.001, adjusted treatment difference (95% CI) based on Cochran-Mantel-Haenszel method adjusted for randomization stratification factors
c Prior biologic failure includes inadequate response, loss of response, or intolerance to one or more biologic treatments for ulcerative colitis.
d Per mMS: decrease ≥ 2 points and ≥ 30% from baseline and a decrease in RBS ≥ 1 from baseline or an absolute RBS ≤1
e ES ≤ 1 without friability
f ES ≤1 without friability and Geboes score ≤ 3.1 (indicating neutrophil infiltration in <5% of crypts, no crypt destruction and no erosions, ulcerations or granulation tissue)

Table 25: Proportion of Patients Meeting Primary and Key Secondary Efficacy Endpoints at Week 8 - Study UC-2
Study UC-2
Endpoint | Placebo | RINVOQ 45 mg Once Daily | Treatment Difference vs Placebo (95% CI)
Clinical Remissiona
Total Population | N=174 4% | N=341 33% | 29%b (23, 35)
Prior biologic failurec | N=89 2% | N=173 30%
Without prior biologic failure | N=85 6% | N=168 38%
Clinical Responsed
Total Population | N=174 25% | N=341 74% | 49%b (42, 57)
Prior biologic failurec | N=89 19% | N=173 69%
Without prior biologic failure | N=85 32% | N=168 80%
Endoscopic Improvemente
Total Population | N=174 8% | N=341 44% | 35%b (29, 42)
Prior biologic failurec | N=89 5% | N=173 37%
Without prior biologic failure | N=85 12% | N=168 51%
Histologic Endoscopic Mucosal Improvementf
Total Population | N=174 6% | N=341 37% | 30%b (24, 36)
Prior biologic failurec | N=89 5% | N=173 31%
Without prior biologic failure | N=85 7% | N=168 43%
a Per mMS: SFS ≤ 1 and not greater than baseline, RBS = 0, ES of ≤ 1 without friability
b p <0.001, adjusted treatment difference (95% CI) based on Cochran-Mantel-Haenszel method adjusted for randomization stratification factors
c Prior biologic failure includes inadequate response, loss of response, or intolerance to one or more biologic treatments for ulcerative colitis.
d Per mMS: decrease ≥ 2 points and ≥ 30% from baseline and a decrease in RBS ≥ 1 from baseline or an absolute RBS ≤1
e ES ≤ 1 without friability
f ES ≤1 without friability and Geboes score ≤ 3.1 (indicating neutrophil infiltration in <5% of crypts, no crypt destruction and no erosions, ulcerations or granulation tissue)

Studies UC-1 and UC-2 were not designed to evaluate the relationship of histologic endoscopic mucosal improvement at Week 8 to disease progression and long-term outcomes.

Rectal Bleeding and Stool Frequency Subscores

Onset of clinical response was assessed using the SFS and RBS (partial modified Mayo Score [pmMS]). Initial response was defined as a decrease of ≥1 point and ≥30% from baseline in pmMS and a decrease in RBS ≥1 or an absolute RBS≤1. Onset of response occurred as early as Week 2 in a greater proportion of patients treated with RINVOQ 45 mg once daily compared to placebo.

Endoscopic and Histologic Assessment

Normalization of the endoscopic appearance of the mucosa (endoscopic remission) was defined as ES of 0. At Week 8, a greater proportion of patients treated with RINVOQ 45 mg once daily compared to placebo achieved endoscopic remission (UC-1: 14% vs 1%, UC-2: 18% vs 2%). Endoscopic remission with Geboes histologic score < 2.0 (indicating no neutrophils in crypts or lamina propria and no increase in eosinophil, no crypt destruction, and no erosions, ulcerations, or granulation tissue) was achieved by a greater proportion of patients treated with RINVOQ 45 mg once daily compared to placebo at Week 8 (UC-1: 11% vs 1%, UC-2: 13% vs 2%).

Abdominal Pain and Bowel Urgency

A greater proportion of patients treated with RINVOQ 45 mg once daily compared to placebo had no abdominal pain (UC-1: 47% vs 23%, UC-2: 54% vs 24%) and no bowel urgency (UC-1: 48% vs 21%, UC-2: 54% vs 26%) at Week 8.

Fatigue

In Studies UC-1 and UC-2, patients treated with RINVOQ experienced a clinically meaningful improvement in fatigue, as assessed by change from baseline in FACIT-F score, at Week 8, compared to placebo-treated patients. The effect of RINVOQ to improve fatigue after 8 weeks of induction has not been established.

Maintenance Study UC-3

In UC-3 (NCT02819635), a total of 451 patients who received RINVOQ 45 mg once daily in either UC-1, UC-2 or UC-4 and achieved clinical response were re-randomized to receive RINVOQ 15 mg, 30 mg or placebo once daily for up to 52 weeks.

The primary endpoint was clinical remission defined using mMS at Week 52. Secondary endpoints included corticosteroid-free clinical remission, endoscopic improvement, and histologic endoscopic mucosal improvement (see Table 26).

Table 26: Proportion of Patients Meeting Primary and Key Secondary Efficacy Endpoints at Week 52 in Maintenance Study UC-3
Endpoint | Placebo | RINVOQ 15 mg Once Daily | Treatment Difference 15 mg vs Placebo (95% CI) | RINVOQ 30 mg Once Daily | Treatment Difference 30 mg vs Placebo (95% CI)
Clinical remissiona
Total Population | N=149 12% | N=148 42% | 31%b (22, 40) | N=154 52% | 39%b (30, 48)
Prior biologic failurec | N=81 7% | N=71 41% |  | N=73 49%
Without prior biologic failure | N=68 18% | N=77 44% |  | N=81 54%
Corticosteroid-free clinical remissiond
Total Population | N=54 22% | N=47 57% | 35%b (18, 53) | N=58 68% | 45%b (29, 62)
Prior biologic failurec | N=22 14% | N=17 71% |  | N=20 73%
Without prior biologic failure | N=32 28% | N=30 49% |  | N=38 65%
Endoscopic Improvemente
Total Population | N=149 14% | N=148 49% | 34%b (25, 44) | N=154 62% | 46%b (37, 56)
Prior biologic failurec | N=81 8% | N=71 43% |  | N=73 56%
Without prior biologic failure | N=68 22% | N=77 54% |  | N=81 67%
Histologic Endoscopic Mucosal Improvementf
Total Population | N=149 12% | N=148 35% | 24%b (15, 33) | N=154 50% | 37%b (28, 47)
Prior biologic failurec | N=81 5% | N=71 33% |  | N=73 48%
Without prior biologic failure | N=68 20% | N=77 37% |  | N=81 52%
a Per mMS: SFS ≤1 and not greater than baseline, RBS = 0, ES ≤1 without friability
b p <0.001, adjusted treatment difference (95% CI) based on Cochran-Mantel-Haenszel method adjusted for randomization stratification factors
c Prior biologic failure includes inadequate response, loss of response, or intolerance to one or more biologic treatments for ulcerative colitis.
d Clinical remission per mMS at Week 52 and corticosteroid free for ≥90 days immediately preceding Week 52 among patients who achieved clinical remission at the end of the induction treatment
e ES ≤ 1 without friability
f ES ≤1 without friability and Geboes score ≤ 3.1 (indicating neutrophil infiltration in <5% of crypts, no crypt destruction and no erosions, ulcerations or granulation tissue)

The relationship between histologic endoscopic mucosal improvement at Week 52 and disease progression and longer-term outcomes after Week 52 was not evaluated in Study UC-3.

Endoscopic and Histologic Assessment

Normalization of the endoscopic appearance of the mucosa (endoscopic remission) was defined as ES of 0. In UC-3, a greater proportion of patients treated with RINVOQ 15 mg and 30 mg once daily compared to placebo achieved endoscopic remission at Week 52 (24% and 26% vs 6%). Endoscopic remission with Geboes histologic score < 2.0 was achieved by a greater proportion of patients treated with RINVOQ 15 mg and 30 mg once daily compared to placebo at Week 52 (18% and 19% vs 5%).

Abdominal Pain and Bowel Urgency

At Week 52, a greater proportion of patients treated with RINVOQ 15 mg and 30 mg once daily compared to placebo had no abdominal pain (46%, 55% and 21%, respectively) and no bowel urgency (56%, 64% and 17%, respectively).

14.5 Crohn’s Disease

Induction Trials (Studies CD-1 and CD-2)

In two induction trials, CD-1 (NCT03345836) and CD-2 (NCT03345849), patients were randomized 2:1 to receive RINVOQ 45 mg or placebo once daily for 12 weeks. Efficacy was assessed in a population of 857 patients (419 patients in CD-1 and 438 patients in CD-2) with moderately to severely active Crohn’s disease (CD), with baseline Crohn’s Disease Activity Index (CDAI) score of at least 220 and centrally-reviewed Simple Endoscopic Score for Crohn’s Disease (SES-CD) of ≥ 6, or ≥ 4 for isolated ileal disease, excluding the narrowing component. In CD-1, all patients had inadequate response or were intolerant to treatment with one or more biological therapies (prior biologic failure). In CD-2, 45% (197/438) of patients had inadequate response or were intolerant to treatment with one or more biological therapies (prior biologic failure). Enrolled patients in both studies were permitted to use stable doses of CD-related antibiotics, aminosalicylates, or methotrexate. Concomitant corticosteroids (up to 30 mg/day prednisone or equivalent) were permitted at enrollment; tapering was initiated at Week 4.

In CD-1, patients had a mean age of 37 years (range 18 to 74 years); 46% were female; and 72% identified as White, 21% as Asian, 6% as Black or African American, 0.5% as American Indian or Alaska Native, and 0.5% as multiple racial groups. In CD-2, patients had a mean age of 40 years (range of 18 to 74 years); 45% were female; 74% identified as White, 20% as Asian, 4% as Black or African American, and 2% as multiple racial groups.

At baseline, 36% and 37% of patients received corticosteroids, 7% and 3% of patients received methotrexate, 15% and 24% of patients received aminosalicylates, and 2% and 1% of patients received CD-related antibiotics in CD-1 and CD-2, respectively.

The co-primary endpoints were the proportion of patients achieving clinical remission (by CDAI) at Week 12, and the proportion of patients achieving endoscopic response (by SES-CD) at Week 12. Secondary efficacy endpoints included clinical response, corticosteroid-free remission, and endoscopic remission (see Table 27 and Table 28).

Table 27: Proportion of Patients Meeting Primary and Additional Efficacy Endpoints in Induction Study CD-1
CD-1
Endpoint | Placebo | RINVOQ 45 mg Once Daily | Treatment Difference vs Placebo (95% CI)
Co-Primary Endpoints at Week 12
Clinical remissiona | N=146 18% | N=273 36% | 17% (9, 25)*
Endoscopic responseb | N=146 3% | N=273 34% | 30% (24, 36)*
Additional Endpoints at Week 12
Clinical response (CR-100) c | N=146 31% | N=273 54% | 22% (13, 31)*
Corticosteroid-free clinical remission in patients on corticosteroids at baselinea,d | N=53 11% | N=96 30% | 17% (5, 29)**
Endoscopic remissione | N=146 3% | N=273 19% | 15% (10, 21)*
* p < 0.001, adjusted treatment difference (95% CI) based on Cochran-Mantel-Haenszel method adjusted for randomization stratification factors
** p < 0.01, adjusted treatment difference (95% CI) based on Cochran-Mantel-Haenszel method adjusted for randomization stratification factors
a CDAI < 150
b Decrease in SES-CD > 50% from baseline of the induction study (or for patients with an SES-CD of 4 at baseline of the induction study, at least a 2-point reduction from baseline of the induction study)
c Decrease of at least 100 points in CDAI from baseline
d Discontinuation of corticosteroid and achievement of clinical remission among patients on corticosteroid at baseline
e SES-CD ≤ 4 and no individual subscore >1 in any individual variable

Table 28: Proportion of Patients Meeting Primary and Additional Efficacy Endpoints in Induction Study CD-2
CD-2
Endpoint | Placebo | RINVOQ 45 mg Once Daily | Treatment Difference vs Placebo (95% CI)
Co-Primary Endpoints at Week 12
Clinical remissiona
Total population | N=143 23% | N=295 46% | 24% (15, 32)*
Prior biologic failure | N=62 7% | N=135 42%
Without prior biologic failure | N=81 35% | N=160 50%
Endoscopic responseb
Total population | N=143 13% | N=295 46% | 33% (26, 41)*
Prior biologic failure | N=62 10% | N=135 39%
Without prior biologic failure | N=81 15% | N=160 51%
Additional Endpoints at Week 12
Clinical response (CR-100) c
Total population | N=143 40% | N=295 64% | 24% (15, 33)*
Prior biologic failure | N=62 25% | N=135 66%
Without prior biologic failure | N=81 52% | N=160 62%
Corticosteroid-free clinical remission in patients on CS at baselinea,d
Total population | N=54 13% | N=108 40% | 27% (14, 39)*
Prior biologic failure | N=29 7% | N=60 35%
Without prior biologic failure | N=25 20% | N=48 46%
Endoscopic remissione
Total population | N=143 8% | N=295 30% | 22% (16, 29)*
Prior biologic failure | N=62 3% | N=135 22%
Without prior biologic failure | N=81 11% | N=160 37%
* p < 0.001, adjusted treatment difference (95% CI) based on Cochran-Mantel-Haenszel method adjusted for randomization stratification factors
a CDAI < 150
b Decrease in SES-CD > 50% from baseline of the induction study (or for patients with an SES-CD of 4 at baseline of the induction study, at least a 2-point reduction from baseline of the induction study)
c Decrease of at least 100 points in CDAI from baseline
d Discontinuation of corticosteroid and achievement of clinical remission among patients on corticosteroid at baseline
e SES-CD ≤ 4 and no individual subscore >1 in any individual variable

Onset of clinical response based on CDAI was observed as early as two weeks in Studies CD-1 and CD-2, with a greater proportion of patients achieving clinical response at Week 2 in RINVOQ-treated patients compared with placebo.

In Studies CD-1 and CD-2, reductions in stool frequency and abdominal pain were observed in a greater proportion of patients treated with RINVOQ 45 mg induction regimen compared to placebo at Week 12.

In Studies CD-1 and CD-2, patients treated with RINVOQ experienced a clinically meaningful improvement in fatigue, assessed by change from baseline in FACIT-F score, at Week 12, compared to placebo-treated patients. The effect of RINVOQ to improve fatigue after 12 weeks of induction has not been established.

Maintenance Study (CD-3)

The efficacy analysis for CD-3 (NCT03345823) evaluated 343 patients who responded to 12 weeks of RINVOQ 45 mg once daily induction treatment. Patients were re-randomized to receive a maintenance regimen of either RINVOQ 15 mg or 30 mg once daily or placebo for 52 weeks, representing a total of at least 64 weeks of therapy.

The co-primary endpoints of clinical remission (by CDAI) and endoscopic response (by SES-CD) were assessed at Week 52. Secondary efficacy endpoints included corticosteroid-free clinical remission, maintenance of clinical remission, endoscopic remission, and achieving both clinical and endoscopic remission, at Week 52 (see Table 29).

Table 29: Proportion of Patients Meeting Primary and Additional Efficacy Endpoints at Week 52 in Maintenance Study CD-3
Endpoint | Placebo^+ | RINVOQ 15 mg Once Daily | RINVOQ 30 mg Once Daily | Treatment Difference 15 mg vs Placebo (95% CI) | Treatment Difference 30 mg vs Placebo (95% CI)
Co-Primary Endpoints
Clinical remissiona
Total population | N=111 14% | N=113 42% | N=119 55% | 29% (18, 39)* | 40% (29, 51)*
Prior biologic failure | N=87 13% | N=85 35% | N=90 54%
Without prior biologic failure | N=24 21% | N=28 61% | N=29 55%
Endoscopic responseb
Total population | N=111 7% | N=113 28% | N=119 41% | 22% (13, 32)* | 34% (25, 44)*
Prior biologic failure | N=87 5% | N=85 22% | N=90 42%
Without prior biologic failure | N=24 17% | N=28 45% | N=29 38%
Additional Endpoints
Corticosteroid-free clinical remissionc
Total population | N=111 14% | N=113 42% | N=119 53% | 29% (18, 39)* | 38% (27, 49)*
Prior biologic failure | N=87 13% | N=85 35% | N=90 52%
Without prior biologic failure | N=24 21% | N=28 61% | N=29 55%
Maintenance of clinical remissiond
Total population | N=73 22% | N=72 51% | N=79 67% | 32% (18, 46)* | 43% (29, 57)*
Prior biologic failure | N=56 20% | N=50 46% | N=55 69%
Without prior biologic failure | N=17 29% | N=22 64% | N=24 63%
Endoscopic remissione
Total population | N=111 5% | N=113 19% | N=119 30% | 14% (6, 22)* | 25% (15, 34)*
Prior biologic failure | N=87 3% | N=85 14% | N=90 30%
Without prior biologic failure | N=24 13% | N=28 32% | N=29 31%
Clinical and endoscopic remission
Total population | N=111 4% | N=113 16% | N=119 26% | 13% (6, 21)* | 22% (14, 31)*
Prior biologic failure | N=87 2% | N=85 13% | N=90 26%
Without prior biologic failure | N=24 8% | N=28 25% | N=29 28%
^+ The placebo group consisted of patients who achieved clinical response per CDAI with RINVOQ 45 mg at the end of the induction study and were randomized to receive placebo at the start of maintenance therapy.
* p < 0.001, adjusted treatment difference (95% CI) based on Cochran-Mantel-Haenszel method adjusted for randomization stratification factors
a CDAI < 150
b Decrease in SES-CD > 50% from baseline of the induction study (or for patients with an SES-CD of 4 at baseline of the induction study, at least a 2-point reduction from baseline of the induction study)
c Corticosteroid-free for 90 days prior to Week 52 and achievement of clinical remission. Among the subset of patients who were on corticosteroids at induction baseline, 48% (N=44) in RINVOQ 15 mg group, 44% (N=45) in RINVOQ 30 mg group, and 7% (N=46) in placebo were corticosteroid-free for 90 days prior to Week 52 and in clinical remission.
d Defined as achievement of clinical remission at Week 52 in patients who achieved clinical remission at the entry of the maintenance study.
e SES-CD ≤ 4 and no subscore > 1 in any individual variable

At Week 52, reductions in stool frequency and abdominal pain were observed in a greater proportion of patients treated with RINVOQ 15 mg and 30 mg compared to placebo.

14.6 Ankylosing Spondylitis

The efficacy and safety of RINVOQ 15 mg once daily were assessed in two randomized, double-blind, multicenter, placebo-controlled trials in patients 18 years of age or older with active ankylosing spondylitis based upon the Bath Ankylosing Spondylitis Disease Activity Index (BASDAI) ≥4 and Patient’s Assessment of Total Back Pain score ≥4.

Trial AS-I (NCT03178487) was a 14-week trial in 187 ankylosing spondylitis patients with an inadequate response to at least two nonsteroidal anti-inflammatory drugs (NSAIDs) or intolerance to or contraindication for NSAIDs and had no previous exposure to biologic DMARDs. At baseline, patients had symptoms of ankylosing spondylitis for an average of 14.4 years and approximately 16% of the patients were on a concomitant cDMARD. Patients received RINVOQ 15 mg once daily or placebo. At Week 14, all patients randomized to placebo were switched to RINVOQ 15 mg once daily. The primary endpoint was the proportion of patients achieving an Assessment of SpondyloArthritis international Society 40 (ASAS40) response at Week 14.

Trial AS-II (NCT 04169373) was a 14-week trial in 420 ankylosing spondylitis patients with an inadequate response to 1 or 2 biologic DMARDs. At baseline, patients had symptoms of ankylosing spondylitis for an average of 12.8 years and approximately 31% of the patients were on a concomitant cDMARD. Patients received RINVOQ 15 mg once daily or placebo. At Week 14, all patients randomized to placebo were switched to RINVOQ 15 mg once daily. The primary endpoint was the proportion of patients achieving an Assessment of SpondyloArthritis international Society 40 (ASAS40) response at Week 14.

Clinical Response

In both trials, a significantly greater proportion of patients treated with RINVOQ 15 mg achieved an ASAS40 response compared to placebo at Week 14 (Table 30, Figure 5).

Examination of gender, baseline body mass index (BMI), and baseline hsCRP did not identify differences in response to RINVOQ among these subgroups at Week 14.

Table 30: Clinical Response at Week 14
 | Trial AS-I bDMARD-naïve |  |  | Trial AS-II bDMARD-IR
 | PBO (N=94) | RINVOQ 15 mg (N=93) | Difference from PBO (95% CI) | PBO (N=209) | RINVOQ 15 mg (N=211) | Difference from PBO (95% CI)
ASAS40 a (%) | 25.5 | 50.5 | 25 (12, 38) | 18.2 | 44.5 | 26 (18, 35)
ASAS20 a (%) | 39.4 | 63.4 | 24 (10, 38) | 38.3 | 65.4 | 27 (18, 36)
Abbreviations: ASAS20 (or 40) = Assessment of SpondyloArthritis international Society ≥20% (or ≥40%) improvement; bDMARD = biologic disease modifying anti-rheumatic drug; IR = inadequate responders; PBO = placebo
a An ASAS20 (ASAS40) response is defined as a ≥20% (≥40%) improvement and an absolute improvement from baseline of ≥1 (≥2) unit(s) (range 0 to 10) in ≥3 of 4 domains (Patient Global, Total Back Pain, Function, and Inflammation), and no worsening in the potential remaining domain (defined as worsening ≥20% and ≥1 unit for ASAS20 or defined as worsening of > 0 units for ASAS40).
For binary endpoints, Week 14 results are based on non-responder imputation (Trial AS-I) and on non-responder imputation in conjunction with multiple imputation (Trial AS-II).

Treatment with RINVOQ 15 mg resulted in improvements in the individual components of the ASAS40 response criteria compared to placebo (Table 31).

Table 31: ASAS Components and Other Measures of Disease Activitya
 | Trial AS-I bDMARD-naïve |  | Trial AS-II bDMARD-IR
Treatment Group | PBO | RINVOQ 15 mg | PBO | RINVOQ 15 mg
N | 94 | 93 | 209 | 211
Patient Global Assessment of Disease Activityb
Baseline | 6.8 (1.66) | 6.6 (1.81) | 7.2 (1.40) | 7.4 (1.48)
Week 14 | 5.4 (1.97) | 3.8 (2.44) | 5.9 (2.13) | 4.3 (2.36)
Total Back Painb
Baseline | 6.7 (1.78) | 6.8 (1.77) | 7.4 (1.43) | 7.5 (1.48)
Week 14 | 5.0 (2.27) | 3.7 (2.39) | 5.9 (2.09) | 4.4 (2.48)
BASFIb
Baseline | 5.54 (2.17) | 5.35 (2.36) | 6.18 (1.87) | 6.28 (2.03)
Week 14 | 4.21 (2.26) | 3.14 (2.37) | 5.09 (2.21) | 3.98 (2.45)
Inflammationc
Baseline | 6.66 (1.90) | 6.51 (1.99) | 6.75 (1.55) | 6.88 (1.84)
Week 14 | 4.61 (2.13) | 3.40 (2.16) | 5.11 (2.30) | 3.87 (2.50)
hsCRP (mg/L)
Baseline | 11.02 (10.85) | 8.90 (12.42) | 14.71 (17.54) | 15.30 (20.53)
Week 14 | 11.72 (15.93) | 2.23 (3.56) | 15.31 (17.55) | 3.82 (8.26)
Abbreviations: ASAS = Assessment of SpondyloArthritis international Society; BASFI = Bath Ankylosing Spondylitis Functional Index; bDMARD = biologic disease modifying anti-rheumatic drug; hsCRP = high sensitivity C-reactive protein; IR = inadequate responder; PBO = placebo; BASDAI = Bath Ankylosing Spondylitis Disease Activity Index
Results are based on as-observed data from patients who have baseline observation.
a Data shown are mean (standard deviation).
b Numeric rating scale (NRS): 0 = best, 10 = worst
c mean of BASDAI questions 5 and 6 assessing morning stiffness severity and duration: 0 = best, 10 = worst

Figure 5. Percent of Patients Achieving ASAS40 in Trial AS-II*

*Results are based on non-responder imputation in conjunction with multiple imputation.

Other Health-Related Outcomes

In Trial AS-II, patients treated with RINVOQ 15 mg showed significant improvements in health-related quality of life as measured by Ankylosing Spondylitis Quality of Life (ASQoL) compared to placebo at Week 14. In Trial AS-I, improvement in ASQoL compared to placebo was also observed.

Enthesitis

In Trial AS-II, patients with pre-existing enthesitis treated with RINVOQ 15 mg showed significant improvement in enthesitis compared to placebo as measured by change from baseline in Maastricht Ankylosing Spondylitis Enthesitis Score (MASES) at Week 14. In Trial AS-I, improvement in MASES compared to placebo was also observed.

Spinal mobility

In Trial AS-II, patients treated with RINVOQ 15 mg showed significant improvement in spinal mobility compared to placebo as measured by change from baseline in Bath Ankylosing Spondylitis Metrology Index (BASMI) at Week 14. In Trial AS-I, improvement in BASMI compared to placebo was also observed.

14.7 Non-radiographic Axial Spondyloarthritis

The efficacy and safety of RINVOQ 15 mg once daily were assessed in a randomized, double-blind, multicenter, placebo-controlled trial in patients 18 years of age or older with active non-radiographic axial spondyloarthritis. Trial nr-axSpA (NCT04169373) was a 52-week placebo-controlled trial in 314 patients (of which 313 patients received study treatment) with active non-radiographic axial spondyloarthritis with an inadequate response to at least two nonsteroidal anti-inflammatory drugs (NSAIDs) or intolerance to or contraindication for NSAIDs. Patients must have had objective signs of inflammation indicated by elevated C-reactive protein (CRP) (defined as > upper limit of normal), and/or sacroiliitis on magnetic resonance imaging (MRI), and no definitive radiographic evidence of structural damage on sacroiliac joints. Patients had active disease as defined by the Bath Ankylosing Spondylitis Disease Activity Index (BASDAI) ≥4, and a Patient's Assessment of Total Back Pain score ≥ 4 based on a 0 – 10 numerical rating scale (NRS) at the Screening and baseline Visits. At baseline, approximately 29.1% of the patients were on a concomitant cDMARD. 32.9% of the patients had an inadequate response or intolerance to bDMARD therapy. Patients received RINVOQ 15 mg once daily or placebo. The primary endpoint was the proportion of patients achieving an Assessment of SpondyloArthritis international Society 40 (ASAS40) response at Week 14.

Clinical Response

In Trial nr-axSpA, a significantly greater proportion of patients treated with RINVOQ 15 mg achieved an ASAS40 response compared to placebo at Week 14 (Table 32, Figure 6).

Examination of gender, baseline BMI, symptom duration of non-radiographic axial spondyloarthritis, baseline hsCRP, MRI sacroiliitis, and prior use of bDMARDs did not identify differences in response to RINVOQ among these subgroups at Week 14.

Table 32: Clinical Response at Week 14
 | PBO (N=157) | RINVOQ 15 mg (N=156) | Difference from PBO (95% CI)
ASAS40 a (%) | 22.3 | 44.9 | 22.5 (12.4, 32.5)
ASAS20 a (%) | 43.3 | 66.7 | 23.2 (12.6, 33.8)
Abbreviations: ASAS20 (or 40) = Assessment of SpondyloArthritis international Society ≥20% (or ≥40%) improvement; PBO = placebo
a An ASAS20 (ASAS40) response is defined as a ≥20% (≥40%) improvement and an absolute improvement from baseline of ≥1 (≥2) unit(s) (range 0 to 10) in ≥3 of 4 domains (Patient Global, Total Back Pain, Function, and Inflammation), and no worsening in the potential remaining domain (defined as worsening ≥20% and ≥1 unit for ASAS20 or defined as worsening of > 0 units for ASAS40).
For binary endpoints, results are based on non-responder imputation in conjunction with multiple imputation.

Treatment with RINVOQ 15 mg resulted in improvements in the individual components of the ASAS40 response criteria compared to placebo (Table 33).

Table 33: ASAS Components and Other Measures of Disease Activitya
Treatment Group | PBO (N=157) | RINVOQ 15 mg (N=156)
Patient Global Assessment of Disease Activityb
Baseline | 7.30 (1.38) | 6.99 (1.62)
Week 14 | 5.35 (2.31) | 4.16 (2.38)
Total Back Painb
Baseline | 7.29 (1.39) | 7.23 (1.55)
Week 14 | 5.27 (2.36) | 4.29 (2.49)
BASFIb
Baseline | 5.99 (2.14) | 5.89 (2.08)
Week 14 | 4.47 (2.42) | 3.33 (2.39)
Inflammationc
Baseline | 6.68 (1.67) | 6.60 (1.83)
Week 14 | 4.69 (2.36) | 3.48 (2.51)
hsCRP (mg/L)
Baseline | 8.75 (12.91) | 9.93 (16.17)
Week 14 | 7.25 (10.61) | 2.84 (4.90)
Abbreviations: ASAS = Assessment of SpondyloArthritis international Society; BASFI = Bath Ankylosing Spondylitis Functional Index; hsCRP = high sensitivity C-Reactive Protein; PBO = placebo
a Data shown are mean (standard deviation).
b Numeric rating scale (NRS): 0 = best, 10 = worst
c mean of Bath Ankylosing Spondylitis Disease Activity Index (BASDAI) questions 5 and 6 assessing morning stiffness severity and duration: 0 = best, 10 = worst

Figure 6. Percent of Patients Achieving ASAS40*

*Results are based on non-responder imputation in conjunction with multiple imputation.

Other Health-Related Outcomes

Patients treated with RINVOQ 15 mg showed significant improvements in health-related quality of life as measured by Ankylosing Spondylitis Quality of Life (ASQoL) compared to placebo at Week 14.

14.8 Polyarticular Juvenile Idiopathic Arthritis

The efficacy of RINVOQ/RINVOQ LQ in pediatric patients with JIA with active polyarthritis is based on exposure-matched extrapolation of the established efficacy of RINVOQ in rheumatoid arthritis patients. Safety and efficacy of RINVOQ/RINVOQ LQ were also assessed in a multicenter, open-label, single-arm study in 83 children (2 to < 18 years of age) with JIA with active polyarthritis (NCT03725007). The pJIA patient subtypes at study entry included rheumatoid factor negative polyarticular (68.7%), rheumatoid factor positive polyarticular (15.7%), extended oligoarticular (13.3%), and systemic JIA without systemic manifestations (2.4%). All patients received RINVOQ LQ or RINVOQ tablet dosages based on weight for up to 156 weeks. Patients treated with a stable dose of MTX were permitted to enter the study; changes in MTX dose were permitted during the study. Efficacy was assessed as supportive endpoints through Week 48. The efficacy was generally consistent with responses in patients with rheumatoid arthritis.

14.9 Giant Cell Arteritis

The efficacy and safety of RINVOQ 15 mg once daily were assessed in Trial GCA (NCT03725202), a Phase 3 randomized, double-blind, multicenter, placebo-controlled study in patients 50 years of age and older (81.8% were 65 years of age and older, 73.1% were female, 93.7% white) with new-onset or relapsing giant cell arteritis. Trial GCA was a 52-week trial in which 428 patients were randomized in a 2:1:1 ratio and dosed once daily with RINVOQ 15 mg, upadacitinib 7.5 mg, or placebo. All patients received background corticosteroid therapy. The RINVOQ and upadacitinib-treated groups followed a pre-specified corticosteroid taper regimen with the aim to reach 0 mg by 26 weeks, while the placebo-treated group followed a pre-specified corticosteroid taper regimen with the aim to reach 0 mg by 52 weeks. The primary endpoint was the proportion of patients achieving sustained remission at Week 52 as defined by the absence of giant cell arteritis signs and symptoms from Week 12 through Week 52 and adherence to the protocol-defined corticosteroid taper regimen. A key secondary endpoint was the proportion of patients achieving sustained complete remission at Week 52 as defined by the absence of giant cell arteritis signs and symptoms from Week 12 through Week 52, normalization of erythrocyte sedimentation rate and hsCRP from Week 12 through Week 52, and adherence to the protocol-defined corticosteroid taper regimen. The study included a 52-week extension for a total study duration of up to 2 years.

Clinical Response

RINVOQ 15 mg and a 26-week corticosteroid taper showed superiority in achieving corticosteroid-free sustained remission at Week 52 compared to placebo and a 52-week corticosteroid taper (Table 34).

Table 34. Clinical Response in Trial GCA
Treatment Group | PBO + 52-week corticosteroid taper N =112 | RINVOQ 15 mg + 26-week corticosteroid taper N =209 | Treatment Difference vs PBO (95% CI)
Sustained remission at Week 52 | 33 29.0% | 97 46.4% | 17.1% (6.3, 27.8)a
Sustained complete remission at Week 52 | 18 16.1% | 78 37.1% | 20.7% (11.3, 30.2)b
Components of sustained complete remission at Week 52
Absence of GCA signs and symptomsc | 33 29.8% | 97 46.3%
Normalization of ESRd | 27 23.8% | 98 47.0%
Normalization of hsCRPe | 28 25.0% | 110 52.6%
Adherence to protocol-defined corticosteroid taper regimen | 44 39.3% | 122 58.4%
Abbreviations: ESR = erythrocyte sedimentation rate; GCA = giant cell arteritis; hsCRP = high sensitivity C-reactive protein; PBO = placebo
a p≤0.01
b p≤0.001
c Patients who did not have any signs or symptoms of GCA recorded from Week 12 through Week 52
d ESR to ≤ 30 mm/hr (if ESR > 30 mm/hr and elevation is not attributable to GCA, this criterion can still be met) from Week 12 through Week 52
e hsCRP to < 1 mg/dL, without elevation to ≥ 1 mg/dL (on 2 consecutive visits) from Week 12 through Week 52

Treatment with RINVOQ 15 mg and a 26-week corticosteroid taper resulted in improvements in the components of corticosteroid-free sustained complete remission at Week 52 compared to placebo and a 52-week corticosteroid taper (Table 34).

Cumulative Corticosteroid Dose

The total actual cumulative corticosteroid dose was lower in the RINVOQ 15 mg and a 26-week corticosteroid taper arm (mean [SD] 2283.9 [1840.0] mg and median 1615 mg) relative to the placebo and a 52-week corticosteroid taper arm (mean [SD] 3388.3 [1463.1] mg and median 2882 mg).

16 HOW SUPPLIED/STORAGE AND HANDLING

How Supplied

RINVOQ extended-release tablets are supplied as:

- 15 mg: purple, biconvex oblong, with dimensions of 14 x 8 mm, and debossed with ‘a15’ on one side.
  30 tablets in a bottle; NDC: 0074-2306-30
- 30 mg: red, biconvex oblong, with dimensions of 14 x 8 mm, and debossed with ‘a30’ on one side.
  30 tablets in a bottle; NDC: 0074-2310-30
- 45 mg: yellow to mottled yellow, biconvex oblong, with dimensions of 14 x 8 mm, and debossed with ‘a45’ on one side.
  28 tablets in a bottle; NDC: 0074-1043-28

RINVOQ LQ oral solution is supplied as:

- A 1 mg/mL oral solution in HDPE bottles with a child-resistant cap. Each bottle contains a labeled volume of 180 mL of clear, colorless to light yellow solution. The bottle is packaged in a carton with one press-in bottle adapter and one 10 mL oral dosing syringe; NDC: 0074-2320-01

Storage and Handling

RINVOQ extended-release tablets

- Store at 2˚C to 25˚C (36˚F to 77˚F).
- Store in the original bottle in order to protect from moisture.

RINVOQ LQ oral solution

- Store between 2°C to 30°C (36°F to 86°F).
- Discard remaining oral solution 60 days after opening the bottle.

17 PATIENT COUNSELING INFORMATION

Advise the patient and caregiver to read the FDA-approved patient labeling (Medication Guide and Instructions for Use).

Serious Infections

Inform patients that they may be more likely to develop infections when taking RINVOQ/RINVOQ LQ. Instruct patients to contact their healthcare provider immediately during treatment if they develop any signs or symptoms of an infection [see Warnings and Precautions (5.1)].

Advise patients that the risk of herpes zoster is increased in patients taking RINVOQ/RINVOQ LQ and in some cases can be serious [see Warnings and Precautions (5.1)].

Malignancies

Inform patients that RINVOQ/RINVOQ LQ may increase their risk of certain cancers and that periodic skin examinations should be performed while using RINVOQ/RINVOQ LQ.

Advise patients that exposure to sunlight and UV light should be limited by wearing protective clothing and using a broad-spectrum sunscreen [see Warnings and Precautions (5.3)].

Major Adverse Cardiovascular Events

Inform patients that RINVOQ/RINVOQ LQ may increase their risk of major adverse cardiovascular events (MACE) including myocardial infarction, stroke, and cardiovascular death. Instruct all patients, especially current or past smokers or patients with other cardiovascular risk factors, to be alert for the development of signs and symptoms of cardiovascular events [see Warnings and Precautions (5.4)].

Thrombosis

Inform patients that events of deep venous thrombosis and pulmonary embolism have been reported in clinical trials with RINVOQ. Instruct patients to seek immediate medical attention if they develop any signs or symptoms of a DVT or PE [see Warnings and Precautions (5.5)].

Hypersensitivity Reactions

Advise patients to discontinue RINVOQ/RINVOQ LQ and seek immediate medical attention if they develop any signs and symptoms of allergic reactions [see Warnings and Precautions (5.6)].

Gastrointestinal Perforations

Inform patients that gastrointestinal perforations have been reported in clinical trials with RINVOQ and that risk factors include the use of NSAIDs, corticosteroids, or history of diverticulitis. Instruct patients to seek medical care immediately if they experience new onset of abdominal pain, fever, chills, nausea, or vomiting [see Warnings and Precautions (5.7)].

Retinal Detachment

Inform patients that retinal detachment has been reported in clinical trials with RINVOQ. Advise patients to immediately inform their healthcare provider if they develop any sudden changes in vision while receiving RINVOQ/RINVOQ LQ [see Adverse Reactions (6.1)].

Laboratory Abnormalities

Inform patients that RINVOQ/RINVOQ LQ may affect certain lab tests, and that blood tests are required before and during RINVOQ/RINVOQ LQ treatment [see Warnings and Precautions (5.8)].

Vaccinations

Advise patients to avoid use of live vaccines with RINVOQ/RINVOQ LQ. Instruct patients to inform their healthcare practitioner that they are taking RINVOQ/RINVOQ LQ prior to a potential vaccination [see Warnings and Precautions (5.10)].

Embryo-Fetal Toxicity

Advise pregnant women and females of reproductive potential that exposure to RINVOQ/RINVOQ LQ during pregnancy may result in fetal harm. Advise females to inform their healthcare provider of a known or suspected pregnancy [see Warnings and Precautions (5.9) and Use in Specific Populations (8.1)].

Advise females of reproductive potential that effective contraception should be used during treatment and for 4 weeks following the final dose of RINVOQ/RINVOQ LQ [see Use in Specific Populations (8.3)].

Advise women exposed to RINVOQ/RINVOQ LQ during pregnancy that there is a pregnancy surveillance program that monitors pregnancy outcomes [see Use in Specific Populations (8.1)].

Lactation

Advise women not to breastfeed during treatment with RINVOQ/RINVOQ LQ and for 6 days after the last dose [see Use in Specific Populations (8.2)].

Administration

Advise patients that RINVOQ tablets are not substitutable with RINVOQ LQ [see Dosage and Administration (2.2)].

Advise patients not to chew, crush, or split RINVOQ tablets [see Dosage and Administration (2.2)].

For RINVOQ LQ, instruct patients and caregivers to read and follow the Instructions for Use for proper preparation, administration, storage, and disposal [See Dosage and Administration (2.2)].

Advise patients to avoid food or drink containing grapefruit during treatment with RINVOQ/RINVOQ LQ [see Drug Interactions (7.1)].

Medication Residue in Stool

Instruct patients to notify their healthcare provider if they repeatedly notice medication residue (e.g., intact RINVOQ tablet or fragments) in stool or ostomy output [see Warnings and Precautions (5.11)].

Manufactured by: AbbVie Inc., North Chicago, IL 60064, USA
RINVOQ® is a registered trademark of AbbVie Biotechnology Ltd.
©2019-2025 AbbVie Inc.
20095150 October 2025

MEDICATION GUIDE

RINVOQ® (RIN-VOKE)
(upadacitinib)
extended-release tablets, for oral use

RINVOQ® LQ (RIN-VOKE EL-CUE)
(upadacitinib)
oral solution

What is the most important information I should know about RINVOQ/RINVOQ LQ?
RINVOQ/RINVOQ LQ can cause serious side effects, including:
1. Serious Infections.
RINVOQ/RINVOQ LQ is a medicine that affects your immune system. RINVOQ/RINVOQ LQ can lower the ability of your immune system to fight infections. Some people have had serious infections while taking RINVOQ, including tuberculosis (TB), and infections caused by bacteria, fungi, or viruses that can spread throughout the body. Some people have died from these infections.

- Your healthcare provider should test you for TB before starting treatment with RINVOQ/RINVOQ LQ.
- Your healthcare provider should watch you closely for signs and symptoms of TB during treatment with RINVOQ/RINVOQ LQ.
- You should not start taking RINVOQ/RINVOQ LQ if you have any kind of infection unless your healthcare provider tells you it is okay. You may be at a higher risk of developing shingles (herpes zoster).
- Before starting RINVOQ/RINVOQ LQ, tell your healthcare provider if you:
  ○ are being treated for an infection.
  ○ have had an infection that does not go away or that keeps coming back.
  ○ have diabetes, chronic lung disease, HIV, or a weak immune system.
  ○ have TB or have been in close contact with someone with TB.
  ○ have had shingles (herpes zoster).
  ○ have or have had hepatitis B or C.
  ○ live or have lived, or have traveled to certain parts of the country (such as the Ohio and Mississippi River valleys and the Southwest) where there is an increased chance for getting certain kinds of fungal infections. These infections may happen or become more severe if you use RINVOQ/RINVOQ LQ. Ask your healthcare provider if you do not know if you have lived in an area where these infections are common.
  ○ think you have an infection or have symptoms of an infection such as:

- fever, sweating, or chills
- shortness of breath
- warm, red, or painful skin or sores on your body

- muscle aches
- feeling tired
- blood in your phlegm
- diarrhea or stomach pain

- cough
- weight loss
- burning when you urinate or urinating more often than usual

After starting RINVOQ/RINVOQ LQ, call your healthcare provider right away if you have any symptoms of an infection. RINVOQ/RINVOQ LQ can make you more likely to get infections or make worse any infections that you have. If you get a serious infection, your healthcare provider may stop your treatment with RINVOQ/RINVOQ LQ until your infection is controlled.
2. Increased risk of death in people 50 years of age and older who have at least 1 heart disease (cardiovascular) risk factor and are taking a medicine in the class of medicines called Janus kinase (JAK) inhibitors. RINVOQ/RINVOQ LQ is a JAK inhibitor medicine.
3. Cancer and immune system problems.
RINVOQ/RINVOQ LQ may increase your risk of certain cancers by changing the way your immune system works.
Lymphoma and other cancers, including skin cancers can happen in people taking RINVOQ/RINVOQ LQ. People taking a medicine in the class of medicines called Janus kinase (JAK) inhibitors have a higher risk of certain cancers including lymphoma and lung cancer, especially if you are a current or past smoker.
Tell your healthcare provider if you have ever had any type of cancer. Follow your healthcare provider’s advice about having your skin checked for skin cancer during treatment with RINVOQ/RINVOQ LQ. Limit the amount of time you spend in sunlight. Avoid using tanning beds or sunlamps. Wear protective clothing when you are in the sun and use a sunscreen with a high protection factor (SPF 30 and above). This is especially important if your skin is very fair or if you have a family history of skin cancer.
4. Increased risk of major cardiovascular events such as heart attack, stroke or death in people 50 years of age and older who have at least 1 heart disease (cardiovascular) risk factor and taking a medicine in the class of medicines called JAK inhibitors, especially if you are a current or past smoker.
Get emergency help right away if you have any symptoms of a heart attack or stroke while taking RINVOQ/RINVOQ LQ, including:

- discomfort in the center of your chest that lasts for more than a few minutes, or that goes away and comes back
- severe tightness, pain, pressure, or heaviness in your chest, throat, neck, or jaw
- pain or discomfort in your arms, back, neck, jaw, or stomach
- shortness of breath with or without chest discomfort
- breaking out in a cold sweat
- nausea or vomiting
- feeling lightheaded
- weakness in one part or on one side of your body
- slurred speech

5. Blood Clots (thromboses).
Blood clots in the veins of your legs (deep vein thrombosis, DVT) or lungs (pulmonary embolism, PE) and arteries (arterial thrombosis) can happen in some people taking RINVOQ/RINVOQ LQ. This may be life-threatening and cause death. Blood clots in the veins of the legs (DVT) and lungs (PE) have happened more often in people who are 50 years of age and older and with at least 1 heart disease (cardiovascular) risk factor taking a medicine in the class of medicines called Janus kinase (JAK) inhibitors.

- Tell your healthcare provider if you have had blood clots in the veins of your legs or lungs in the past.
- Get medical help right away if you have signs and symptoms of blood clots during treatment with RINVOQ/RINVOQ LQ, including:

○ swelling
○ pain or tenderness in one or both legs

○ sudden unexplained chest or upper back pain
○ shortness of breath or difficulty breathing

6. Allergic reactions. Symptoms such as rash (hives), trouble breathing, feeling faint or dizzy, or swelling of your lips, tongue, or throat, that may mean you are having an allergic reaction have been seen in people taking RINVOQ. Some of these reactions were serious. If any of these symptoms occur during treatment with RINVOQ/RINVOQ LQ, stop taking RINVOQ/RINVOQ LQ and get emergency medical help right away.

7. Tears (perforation) in the stomach or intestines.

- Tell your healthcare provider if you have had diverticulitis (inflammation in parts of the large intestine) or ulcers in your stomach or intestines. Some people taking RINVOQ/RINVOQ LQ can get tears in their stomach or intestines. This happens most often in people who take nonsteroidal anti-inflammatory drugs (NSAIDs) or corticosteroids.
- Get medical help right away if you get stomach-area pain, fever, chills, nausea, or vomiting.

8. Changes in certain laboratory test results.
Your healthcare provider should do blood tests before you start taking RINVOQ/RINVOQ LQ and while you take RINVOQ/RINVOQ LQ to check for the following:

- low neutrophil and lymphocyte counts. Neutrophils and lymphocytes are types of white blood cells that help the body fight off infections.
- low red blood cell counts. Red blood cells carry oxygen. Low red blood cells means you may have anemia, which may make you feel weak and tired.
- increased cholesterol levels. Your healthcare provider should do blood tests to check your cholesterol levels approximately 12 weeks after you start taking RINVOQ/RINVOQ LQ, and as needed.
- elevated liver enzymes. Liver enzymes help to tell if your liver is functioning normally. Elevated liver enzymes may indicate that your healthcare provider needs to do additional tests on your liver.

You should not take RINVOQ/RINVOQ LQ if your neutrophil count, lymphocyte count, or red blood cell count is too low or your liver tests are too high. Your healthcare provider may stop your RINVOQ/RINVOQ LQ treatment for a period of time if needed because of changes in these blood test results.
See “What are the possible side effects of RINVOQ/RINVOQ LQ?” for more information about side effects.

What is RINVOQ/RINVOQ LQ?
RINVOQ/RINVOQ LQ is a prescription medicine that is a Janus kinase (JAK) inhibitor.

- RINVOQ is used to treat adults with moderate to severe rheumatoid arthritis when 1 or more medicines called tumor necrosis factor (TNF) blockers have been used, and did not work well or could not be tolerated.
- RINVOQ is used to treat adults with active psoriatic arthritis when 1 or more medicines called tumor necrosis factor (TNF) blockers have been used, and did not work well or could not be tolerated.
- RINVOQ is used to treat adults and children 12 years of age and older with moderate to severe eczema (atopic dermatitis) that did not respond to previous treatment and their eczema is not well controlled with other pills or injections, including biologic medicines, or the use of other pills or injections is not recommended.
- RINVOQ is used to treat adults with moderate to severe ulcerative colitis when 1 or more medicines called tumor necrosis factor (TNF) blockers have been used, and did not work well or could not be tolerated, or after taking a different injection or pill (systemic therapy) when your healthcare provider does not recommend TNF blockers.
- RINVOQ is used to treat adults with moderate to severe Crohn’s disease when 1 or more medicines called tumor necrosis factor (TNF) blockers have been used, and did not work well or could not be tolerated, or after taking a different injection or pill (systemic therapy) when your healthcare provider does not recommend TNF blockers.
- RINVOQ is used to treat adults with active ankylosing spondylitis when 1 or more medicines called tumor necrosis factor (TNF) blockers have been used, and did not work well or could not be tolerated.
- RINVOQ is used to treat adults with active non-radiographic axial spondyloarthritis with objective signs of inflammation when a tumor necrosis factor (TNF) blocker medicine has been used, and did not work well or could not be tolerated.
- RINVOQ/RINVOQ LQ is used to treat children 2 years of age and older with active polyarticular juvenile idiopathic arthritis (pJIA) when 1 or more medicines called tumor necrosis factor (TNF) blockers have been used, and did not work well or could not be tolerated.
- RINVOQ/RINVOQ LQ is used to treat children 2 to less than 18 years of age with active psoriatic arthritis when 1 or more medicines called tumor necrosis factor (TNF) blockers have been used, and did not work well or could not be tolerated.
- RINVOQ is used to treat adults with giant cell arteritis.

It is not known if RINVOQ/RINVOQ LQ is safe and effective in children with ankylosing spondylitis, non-radiographic axial spondyloarthritis, ulcerative colitis, or Crohn’s disease.
It is not known if RINVOQ is safe and effective in children under 12 years of age with atopic dermatitis.
It is not known if RINVOQ LQ is safe and effective in children with atopic dermatitis.
It is not known if RINVOQ/RINVOQ LQ is safe and effective in children under 2 years of age with pJIA or psoriatic arthritis.

Do not take RINVOQ/RINVOQ LQ if you are allergic to upadacitinib or any of the ingredients in RINVOQ/RINVOQ LQ. See the end of this Medication Guide for a complete list of ingredients in RINVOQ/RINVOQ LQ.
Before taking RINVOQ/RINVOQ LQ, tell your healthcare provider about all of your medical conditions, including if you:

- See “What is the most important information I should know about RINVOQ/RINVOQ LQ?”
- have an infection.
- are a current or past smoker.
- have had a heart attack, other heart problems, or stroke.
- have liver problems.
- have kidney problems.
- have unexplained stomach (abdominal) pain, have a history of diverticulitis or ulcers in your stomach or intestines, or are taking NSAIDs.
- have low red or white blood cell counts.
- have recently received or are scheduled to receive an immunization (vaccine). People who take RINVOQ/RINVOQ LQ should not receive live vaccines.
- are pregnant or plan to become pregnant. Based on animal studies, RINVOQ/RINVOQ LQ may harm your unborn baby.

Females who are able to become pregnant:

- Your healthcare provider will check whether or not you are pregnant before you start treatment with RINVOQ/RINVOQ LQ.
- You should use effective birth control (contraception) to avoid becoming pregnant during treatment with RINVOQ/RINVOQ LQ and for 4 weeks after your last dose of RINVOQ/RINVOQ LQ.
- Tell your healthcare provider if you think you are pregnant or become pregnant during treatment with RINVOQ/RINVOQ LQ.
- There is a pregnancy surveillance program for RINVOQ/RINVOQ LQ. The purpose of the program is to collect information about the health of you and your baby. If you become pregnant while taking RINVOQ/RINVOQ LQ, you are encouraged to report the pregnancy by calling 1-800-633-9110.

- are breastfeeding or plan to breastfeed. RINVOQ/RINVOQ LQ may pass into your breast milk. You and your healthcare provider should decide if you will take RINVOQ/RINVOQ LQ or breastfeed. Do not breastfeed during treatment with RINVOQ/RINVOQ LQ and for 6 days after your last dose of RINVOQ/RINVOQ LQ.

Tell your healthcare provider about all the medicines you take, including prescription and over-the-counter medicines, vitamins, and herbal supplements. RINVOQ/RINVOQ LQ and other medicines may affect each other causing side effects.
Especially tell your healthcare provider if you take:

- medicines for fungal infections (such as ketoconazole, itraconazole, posaconazole or voriconazole) or clarithromycin (for bacterial infections) as these medicines may increase the amount of RINVOQ/RINVOQ LQ in your blood.
- rifampicin (for bacterial infections) or phenytoin (for neurological disorders) as these medicines may decrease the effect of RINVOQ/RINVOQ LQ.
- medicines that affect your immune system (such as azathioprine and cyclosporine) as these medicines may increase your risk of infection.

Ask your healthcare provider or pharmacist, if you are not sure if you are taking any of these medicines.
Know the medicines you take. Keep a list of them to show your healthcare provider and pharmacist when you get a new medicine.

How should I take RINVOQ/RINVOQ LQ?

- Take RINVOQ/RINVOQ LQ exactly as your healthcare provider tells you to use it.
- Take RINVOQ LQ 2 times a day with or without food.
- Take RINVOQ tablets 1 time a day with or without food.
- Swallow RINVOQ tablets whole. Do not split, crush, or chew the tablets.
- RINVOQ LQ is not the same as RINVOQ tablets. Do not switch between RINVOQ LQ and RINVOQ tablets unless the change has been made by your healthcare provider.
- If you take too much RINVOQ/RINVOQ LQ, call your healthcare provider or Poison Help line at 1-800-222-1222, or go to the nearest hospital emergency room right away.

What should I avoid while taking RINVOQ/RINVOQ LQ?
Avoid food or drink containing grapefruit during treatment with RINVOQ/RINVOQ LQ. Eating grapefruit or drinking grapefruit juice may increase the risk of side effects.
What are the possible side effects of RINVOQ/RINVOQ LQ?
RINVOQ/RINVOQ LQ may cause serious side effects, including:

- See “What is the most important information I should know about RINVOQ/RINVOQ LQ?”

The most common side effects of RINVOQ/RINVOQ LQ in people treated for rheumatoid arthritis, psoriatic arthritis, ankylosing spondylitis, non-radiographic axial spondyloarthritis, and polyarticular juvenile idiopathic arthritis include:

• upper respiratory tract infections (common cold, sinus infections)
• shingles (herpes zoster)
• herpes simplex virus infections, including cold sores
• bronchitis

• nausea
• cough
• fever
• acne
• headache

The most common side effects of RINVOQ in people treated for giant cell arteritis include:

• upper respiratory tract infections (common cold, sinus infections
• headache
• tiredness
• swelling of the feet and hands (peripheral edema)

• cough
• low red blood cell count (anemia)
• rash
• shingles (herpes zoster)
• nausea

The most common side effects of RINVOQ in people treated for atopic dermatitis include:

• upper respiratory tract infections (common cold, sinus infections)
• acne
• herpes simplex virus infections, including cold sores
• headache
• increased blood levels of creatine phosphokinase
• cough
• allergic reactions
• inflammation of hair follicles
• nausea

• stomach-area (abdominal) pain
• fever
• increased weight
• shingles (herpes zoster)
• flu
• tiredness
• low white blood cell count (neutropenia)
• muscle pain
• flu-like illness

The most common side effects of RINVOQ in people treated for ulcerative colitis include:

• upper respiratory tract infections (common cold, sinus infections)
• acne
• herpes simplex virus infections, including cold sores
• inflammation of the hair follicles
• rash
• flu

• shingles (herpes zoster)
• increased blood cholesterol levels
• increased blood levels of creatine phosphokinase
• increased liver enzyme levels
• low number of certain types of white blood cells (neutropenia, lymphopenia)
• fever

The most common side effects of RINVOQ in people treated for Crohn’s disease include:

• upper respiratory tract infections (common cold, sinus infections)
• bronchitis
• pneumonia
• flu
• acne
• herpes simplex virus infections, including cold sores
• tiredness
• cough

• fever
• shingles (herpes zoster)
• headache
• increased blood levels of creatine phosphokinase
• increased liver enzyme levels
• low number of red blood cells (anemia)
• low number of white blood cells (neutropenia, leukopenia)
• infection of the stomach and intestine (gastroenteritis)

Separation or tear to the lining of the back part of the eye (retinal detachment) has happened in people with atopic dermatitis treated with RINVOQ. Call your healthcare provider right away if you have any sudden changes in your vision during treatment with RINVOQ/RINVOQ LQ.
Some people taking RINVOQ may see medicine residue (a whole tablet or tablet pieces) in their stool. If this happens, call your healthcare provider.
These are not all the possible side effects of RINVOQ/RINVOQ LQ.
Call your healthcare provider for medical advice about side effects. You may report side effects to FDA at 1-800-FDA-1088.
How should I store RINVOQ/RINVOQ LQ?

- Store RINVOQ tablets between 36°F to 77°F (2°C to 25°C).
- Store RINVOQ tablets in the original bottle to protect from moisture.
- Store RINVOQ LQ between 36°F to 86°F (2°C to 30°C).
- Throw away (discard) remaining RINVOQ LQ 60 days after opening the bottle.
- Keep RINVOQ/RINVOQ LQ and all medicines out of the reach of children.

General information about the safe and effective use of RINVOQ/RINVOQ LQ.
Medicines are sometimes prescribed for purposes other than those listed in a Medication Guide. Do not use RINVOQ/RINVOQ LQ for a condition for which it was not prescribed.
Do not give RINVOQ/RINVOQ LQ to other people, even if they have the same symptoms that you have. It may harm them.
You can ask your pharmacist or healthcare provider for information about RINVOQ/RINVOQ LQ that is written for health professionals.
What are the ingredients in RINVOQ 15 mg tablets?
Active ingredient: upadacitinib
Inactive ingredients: colloidal silicon dioxide, ferrosoferric oxide, hypromellose, iron oxide red, magnesium stearate, mannitol, microcrystalline cellulose, polyvinyl alcohol, polyethylene glycol, talc, tartaric acid and titanium dioxide.
What are the ingredients in RINVOQ 30 mg tablets?
Active ingredient: upadacitinib
Inactive ingredients: colloidal silicon dioxide, hypromellose, iron oxide red, magnesium stearate, mannitol, microcrystalline cellulose, polyvinyl alcohol, polyethylene glycol, talc, tartaric acid and titanium dioxide.
What are the ingredients in RINVOQ 45 mg tablets?
Active ingredient: upadacitinib
Inactive ingredients: colloidal silicon dioxide, hypromellose, iron oxide yellow and iron oxide red, magnesium stearate, mannitol, microcrystalline cellulose, polyvinyl alcohol, polyethylene glycol, talc, tartaric acid and titanium dioxide.
What are the ingredients in RINVOQ LQ?
Active ingredient: upadacitinib
Inactive ingredients: citric acid anhydrous, purified water, sodium benzoate, sodium citrate dihydrate and sucralose.
Manufactured by: AbbVie Inc., North Chicago, IL 60064, USA
RINVOQ® is a registered trademark of AbbVie Biotechnology Ltd.
©2019-2025 AbbVie Inc.
For more information, call 1-800 2-RINVOQ (1-800-274-6867) or go to www.RINVOQ.com.

This Medication Guide has been approved by the U.S. Food and Drug Administration
20095151

Revised: 10/2025

INSTRUCTIONS FOR USE

RINVOQ® LQ [RIN-VOKE EL-CUE]

(upadacitinib)

oral solution

This Instructions for Use contains information on how to prepare and give a dose of RINVOQ LQ oral solution.

Read this Instructions for Use before you give RINVOQ LQ to your child, and each time you get a refill. There may be new information. This information does not take the place of talking to your healthcare provider about your child’s medical condition or treatment.

Important Information You Need to Know Before Giving RINVOQ LQ

Keep the bottle and supplies out of sight and reach of children.

Only use the syringe provided. Do not share the syringe with other people or use it with other medicines.

Call your healthcare provider or 1-800-2-RINVOQ or 1-800-274-6867 if you need help or have any questions about how to give RINVOQ LQ the right way.

Contact your healthcare provider if your child takes too much oral solution or does not receive the full dose.

- Use RINVOQ LQ within 60 days of opening the bottle. To help you remember, write the date you opened the bottle on the carton.
- Do not open a new bottle of RINVOQ LQ until you have finished the previous bottle. Use a new syringe when you open a new bottle.
- RINVOQ LQ oral solution is clear and colorless to light yellow in color.
- Keep these instructions and the carton your RINVOQ LQ oral solution and supplies came in for future use.

Supplies in Each Carton

Figure A

Disposal of RINVOQ LQ

Dispose of (throw away) the syringe and the bottle when you have finished the bottle or 60 days after opening.

- Ask your pharmacist how to properly dispose of (throw away) any unused medicine.
- Rinse syringe then place in household trash.

Preparing RINVOQ LQ

1. Check the prescribed dose.

a. Check your child’s prescribed dose in milliliters (mL) and find this mL marking on the syringe.

b. Only use the syringe provided to give the prescribed dose.

2. Check expiration date.

a. Check the bottle and make sure the expiration date has not passed (see Figure B).

Do not use RINVOQ LQ after the expiration date printed on the carton and the bottle after “EXP.”

Figure B

3. Check supplies.

a. Check the supplies and make sure they are not damaged (see Figure C).

b. Only use the syringe if it is clean and dry.

c. Make sure that the plunger is all the way in the syringe.

Do not use the supplies if they are wet, damaged, or appear to be tampered with.

Figure C

4. Open the bottle.

a. Press down and twist the cap to remove it from the bottle (see Figure D). Do not throw away the cap.

Figure D

5. Insert the adapter (first time only).

a. While holding the bottle firmly, use your thumb to push the adapter all the way down to the rim of the bottle (see Figure E).

Note: You may need to apply pressure to the adapter.

Do not remove adapter after it is inserted.

Figure E

Measuring the Dose

6. Insert the syringe into the bottle then turn it upside down.

a. Insert the tip of the syringe into the adapter.

b. With the syringe attached to the bottle, turn the bottle upside down (see Figure F).

Figure F

7. Draw the oral solution into the syringe.

a. Slowly pull the plunger down (see Figure G).

b. Check the syringe for air bubbles.

Note: You may feel pressure when pulling the plunger.

Figure G

8. Remove large air bubbles (see Figure H).

a. While holding the bottle, flick the sides of the syringe to send large air bubbles to the tip.

b. With the syringe attached to the bottle, move the plunger up and down to return air bubbles back into the bottle.

c. Repeat Step 8 until any large air bubbles are gone.

Note: Small air bubbles are normal.

Figure H

9. Measure the dose.

a. After any large air bubbles are removed, move the plunger until it is even with the marking of the dose (see Figure I).

Figure I

10. Turn the bottle upright, and then remove the syringe.

a. With the syringe attached to the bottle, turn the bottle upright.

b. Hold the middle of the syringe and carefully remove it from the bottle (see Figure J).

Do not touch the plunger to avoid oral solution accidentally coming out of the syringe before you are ready to give the medicine.

Figure J

Giving RINVOQ LQ

11. Check the dose.

a. Check that the syringe has the correct dose of oral solution (see Figure K).

b. Check the syringe for large air bubbles.

c. If the dose is not correct or you see large air bubbles, return to Step 6.

Figure K

12. Give the oral solution.

a. Place the syringe against the inside of the child’s cheek.

b. Push the plunger to give the entire dose into the child’s mouth (see Figure L).

c. Give the child a drink of water.

Note: Oral solution must be given within 1 hour of filling the syringe.

Figure L

Storing RINVOQ LQ

13. Close and store the bottle.

a. With the adapter still inserted in the bottle, screw the cap back on to the bottle to seal it (see Figure M).

b. Store the bottle upright in the carton between uses.

c. Store the bottle in the carton between 36°F to 86°F (2°C to 30°C) in a cool, dark place.

d. Keep the bottle, supplies, and all medicines out of the sight and reach of children.

Figure M

14. Rinse and store the syringe.

a. Remove the plunger from the syringe then rinse both parts with water (see Figure N).

Do not use soap or put the syringe in the dishwasher to clean it.

b. Allow separated parts to air dry on a clean surface.

c. Store the syringe in a clean, dry place.

Figure N

15. When you have finished the bottle, see “Disposal of RINVOQ LQ.”

Manufactured by: AbbVie Inc., North Chicago, IL 60064, USA

RINVOQ® is a registered trademark of AbbVie Biotechnology Ltd.

©2019-2024 AbbVie Inc.

This Instructions for Use has been approved by the U.S. Food and Drug Administration.

Issued: April 2024

20081174 R1

PRINCIPAL DISPLAY PANEL

NDC 0074-2306-30

RINVOQ®

upadacitinib

Extended-Release Tablets

15 mg

RINVOQ and RINVOQ LQ

are NOT substitutable

Dispense in original packaging

FLIP CAP TO CUT FOIL

PEEL BACK FOR INSTRUCTIONS

30 Tablets

Rx only
abbvie

PRINCIPAL DISPLAY PANEL

NDC 0074-2310-30

RINVOQ®

upadacitinib

Extended-Release Tablets

30 mg

RINVOQ and RINVOQ LQ

are NOT substitutable

Dispense in original packaging

FLIP CAP TO CUT FOIL

PEEL BACK FOR INSTRUCTIONS

30 Tablets

Rx only
abbvie

PRINCIPAL DISPLAY PANEL

NDC 0074-1043-28

RINVOQ®

upadacitinib

Extended-Release Tablets

45 mg

RINVOQ and RINVOQ LQ

are NOT substitutable

Dispense with Medication Guide

FLIP CAP TO CUT FOIL

PEEL BACK FOR INSTRUCTIONS

28 Tablets

Rx only
abbvie

PRINCIPAL DISPLAY PANEL

NDC 0074-2320-01

RINVOQ® LQ
Upadacitinib
Oral Solution

1 mg/mL

RINVOQ LQ and RINVOQ
are NOT substitutable.

Insert bottle adapter
on first use.

Do not remove
after insertion.

180 mL per Bottle
Rx Only
abbvie